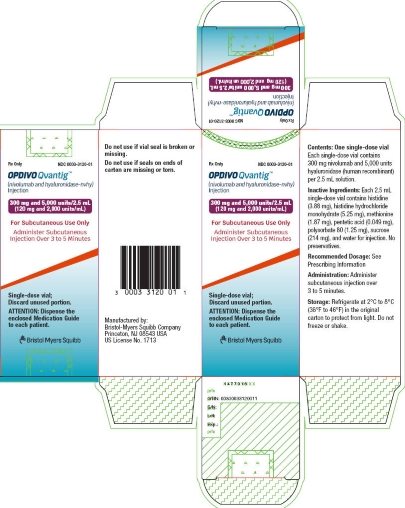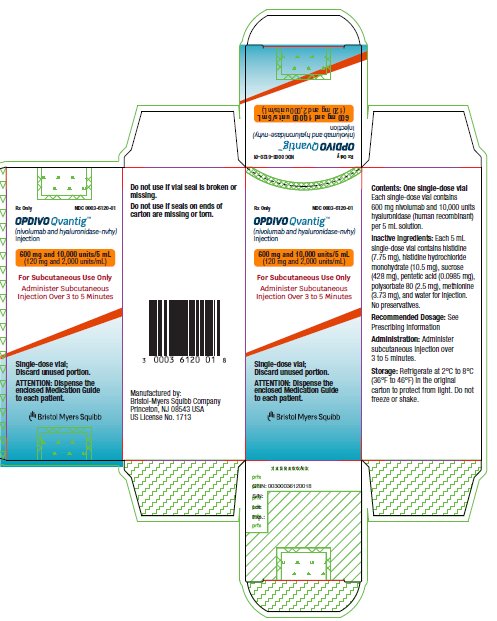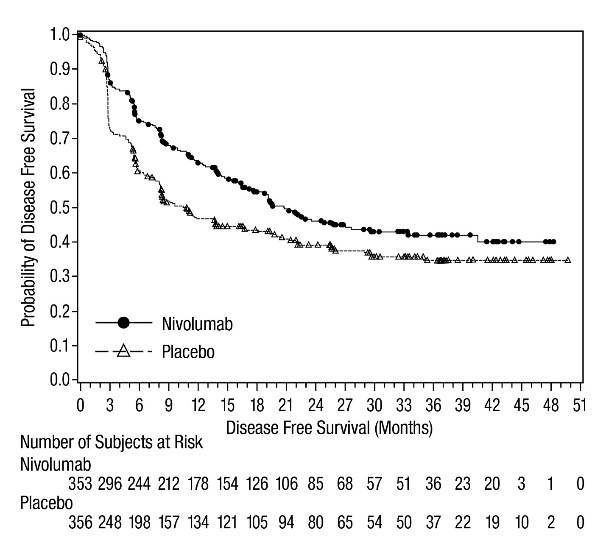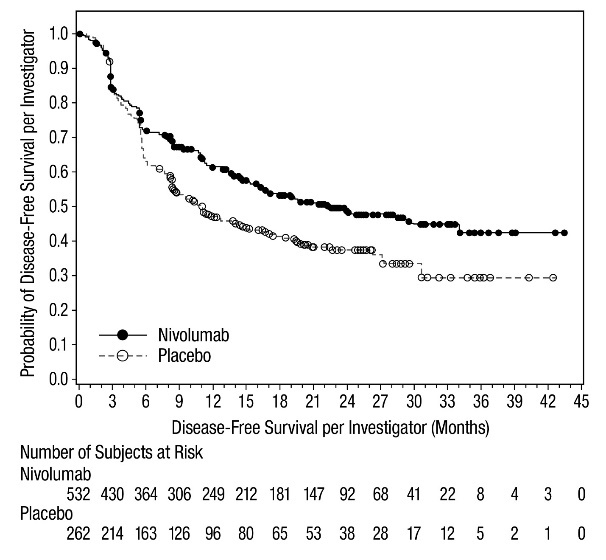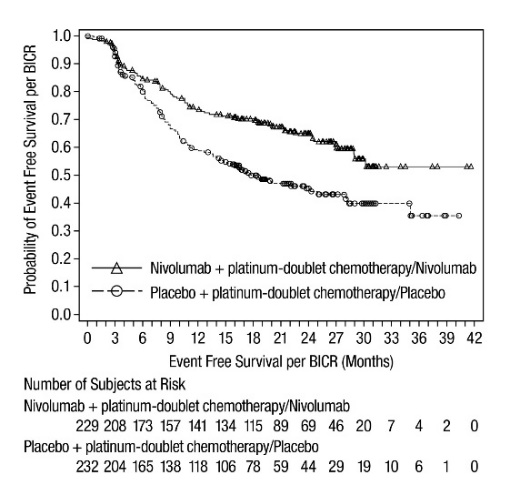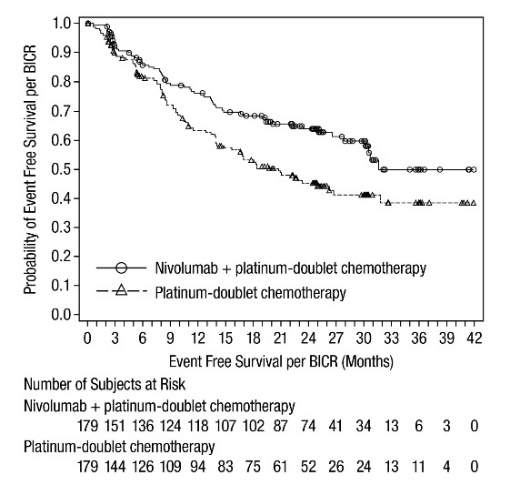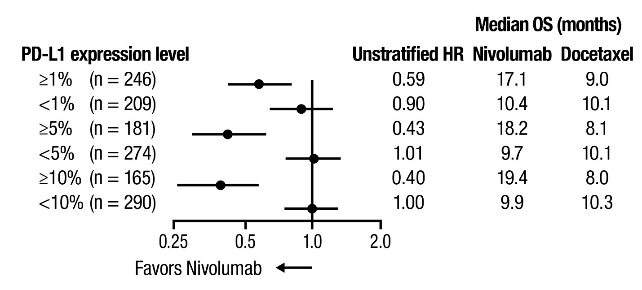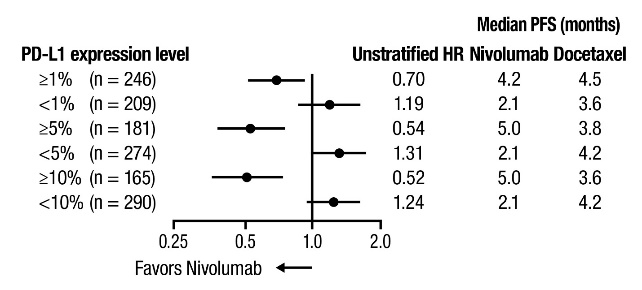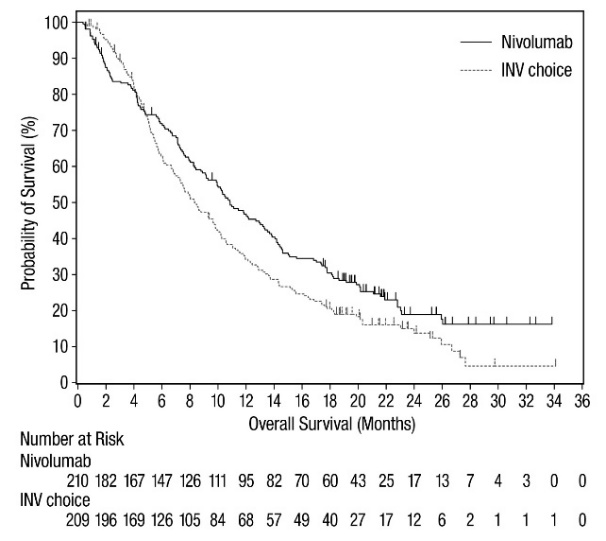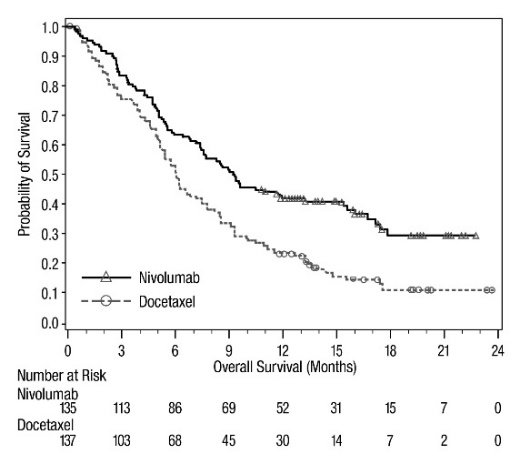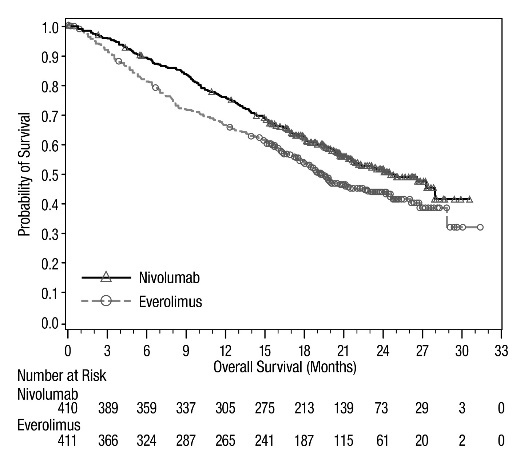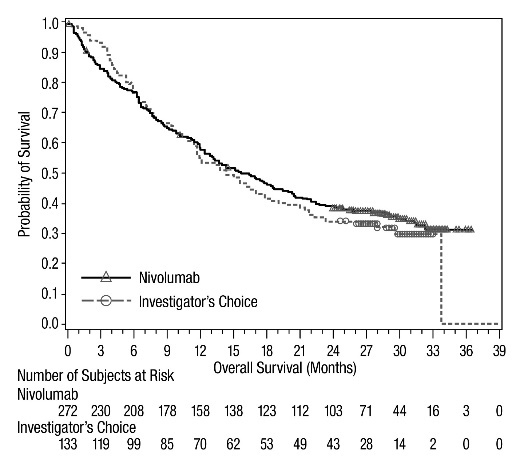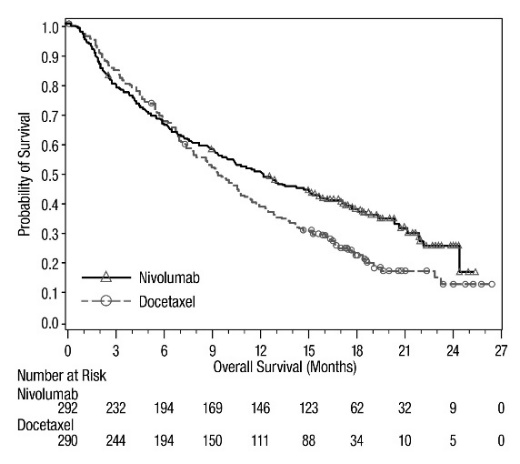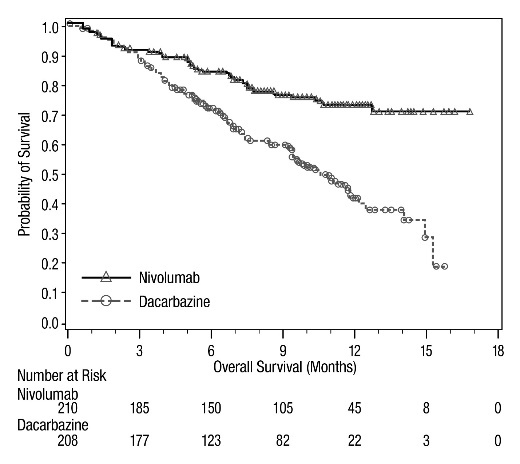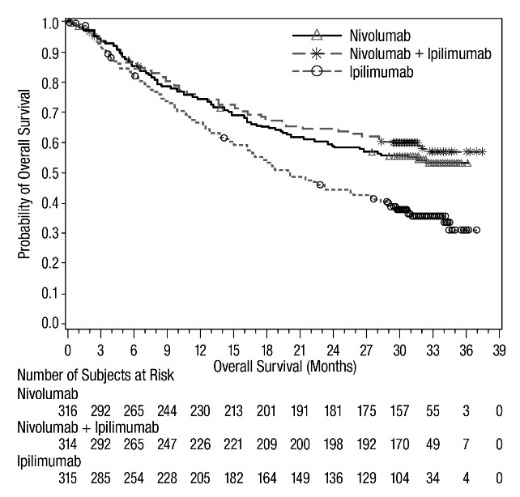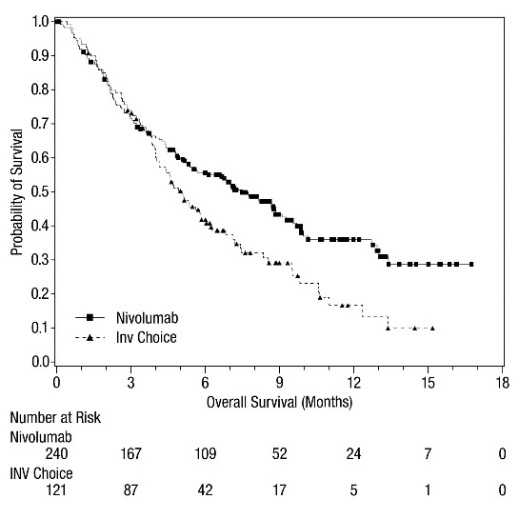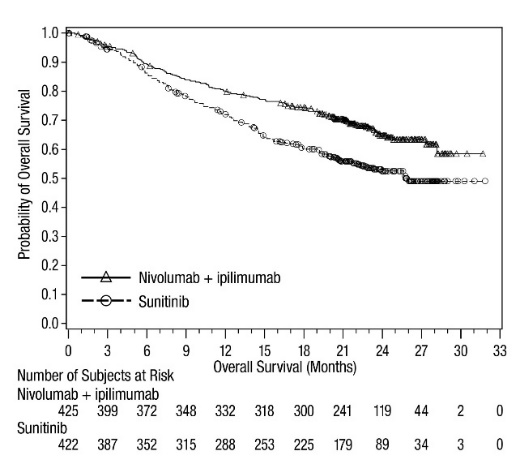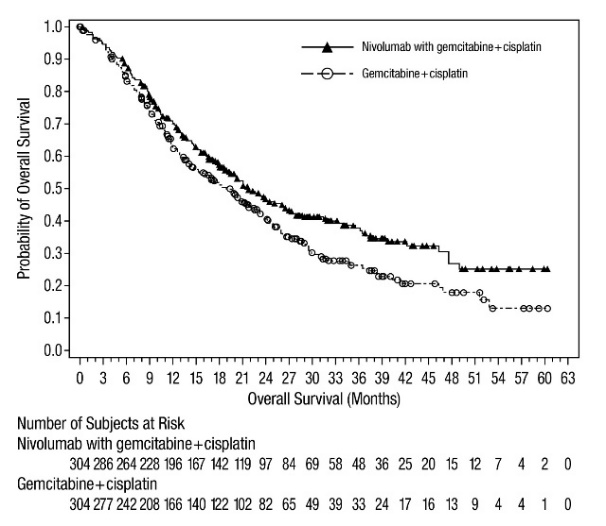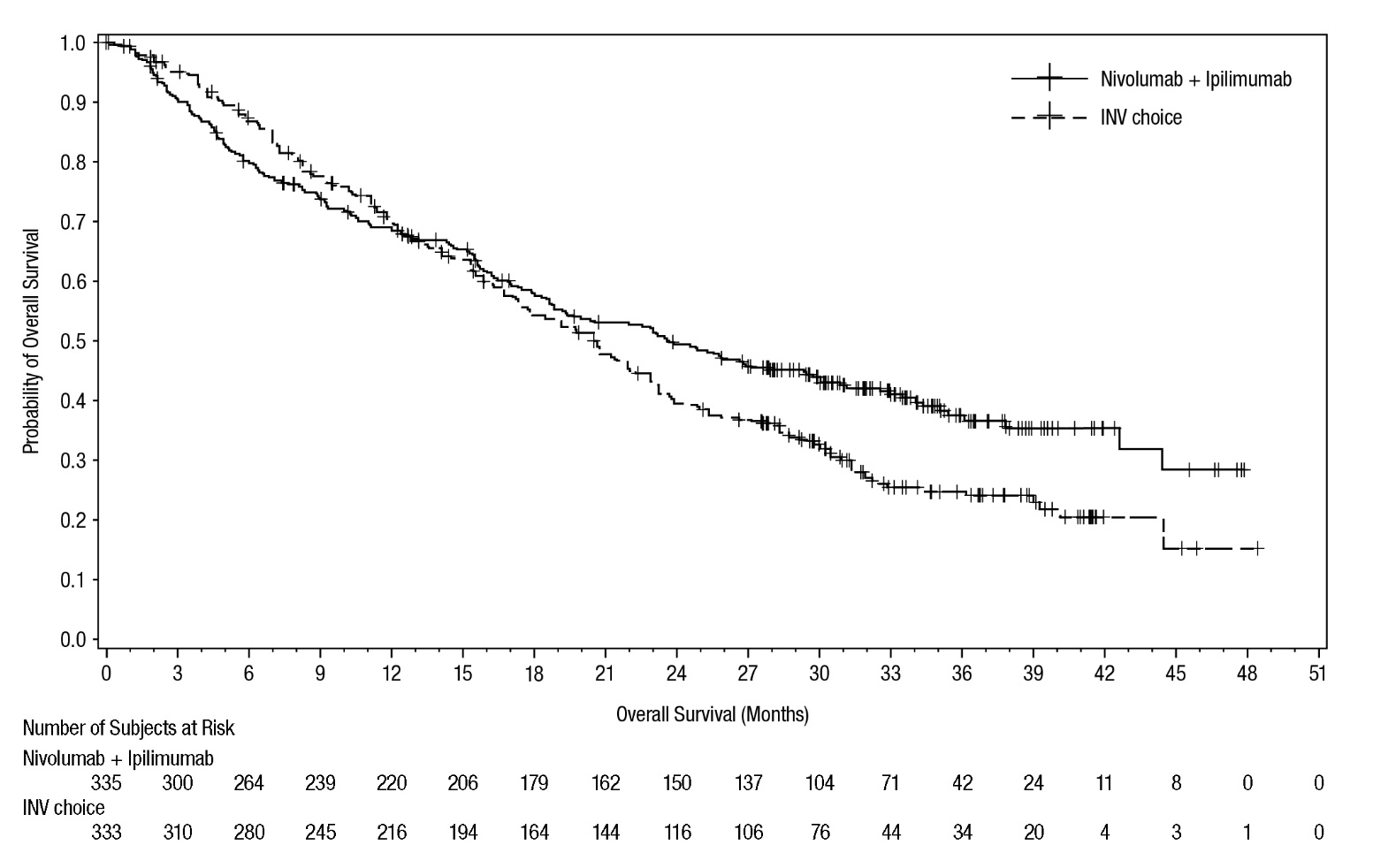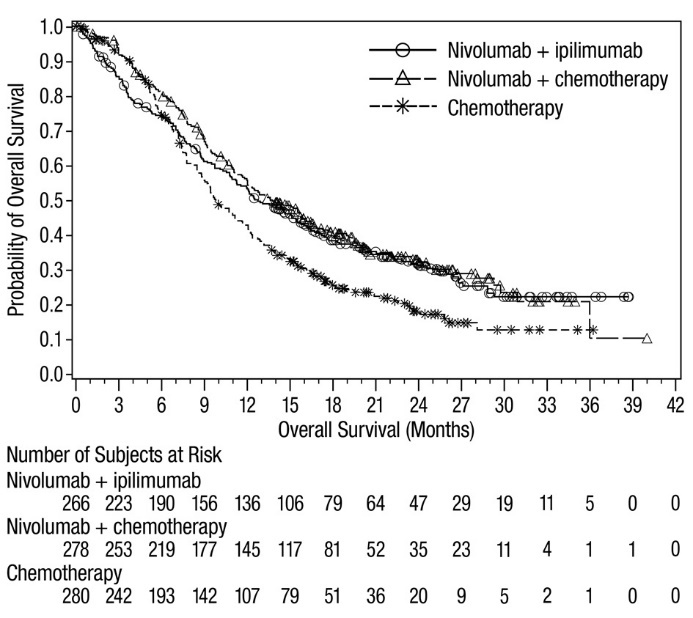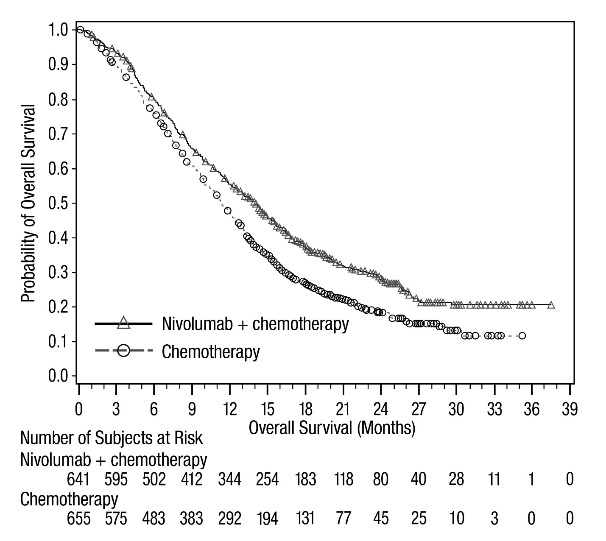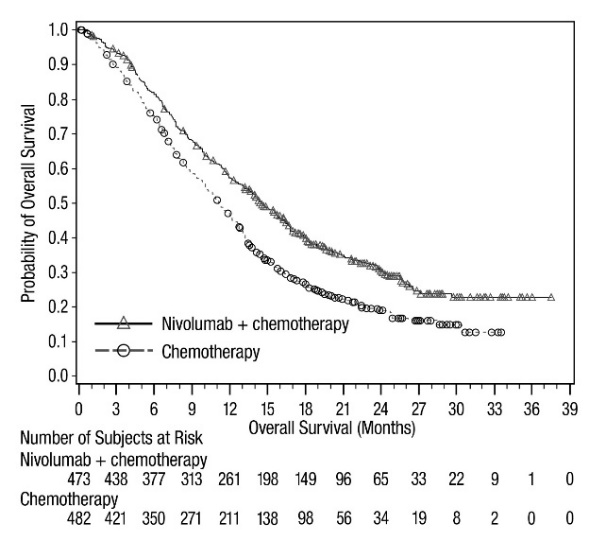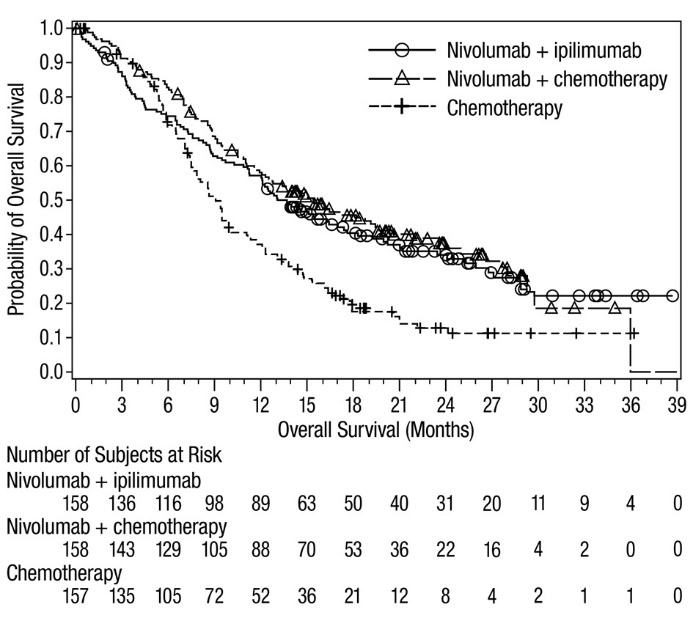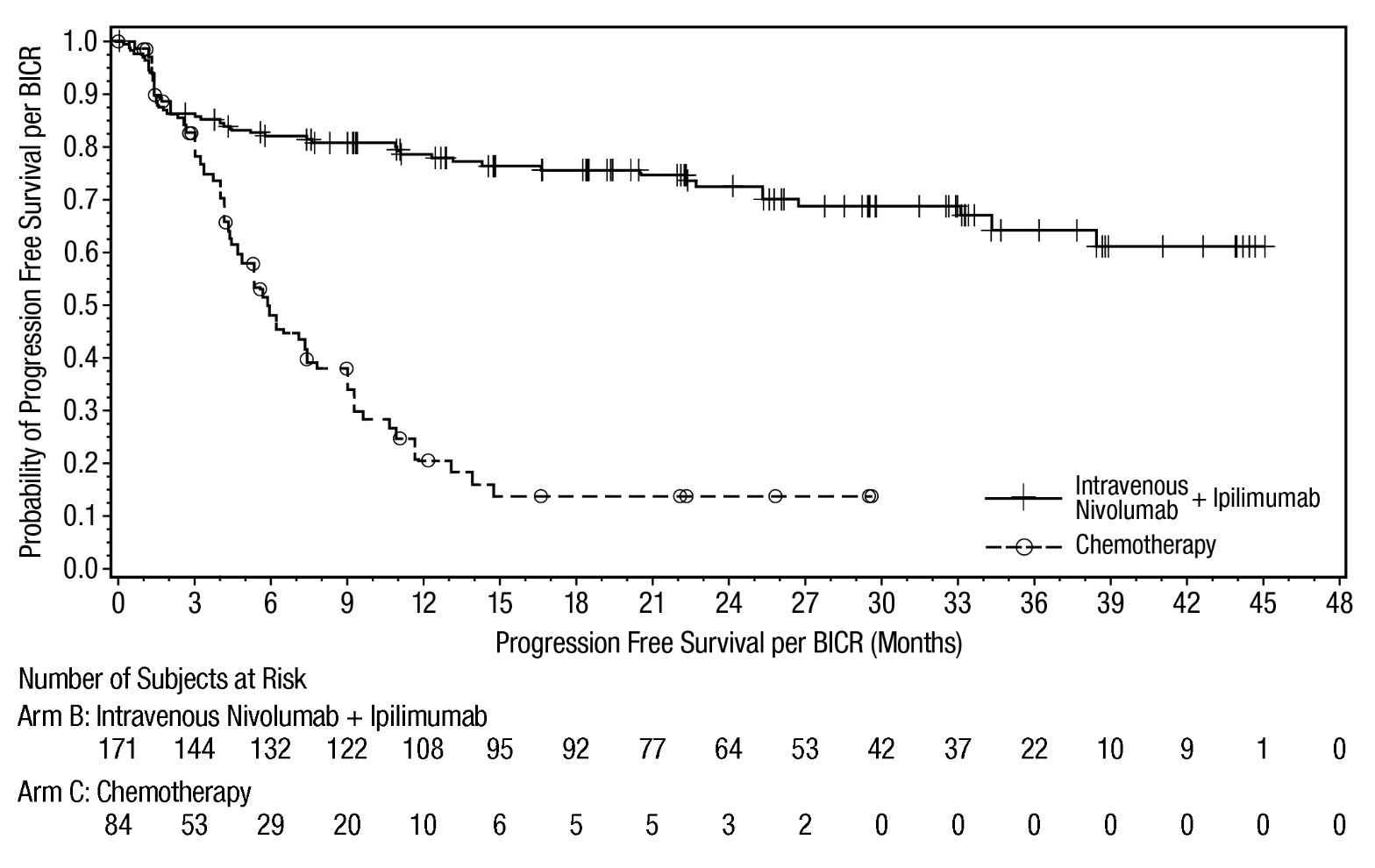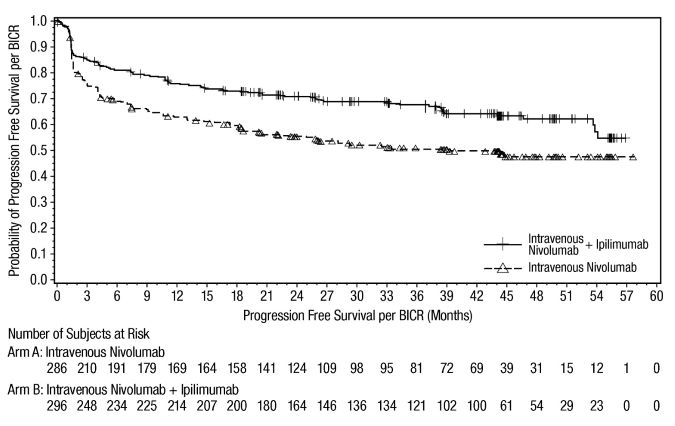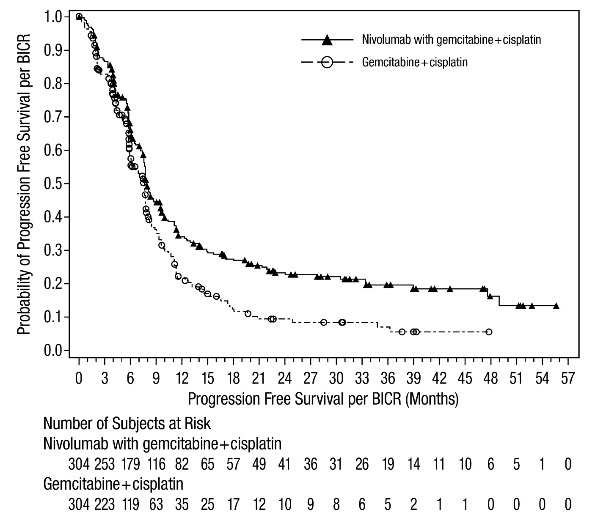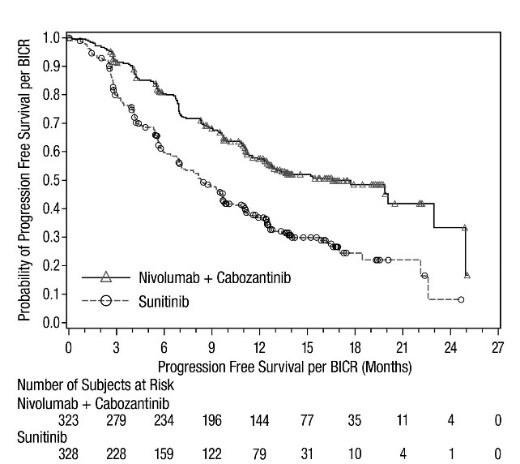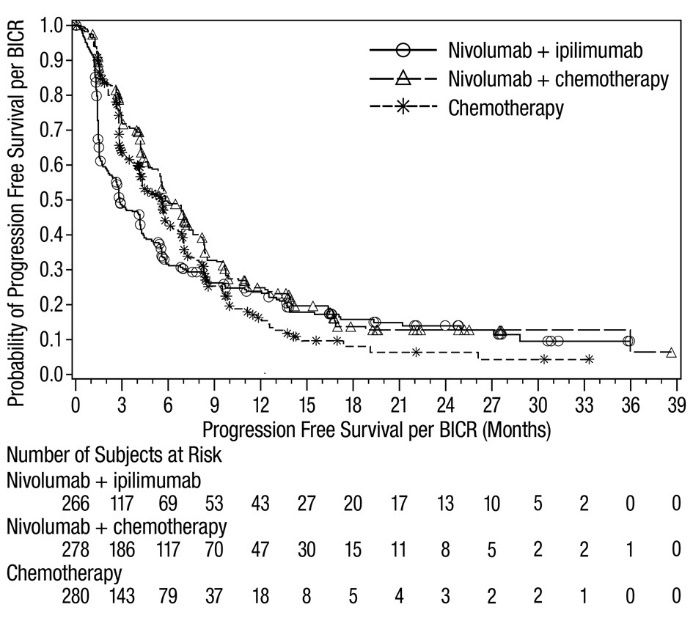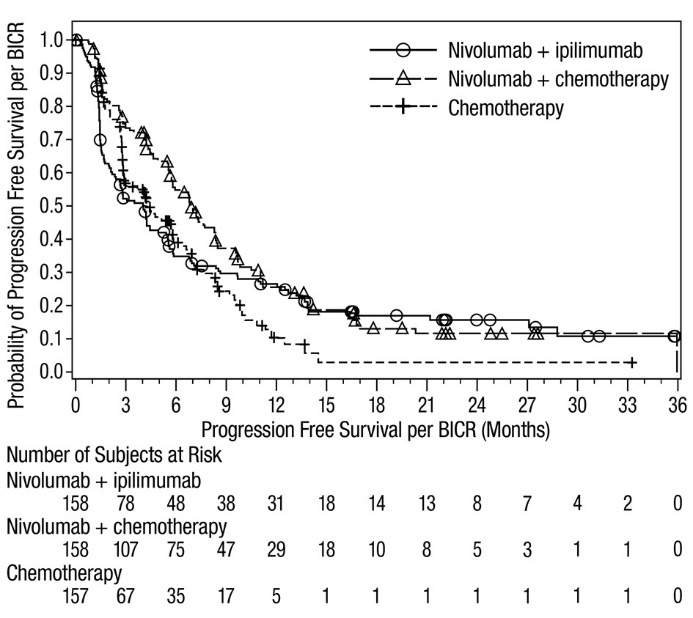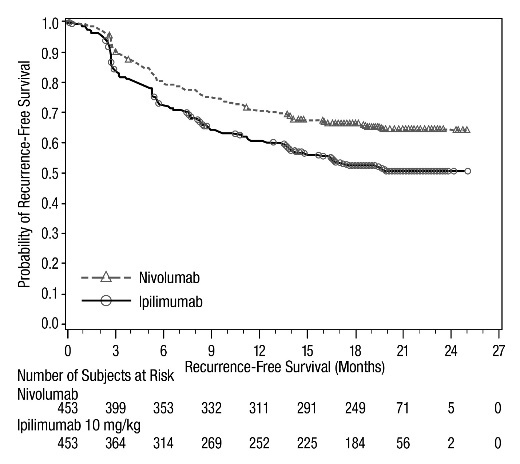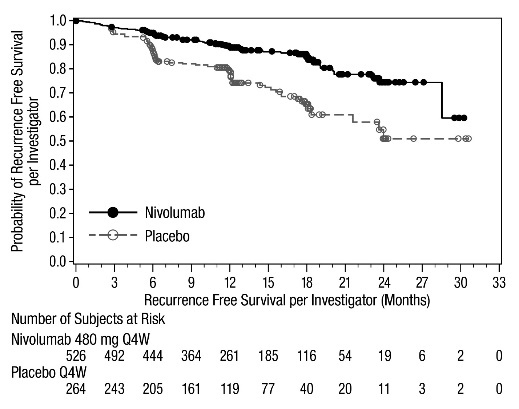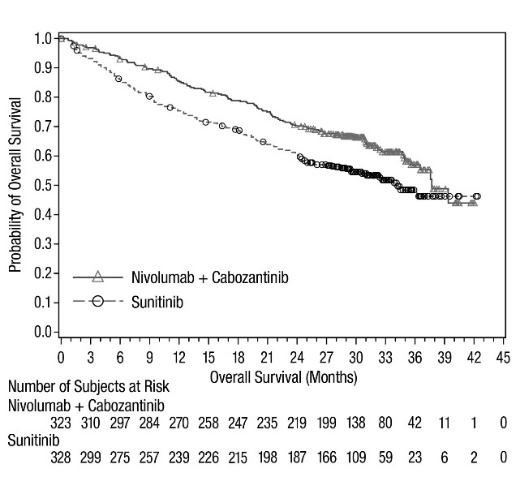 DRUG LABEL: OPDIVO QVANTIG
NDC: 0003-6120 | Form: INJECTION, SOLUTION
Manufacturer: E.R. Squibb & Sons, L.L.C.
Category: prescription | Type: HUMAN PRESCRIPTION DRUG LABEL
Date: 20251124

ACTIVE INGREDIENTS: NIVOLUMAB 120 mg/1 mL; HYALURONIDASE (HUMAN RECOMBINANT) 2000 U/1 mL
INACTIVE INGREDIENTS: HISTIDINE 1.55 mg/1 mL; HISTIDINE HYDROCHLORIDE MONOHYDRATE 2.10 mg/1 mL; METHIONINE 0.746 mg/1 mL; PENTETIC ACID 0.0197 mg/1 mL; POLYSORBATE 80 0.5 mg/1 mL; SUCROSE 85.6 mg/1 mL; SODIUM CHLORIDE; WATER

HIGHLIGHTS OF PRESCRIBING INFORMATION

These highlights do not include all the information needed to use OPDIVO QVANTIG safely and effectively. See full prescribing information for OPDIVO QVANTIG.
OPDIVO QVANTIG™ (nivolumab and hyaluronidase-nvhy) injection, for subcutaneous use.
Initial U.S. Approval: 2024

RECENT MAJOR CHANGES

Indications and Usage (1) | 11/2025
Dosage and Administration (2) | 11/2025

1 INDICATIONS AND USAGE

OPDIVO QVANTIG is a combination of nivolumab, a programmed death receptor-1 (PD-1)-blocking antibody, and hyaluronidase, an endoglycosidase, indicated for the treatment of:

Renal Cell Carcinoma (RCC)

- adult patients with intermediate or poor risk advanced RCC, as a first-line treatment following combination treatment with intravenous nivolumab and ipilimumab. (1.1)
  - Limitations of Use: OPDIVO QVANTIG is not indicated in combination with ipilimumab for the treatment of renal cell carcinoma.
- adult patients with advanced RCC, as a first-line treatment in combination with cabozantinib. (1.1)
- adult patients with advanced RCC who have received prior anti-angiogenic therapy. (1.1)

Melanoma

- adult and pediatric (12 years and older who weigh 30 kg or greater) patients with unresectable or metastatic melanoma. (1.2)
- adult and pediatric (12 years and older who weigh 30 kg or greater) patients with unresectable or metastatic melanoma following combination treatment with intravenous nivolumab and ipilimumab. (1.2)
  - Limitations of Use: OPDIVO QVANTIG is not indicated in combination with ipilimumab for the treatment of unresectable or metastatic melanoma.
- for the adjuvant treatment of adult and pediatric (12 years and older who weigh 30 kg or greater) patients with completely resected Stage IIB, Stage IIC, Stage III, or Stage IV melanoma. (1.3)

Non-Small Cell Lung Cancer (NSCLC)

- adult patients with resectable (tumors ≥4 cm or node positive) NSCLC in the neoadjuvant setting, in combination with platinum-doublet chemotherapy. (1.4)
- adult patients with resectable (tumors ≥4 cm or node positive) NSCLC and no known EGFR mutations or ALK rearrangements, for neoadjuvant treatment, in combination with platinum-doublet chemotherapy, followed by OPDIVO QVANTIG monotherapy as adjuvant treatment after surgery. (1.5)
- adult patients with metastatic NSCLC and progression on or after platinum-based chemotherapy. Patients with EGFR or ALK genomic tumor aberrations should have disease progression on FDA-approved therapy for these aberrations prior to receiving OPDIVO QVANTIG. (1.6)
  - Limitations of Use: OPDIVO QVANTIG is not indicated in combination with ipilimumab for the treatment of metastatic NSCLC.

Squamous Cell Carcinoma of the Head and Neck (SCCHN)

- adult patients with recurrent or metastatic SCCHN with disease progression on or after a platinum-based therapy. (1.7)

Urothelial Carcinoma (UC)

- adjuvant treatment of adult patients with UC who are at high risk of recurrence after undergoing radical resection of UC. (1.8)
- adult patients with unresectable or metastatic urothelial carcinoma, as first-line treatment in combination with cisplatin and gemcitabine. (1.8)
- adult patients with locally advanced or metastatic UC who:
  - have disease progression during or following platinum-containing chemotherapy.
  - have disease progression within 12 months of neoadjuvant or adjuvant treatment with platinum-containing chemotherapy. (1.8)

Colorectal Cancer (CRC)

- adult and pediatric (12 years and older who weigh 30 kg or greater) patients with unresectable or metastatic microsatellite instability-high (MSI-H) or mismatch repair deficient (dMMR) colorectal cancer (CRC), following combination treatment with intravenous nivolumab and ipilimumab. (1.9)
  - Limitations of Use: OPDIVO QVANTIG is not indicated in combination with ipilimumab for the treatment of unresectable or metastatic MSI-H or dMMR CRC.
- adult and pediatric (12 years and older who weigh 30 kg or greater) patients with MSI-H or dMMR metastatic CRC that has progressed following treatment with a fluoropyrimidine, oxaliplatin, and irinotecan. (1.9)
  - Limitations of Use: OPDIVO QVANTIG is not indicated in combination with ipilimumab for the treatment of unresectable or metastatic MSI-H or dMMR CRC.

Hepatocellular Carcinoma (HCC)

- adult patients with unresectable or metastatic HCC, as a first-line treatment following combination treatment with intravenous nivolumab and ipilimumab. (1.10)
- adult patients with unresectable or metastatic HCC, who have been previously treated with sorafenib, following combination treatment with intravenous nivolumab and ipilimumab. (1.10)
  - Limitations of Use: OPDIVO QVANTIG is not indicated in combination with ipilimumab for the treatment of unresectable or metastatic HCC.

Esophageal Cancer

- adult patients with completely resected esophageal or gastroesophageal junction cancer with residual pathologic disease, who have received neoadjuvant chemoradiotherapy (CRT). (1.11)
- adult patients with unresectable advanced or metastatic esophageal squamous cell carcinoma (ESCC) as first-line treatment in combination with fluoropyrimidine- and platinum-containing chemotherapy whose tumors express PD-L1 (≥1). (1.11)
  - Limitations of Use: OPDIVO QVANTIG is not indicated in combination with ipilimumab for the treatment of patients with unresectable advanced or metastatic ESCC.
- adult patients with unresectable advanced, recurrent or metastatic ESCC after prior fluoropyrimidine- and platinum-based chemotherapy. (1.11)

Gastric Cancer, Gastroesophageal Junction Cancer, and Esophageal Adenocarcinoma

- adult patients with advanced or metastatic gastric cancer, gastroesophageal junction cancer, and esophageal adenocarcinoma whose tumors express PD-L1 (≥1) in combination with fluoropyrimidine- and platinum-containing chemotherapy. (1.12)

2 DOSAGE AND ADMINISTRATION

- OPDIVO QVANTIG has different dosage and administration instructions than intravenous nivolumab products.
- OPDIVO QVANTIG is for subcutaneous use only in the abdomen or thigh.
- OPDIVO QVANTIG is to be administered by a healthcare professional only. (2.1)

OPDIVO QVANTIG is for subcutaneous use only.

- Administer by subcutaneous injection over 3 to 5 minutes. (2.3)
- Renal cell carcinoma
  - 600 mg/10,000 units every 2 weeks or 1,200 mg/20,000 units every 4 weeks. (2.3)
  - 600 mg/10,000 units every 2 weeks or 1,200 mg/20,000 units every 4 weeks administered in combination with cabozantinib 40 mg once daily without food. (2.3)
- Melanoma
  - Adult and pediatric patients (12 years and older) who weigh 40 kg or greater: 600 mg/10,000 units every 2 weeks or 1,200 mg/20,000 units every 4 weeks. (2.3)
  - Pediatric patients (12 years and older) who weigh 30 kg or greater but less than 40 kg: 300 mg/5,000 units every 2 weeks or 600 mg/10,000 units every 4 weeks. (2.3)
- Neoadjuvant treatment of resectable (tumors ≥4 cm or node positive) non-small cell lung cancer
  - 900 mg/15,000 units with platinum-doublet chemotherapy on the same day every 3 weeks for 3 cycles. (2.3)
- Neoadjuvant and adjuvant treatment of resectable non-small cell lung cancer
  - 900 mg/15,000 units with platinum-doublet chemotherapy on the same day every 3 weeks for up to 4 cycles, then continued as single-agent OPDIVO QVANTIG 1,200 mg/20,000 units every 4 weeks after surgery for up to 13 cycles (~1 year). (2.3)
- Metastatic non-small cell lung cancer
  - 600 mg/10,000 units every 2 weeks or 1,200 mg/20,000 units every 4 weeks. (2.3)
- Squamous cell carcinoma of the head and neck
  - 600 mg/10,000 units every 2 weeks or 1,200 mg/20,000 units every 4 weeks. (2.3)
- Urothelial carcinoma
  - 600 mg/10,000 units every 2 weeks or 1,200 mg/20,000 units every 4 weeks. (2.3)
- First-line unresectable or metastatic urothelial carcinoma
  - 900 mg/15,000 units every 3 weeks with cisplatin and gemcitabine on the same day for up to 6 cycles, then 600 mg/10,000 units every 2 weeks or 1,200 mg/20,000 units every 4 weeks. (2.3)
- MSI-H or dMMR metastatic Colorectal cancer
  - Adult and pediatric patients weighing 40 kg or greater: 600 mg/10,000 units every 2 weeks or 1,200 mg/20,000 units every 4 weeks. (2.3)
  - Pediatric patients weighing 30 kg or greater but less than 40 kg: 300 mg/5,000 units every 2 weeks or 600 mg/10,000 units every 4 weeks. (2.3)
- Hepatocellular carcinoma
  - 600 mg/10,000 units every 2 weeks or 1,200 mg/20,000 units every 4 weeks. (2.3)
- Esophageal cancer
  - 600 mg/10,000 units every 2 weeks or 1,200 mg/20,000 units every 4 weeks. (2.3)
  - 600 mg/10,000 units every 2 weeks or 1,200 mg/20,000 units every 4 weeks administered in combination with fluoropyrimidine- and platinum-containing chemotherapy. (2.3)
- Gastric Cancer, Gastroesophageal Junction Cancer, and Esophageal Adenocarcinoma
  - 600 mg/10,000 units every 2 weeks in combination with fluoropyrimidine- and platinum-containing chemotherapy every 2 weeks. (2.3)
  - 900 mg/15,000 units every 3 weeks with fluoropyrimidine- and platinum-containing chemotherapy every 3 weeks. (2.3)
- See full Prescribing Information for preparation and administration instructions and dosage modifications for adverse reactions.

3 DOSAGE FORMS AND STRENGTHS

- Injection: 300 mg nivolumab and 5,000 units hyaluronidase per 2.5 mL (120 mg/2,000 units per mL) in a single-dose vial. (3)
- Injection: 600 mg nivolumab and 10,000 units hyaluronidase per 5 mL (120 mg/2,000 units per mL) in a single-dose vial. (3)

4 CONTRAINDICATIONS

- None. (4)

5 WARNINGS AND PRECAUTIONS

- Immune-Mediated Adverse Reactions: (5.1)
  - Immune-mediated adverse reactions, which may be severe or fatal, can occur in any organ system or tissue, including the following: immune-mediated pneumonitis, immune-mediated colitis, immune-mediated hepatitis and hepatotoxicity, immune-mediated endocrinopathies, immune-mediated dermatologic adverse reactions, and immune-mediated nephritis and renal dysfunction.
  - Monitor for early identification and management. Evaluate liver enzymes, creatinine, and thyroid function at baseline and periodically during treatment.
  - Withhold or permanently discontinue based on severity and type of reaction. (2.4)
- Complications of allogeneic HSCT: Fatal and other serious complications can occur in patients who receive allogeneic HSCT before or after being treated with a PD-1/PD-L1 blocking antibody. (5.2)
- Embryo-Fetal toxicity: Can cause fetal harm. Advise females of reproductive potential of potential risk to a fetus and to use effective contraception. (5.3, 8.1, 8.3)
- Treatment of patients with multiple myeloma with a PD-1 or PD-L1 blocking antibody in combination with a thalidomide analogue plus dexamethasone is not recommended outside of controlled clinical trials. (5.4)

6 ADVERSE REACTIONS

- Most common adverse reactions (≥10%) with OPDIVO QVANTIG as monotherapy in patients with Renal Cell Carcinoma were: musculoskeletal pain, fatigue, pruritus, rash, hypothyroidism, diarrhea, cough, and abdominal pain. (6.1)
- Safety of OPDIVO QVANTIG for the following indications is based on safety of intravenous nivolumab in these populations. The most common adverse reactions with intravenous nivolumab for these indications are presented below.
- As monotherapy for the treatment of advanced renal cell carcinoma; adjuvant treatment of completely resected Stage IIB, IIC, III, or IV melanoma; unresectable or metastatic melanoma; adjuvant treatment of NSCLC, metastatic NSCLC; squamous cell carcinoma of the head and neck; urothelial carcinoma; MSI-H or dMMR mCRC; hepatocellular carcinoma; esophageal cancer: fatigue, rash, musculoskeletal pain, pruritus, diarrhea, nausea, asthenia, cough, dyspnea, constipation, decreased appetite, back pain, arthralgia, upper respiratory tract infection, pyrexia, headache, abdominal pain, vomiting, and urinary tract infection. (6.1)
- In combination with cabozantinib for the first-line treatment of advanced renal cell carcinoma: diarrhea, fatigue, hepatotoxicity, palmar-plantar erythrodysesthesia syndrome, stomatitis, rash, hypertension, hypothyroidism, musculoskeletal pain, decreased appetite, nausea, dysgeusia, abdominal pain, cough, and upper respiratory tract infection. (6.1)
- In combination with platinum-doublet chemotherapy for the neoadjuvant treatment of NSCLC: nausea, constipation, fatigue, decreased appetite, and rash. (6.1)
- In combination with cisplatin and gemcitabine for the treatment of urothelial cancer: nausea, fatigue, musculoskeletal pain, constipation, decreased appetite, rash, vomiting, and peripheral neuropathy. (6.1)
- In combination with fluoropyrimidine- and platinum- containing chemotherapy for the treatment of esophageal cancer and gastric cancer: nausea, peripheral neuropathy, decreased appetite, fatigue, constipation, stomatitis, diarrhea, vomiting, abdominal pain, and musculoskeletal pain. (6.1)

To report SUSPECTED ADVERSE REACTIONS, contact Bristol-Myers Squibb at 1-800-721-5072 or FDA at 1-800-FDA-1088 or www.fda.gov/medwatch.

8 USE IN SPECIFIC POPULATIONS

- Lactation: Advise not to breastfeed. (8.2)

FULL PRESCRIBING INFORMATION

1 INDICATIONS AND USAGE

1.1 Advanced Renal Cell Carcinoma

OPDIVO QVANTIG™, as monotherapy, is indicated for the first-line treatment of adult patients with intermediate or poor risk advanced renal cell carcinoma (RCC) following treatment with intravenous nivolumab and ipilimumab combination therapy.

Limitations of Use: OPDIVO QVANTIG is not indicated in combination with ipilimumab for the treatment of renal cell carcinoma.

OPDIVO QVANTIG, in combination with cabozantinib, is indicated for the first-line treatment of adult patients with advanced RCC.

OPDIVO QVANTIG, as monotherapy, is indicated for the treatment of adult patients with advanced RCC who have received prior anti-angiogenic therapy.

1.2 Unresectable or Metastatic Melanoma

OPDIVO QVANTIG, as monotherapy, is indicated for the treatment of adult and pediatric patients 12 years and older who weigh 30 kg or greater with unresectable or metastatic melanoma.

OPDIVO QVANTIG, as monotherapy, is indicated for the treatment of adult and pediatric patients 12 years and older who weigh 30 kg or greater with unresectable or metastatic melanoma following treatment with intravenous nivolumab and ipilimumab combination therapy.

Limitations of Use: OPDIVO QVANTIG is not indicated in combination with ipilimumab for the treatment of unresectable or metastatic melanoma.

1.3 Adjuvant Treatment of Melanoma

OPDIVO QVANTIG, as monotherapy, is indicated for the adjuvant treatment of adult and pediatric patients 12 years and older who weigh 30 kg or greater with completely resected Stage IIB, Stage IIC, Stage III, or Stage IV melanoma.

1.4 Neoadjuvant Treatment of Resectable Non-Small Cell Lung Cancer

OPDIVO QVANTIG, in combination with platinum-doublet chemotherapy, is indicated as neoadjuvant treatment of adult patients with resectable (tumors ≥4 cm or node positive) non-small cell lung cancer (NSCLC).

1.5 Neoadjuvant and Adjuvant Treatment of Resectable Non-Small Cell Lung Cancer

OPDIVO QVANTIG, in combination with platinum-doublet chemotherapy, is indicated for the neoadjuvant treatment of adult patients with resectable (tumors ≥4 cm or node positive) NSCLC and no known epidermal growth factor receptor (EGFR) mutations or anaplastic lymphoma kinase (ALK) rearrangements, followed by OPDIVO QVANTIG as monotherapy in the adjuvant setting after surgical resection.

1.6 Metastatic Non-Small Cell Lung Cancer

OPDIVO QVANTIG, as monotherapy, is indicated for the treatment of adult patients with metastatic non-small cell lung cancer (NSCLC) with progression on or after platinum-based chemotherapy. Patients with EGFR or ALK genomic tumor aberrations should have disease progression on FDA-approved therapy for these aberrations prior to receiving OPDIVO QVANTIG.

Limitations of Use: OPDIVO QVANTIG is not indicated in combination with ipilimumab for the treatment of metastatic NSCLC.

1.7 Squamous Cell Carcinoma of the Head and Neck

OPDIVO QVANTIG, as monotherapy, is indicated for the treatment of adult patients with recurrent or metastatic squamous cell carcinoma of the head and neck (SCCHN) with disease progression on or after platinum-based therapy.

1.8 Urothelial Carcinoma

OPDIVO QVANTIG, as monotherapy, is indicated for the adjuvant treatment of adult patients with urothelial carcinoma (UC) who are at high risk of recurrence after undergoing radical resection of UC.

OPDIVO QVANTIG, in combination with cisplatin and gemcitabine, is indicated for the first-line treatment of adult patients with unresectable or metastatic UC.

OPDIVO QVANTIG, as monotherapy, is indicated for the treatment of adult patients with locally advanced or metastatic UC who:

- have disease progression during or following platinum-containing chemotherapy.
- have disease progression within 12 months of neoadjuvant or adjuvant treatment with platinum-containing chemotherapy.

1.9 Microsatellite Instability-High or Mismatch Repair Deficient Metastatic Colorectal Cancer

OPDIVO QVANTIG, as monotherapy, is indicated for the treatment of adult and pediatric patients 12 years and older who weigh 30 kg or greater with unresectable or metastatic microsatellite instability-high (MSI-H) or mismatch repair deficient (dMMR) colorectal cancer (CRC) following treatment with intravenous nivolumab and ipilimumab combination therapy.

OPDIVO QVANTIG, as monotherapy, is indicated for the treatment of adult and pediatric patients 12 years and older who weigh 30 kg or greater, with MSI-H or dMMR metastatic CRC that has progressed following treatment with a fluoropyrimidine, oxaliplatin, and irinotecan.

Limitations of Use: OPDIVO QVANTIG is not indicated in combination with ipilimumab for the treatment of unresectable or metastatic MSI-H or dMMR CRC.

1.10 Hepatocellular Carcinoma

- OPDIVO QVANTIG, as monotherapy, is indicated for the first-line treatment of adult patients with unresectable or metastatic hepatocellular carcinoma (HCC) following treatment with intravenous nivolumab and ipilimumab combination therapy.
- OPDIVO QVANTIG, as monotherapy, is indicated for the treatment of adult patients with unresectable or metastatic hepatocellular carcinoma (HCC) who have been previously treated with sorafenib following treatment with intravenous nivolumab and ipilimumab combination therapy.

Limitations of Use: OPDIVO QVANTIG is not indicated in combination with ipilimumab for the treatment of patients with unresectable or metastatic HCC.

1.11 Esophageal Cancer

OPDIVO QVANTIG as monotherapy, is indicated for the adjuvant treatment of completely resected esophageal or gastroesophageal junction cancer with residual pathologic disease in adult patients who have received neoadjuvant chemoradiotherapy (CRT).

OPDIVO QVANTIG, in combination with fluoropyrimidine- and platinum-containing chemotherapy, is indicated for the first-line treatment of adult patients with unresectable advanced or metastatic esophageal squamous cell carcinoma (ESCC) whose tumors express PD-L1 (≥1) [see Dosage and Administration (2.2)].

Limitations of Use: OPDIVO QVANTIG is not indicated in combination with ipilimumab for the treatment of patients with unresectable advanced or metastatic ESCC.

OPDIVO QVANTIG as monotherapy, is indicated for the treatment of adult patients with unresectable advanced, recurrent, or metastatic ESCC after prior fluoropyrimidine- and platinum-based chemotherapy.

1.12 Gastric Cancer, Gastroesophageal Junction Cancer, and Esophageal Adenocarcinoma

OPDIVO QVANTIG, in combination with fluoropyrimidine- and platinum-containing chemotherapy, is indicated for the treatment of adult patients with advanced or metastatic gastric cancer, gastroesophageal junction cancer, and esophageal adenocarcinoma whose tumors express PD-L1 (≥1) [see Dosage and Administration (2.2)].

2 DOSAGE AND ADMINISTRATION

2.1 Important Dosage and Administration Information

OPDIVO QVANTIG has different dosage and administration instructions than intravenously administered nivolumab products [see Dosage and Administration (2.5)].

OPDIVO QVANTIG is for subcutaneous use only in the abdomen or thigh. Do not administer intravenously.

OPDIVO QVANTIG is to be administered by a healthcare professional only.

Adult patients currently receiving intravenous nivolumab as a single agent, or in combination with chemotherapy or cabozantinib, may switch to subcutaneous OPDIVO QVANTIG at their next scheduled dose.

2.2 Patient Selection

Esophageal Cancer

Select patients with unresectable advanced or metastatic ESCC for treatment with OPDIVO QVANTIG in combination with fluoropyrimidine- and platinum-containing chemotherapy based on PD-L1 expression [see Clinical Studies (14.11)].

- An FDA-approved companion diagnostic for the detection of PD-L1 expression in patients with advanced or metastatic ESCC is not available.

Gastric Cancer, Gastroesophageal Junction Cancer, and Esophageal Adenocarcinoma

Select patients with advanced or metastatic gastric cancer, gastroesophageal junction cancer, and esophageal adenocarcinoma for treatment with OPDIVO QVANTIG in combination with fluoropyrimidine-and platinum-containing chemotherapy based on PD-L1 expression [see Clinical Studies (14.12)].

- An FDA-approved companion diagnostic for the detection of PD-L1 expression in patients with advanced or metastatic gastric cancer, gastroesophageal junction cancer, and esophageal adenocarcinoma is not available.

2.3 Recommended Dosage

The recommended dosages of OPDIVO QVANTIG as monotherapy are presented in Table 1.

Administer OPDIVO QVANTIG as a subcutaneous injection over 3 to 5 minutes [see Dosage and Administration (2.5)].

Table 1: Recommended Dosages for OPDIVO QVANTIG as Monotherapy
Indication | Recommended OPDIVO QVANTIG Dosage | Duration of Therapy
Advanced renal cell carcinoma† | 600 mg nivolumab and 10,000 units hyaluronidase every 2 weeks; or; 1,200 mg nivolumab and 20,000 units hyaluronidase every 4 weeks | Until disease progression or unacceptable toxicity
Metastatic non-small cell lung cancer | 600 mg nivolumab and 10,000 units hyaluronidase every 2 weeks; or; 1,200 mg nivolumab and 20,000 units hyaluronidase every 4 weeks | Until disease progression or unacceptable toxicity
Squamous cell carcinoma of the head and neck | 600 mg nivolumab and 10,000 units hyaluronidase every 2 weeks; or; 1,200 mg nivolumab and 20,000 units hyaluronidase every 4 weeks | Until disease progression or unacceptable toxicity
Locally advanced or metastatic urothelial carcinoma | 600 mg nivolumab and 10,000 units hyaluronidase every 2 weeks; or; 1,200 mg nivolumab and 20,000 units hyaluronidase every 4 weeks | Until disease progression or unacceptable toxicity
Hepatocellular carcinoma previously treated with sorafenib† | 600 mg nivolumab and 10,000 units hyaluronidase every 2 weeks; or; 1,200 mg nivolumab and 20,000 units hyaluronidase every 4 weeks | Until disease progression or unacceptable toxicity
Esophageal squamous cell carcinoma | 600 mg nivolumab and 10,000 units hyaluronidase every 2 weeks; or; 1,200 mg nivolumab and 20,000 units hyaluronidase every 4 weeks | Until disease progression or unacceptable toxicity
Unresectable or metastatic melanoma† | Adult patients and pediatric patients age 12 years and older and weighing 40 kg or greater:; 600 mg nivolumab and 10,000 units hyaluronidase every 2 weeks; or; 1,200 mg nivolumab and 20,000 units hyaluronidase every 4 weeks | Until disease progression or unacceptable toxicity
Unresectable or metastatic melanoma† | Pediatric patients age 12 years and older and weighing 30 kg or greater but less than 40 kg:; 300 mg nivolumab and 5,000 units hyaluronidase every 2 weeks; or; 600 mg nivolumab and 10,000 units hyaluronidase every 4 weeks | Until disease progression or unacceptable toxicity
Adjuvant treatment of melanoma | Adult patients and pediatric patients age 12 years and older and weighing 40 kg or greater:; 600 mg nivolumab and 10,000 units hyaluronidase every 2 weeks; or; 1,200 mg nivolumab and 20,000 units hyaluronidase every 4 weeks | Until disease recurrence or unacceptable toxicity for up to 1 year
Adjuvant treatment of melanoma | Pediatric patients age 12 years and older and weighing 30 kg or greater but less than 40 kg:; 300 mg nivolumab and 5,000 units hyaluronidase every 2 weeks; or; 600 mg nivolumab and 10,000 units hyaluronidase every 4 weeks | Until disease recurrence or unacceptable toxicity for up to 1 year
Unresectable or metastatic microsatellite instability-high (MSI-H) or mismatch repair deficient (dMMR) colorectal cancer† | Adult patients and pediatric patients age 12 years and older and weighing 40 kg or greater:; 600 mg nivolumab and 10,000 units hyaluronidase every 2 weeks; or; 1,200 mg nivolumab and 20,000 units hyaluronidase every 4 weeks | Until disease progression or unacceptable toxicity, or up to 2 years
Unresectable or metastatic microsatellite instability-high (MSI-H) or mismatch repair deficient (dMMR) colorectal cancer† | Pediatric patients age 12 years and older and weighing 30 kg or greater but less than 40 kg:; 300 mg nivolumab and 5,000 units hyaluronidase every 2 weeks; or; 600 mg nivolumab and 10,000 units hyaluronidase every 4 weeks | Until disease progression or unacceptable toxicity, or up to 2 years
Microsatellite instability-high (MSI-H) or mismatch repair deficient (dMMR) metastatic colorectal cancer that has progressed following prior treatment for metastatic disease† | Adult patients and pediatric patients age 12 years and older and weighing 40 kg or greater:; 600 mg nivolumab and 10,000 units hyaluronidase every 2 weeks; or; 1,200 mg nivolumab and 20,000 units hyaluronidase every 4 weeks | Until disease progression or unacceptable toxicity
Microsatellite instability-high (MSI-H) or mismatch repair deficient (dMMR) metastatic colorectal cancer that has progressed following prior treatment for metastatic disease† | Pediatric patients age 12 years and older and weighing 30 kg or greater but less than 40 kg:; 300 mg nivolumab and 5,000 units hyaluronidase every 2 weeks; or; 600 mg nivolumab and 10,000 units hyaluronidase every 4 weeks | Until disease progression or unacceptable toxicity
First-line unresectable or metastatic hepatocellular carcinoma† | 600 mg nivolumab and 10,000 units hyaluronidase every 2 weeks; or; 1,200 mg nivolumab and 20,000 units hyaluronidase every 4 weeks | Until disease progression or unacceptable toxicity, or up to 2 years
Adjuvant treatment of urothelial carcinoma | 600 mg nivolumab and 10,000 units hyaluronidase every 2 weeks; or; 1,200 mg nivolumab and 20,000 units hyaluronidase every 4 weeks | Until disease recurrence or unacceptable toxicity for up to 1 year
Adjuvant treatment of resected esophageal or gastroesophageal junction cancer | 600 mg nivolumab and 10,000 units hyaluronidase every 2 weeks; or; 1,200 mg nivolumab and 20,000 units hyaluronidase every 4 weeks | Until disease recurrence or unacceptable toxicity for up to 1 year
† Dosing recommendations for monotherapy or monotherapy following intravenous nivolumab and ipilimumab combination therapy.

The recommended dosages of OPDIVO QVANTIG in combination with other therapeutic agents are presented in Table 2. Refer to the respective Prescribing Information for each therapeutic agent administered in combination with OPDIVO QVANTIG for the recommended dosage information, as appropriate.

Table 2: Recommended Dosages for OPDIVO QVANTIG in Combination with Other Therapeutic Agents
Indication | Recommended OPDIVO QVANTIG Dosage | Duration of Therapy
Advanced renal cell carcinoma | 600 mg nivolumab and 10,000 units hyaluronidase every 2 weeks; or; 1,200 mg nivolumab and 20,000 units hyaluronidase every 4 weeks; Administer OPDIVO QVANTIG in combination with cabozantinib 40 mg orally once daily without food | OPDIVO QVANTIG: Until disease progression, unacceptable toxicity, or up to 2 years; Cabozantinib: Until disease progression or unacceptable toxicity
Neoadjuvant treatment of resectable non-small cell lung cancer | 900 mg nivolumab and 15,000 units hyaluronidase with platinum-doublet chemotherapy on the same day every 3 weeks | In combination with platinum-doublet chemotherapy for 3 cycles
Neoadjuvant and adjuvant treatment of resectable non-small cell lung cancer | Neoadjuvant: 900 mg nivolumab and 15,000 units hyaluronidase with platinum-doublet chemotherapy on the same day every 3 weeks | Neoadjuvant: in combination with platinum-doublet chemotherapy until disease progression or unacceptable toxicity, for up to 4 cycles
Neoadjuvant and adjuvant treatment of resectable non-small cell lung cancer | Adjuvant: 1,200 mg nivolumab and 20,000 units hyaluronidase every 4 weeks | Adjuvant: following neoadjuvant therapy and surgery, administer as a single agent until disease progression, recurrence, or unacceptable toxicity, for up to 13 cycles (up to 1 year)
First-line unresectable or metastatic urothelial carcinoma | 900 mg nivolumab and 15,000 units hyaluronidase every 3 weeks Administer OPDIVO QVANTIG in combination with cisplatin and gemcitabine on the same day every 3 weeks | In combination with cisplatin and gemcitabine for up to 6 cycles
First-line unresectable or metastatic urothelial carcinoma | 600 mg nivolumab and 10,000 units hyaluronidase every 2 weeks; or; 1,200 mg nivolumab and 20,000 units hyaluronidase every 4 weeks | After completing up to 6 cycles of combination therapy, administer as single agent until disease progression, unacceptable toxicity, or up to 2 years from first dose
Esophageal squamous cell carcinoma | 600 mg nivolumab and 10,000 units hyaluronidase every 2 weeks; or; 1,200 mg nivolumab and 20,000 units hyaluronidase every 4 weeks; Administer OPDIVO QVANTIG in combination with fluoropyrimidine- and platinum-containing chemotherapy | Until disease progression, unacceptable toxicity, or up to 2 years
Esophageal squamous cell carcinoma | 600 mg nivolumab and 10,000 units hyaluronidase every 2 weeks; or; 1,200 mg nivolumab and 20,000 units hyaluronidase every 4 weeks; Administer OPDIVO QVANTIG in combination with fluoropyrimidine- and platinum-containing chemotherapy | Chemotherapy: Until disease progression or unacceptable toxicity
Gastric cancer, gastroesophageal junction cancer, and esophageal adenocarcinoma | 600 mg nivolumab and 10,000 units hyaluronidase with fluoropyrimidine- and platinum-containing chemotherapy every 2 weeks; or; 900 mg nivolumab and 15,000 units hyaluronidase with fluoropyrimidine- and platinum-containing chemotherapy every 3 weeks | OPDIVO QVANTIG: Until disease progression, unacceptable toxicity, or up to 2 years; Chemotherapy: Until disease progression or unacceptable toxicity

2.4 Dosage Modifications

No dose reduction for OPDIVO QVANTIG is recommended. In general, withhold OPDIVO QVANTIG for severe (Grade 3) immune-mediated adverse reactions. Permanently discontinue OPDIVO QVANTIG for life-threatening (Grade 4) immune-mediated adverse reactions, recurrent severe (Grade 3) immune-mediated reactions that require systemic immunosuppressive treatment, or an inability to reduce corticosteroid dose to 10 mg or less of prednisone or equivalent per day within 12 weeks of initiating steroids.

Dosage modifications for OPDIVO QVANTIG or OPDIVO QVANTIG in combination with other anti-cancer agents for adverse reactions that require management different from these general guidelines are summarized in Table 3 and Table 4.

Table 3: Recommended Dosage Modifications for Adverse Reactions
Adverse Reaction | Severity | Dosage Modification
Immune-Mediated Adverse Reactions [see Warnings and Precautions (5.1)]
Pneumonitis | Grade 2 | Withholda
Pneumonitis | Grade 3 or 4 | Permanently discontinue
Colitis; For colitis in patients treated with combination therapy with ipilimumab, see Table 4. | Grade 2 or 3 | Withholda
Colitis; For colitis in patients treated with combination therapy with ipilimumab, see Table 4. | Grade 4 | Permanently discontinue
Hepatitis with no tumor involvement of the liver; For liver enzyme elevations in patients treated with combination therapy with cabozantinib, see Table 4. | AST/ALT increases to >3 and ≤8 times ULN; or; Total bilirubin increases to >1.5 and ≤3 times ULN. | Withholda
Hepatitis with no tumor involvement of the liver; For liver enzyme elevations in patients treated with combination therapy with cabozantinib, see Table 4. | AST or ALT increases to >8 times ULN; or; Total bilirubin increases to >3 times ULN. | Permanently discontinue
Hepatitis with tumor involvement of the liverb | Baseline AST/ALT is >1 and ≤3 times ULN and increases to >5 and ≤10 times ULN; or; Baseline AST/ALT is >3 and ≤5 times ULN and increases to >8 and ≤10 times ULN. | Withholda
Hepatitis with tumor involvement of the liverb | AST/ALT increases to >10 times ULN; or; Total bilirubin increases to >3 times ULN. | Permanently discontinue
Endocrinopathiesc | Grade 3 or 4 | Withhold until clinically stable or permanently discontinue depending on severity
Nephritis with Renal Dysfunction | Grade 2 or 3 increased blood creatinine | Withholda
Nephritis with Renal Dysfunction | Grade 4 increased blood creatinine | Permanently discontinue
Exfoliative Dermatologic Conditions | Suspected SJS, TEN, or DRESS | Withhold
Exfoliative Dermatologic Conditions | Confirmed SJS, TEN, or DRESS | Permanently discontinue
Myocarditis | Grades 2, 3, or 4 | Permanently discontinue
Neurological Toxicities | Grade 2 | Withholda
Neurological Toxicities | Grade 3 or 4 | Permanently discontinue
a Resume in patients with complete or partial resolution (Grade 0 to 1) after corticosteroid taper. Permanently discontinue if no complete or partial resolution within 12 weeks of last dose or inability to reduce prednisone to 10 mg per day (or equivalent) or less within 12 weeks of initiating steroids.
b If AST and ALT are less than or equal to ULN at baseline, withhold or permanently discontinue OPDIVO QVANTIG based on recommendations for hepatitis with no liver involvement.
c Depending on clinical severity, consider withholding for Grade 2 endocrinopathy until symptom improvement with hormone replacement. Resume once acute symptoms have resolved.
ALT = alanine aminotransferase, AST = aspartate aminotransferase, DRESS = Drug Rash with Eosinophilia and Systemic Symptoms, SJS = Stevens-Johnson Syndrome, TEN = toxic epidermal necrolysis, ULN = upper limit of normal

Table 4: Recommended Dosage Modifications for Adverse Reactions in Patients Treated with Combination Therapy
Treatment | Adverse Reaction | Severity | Dosage Modification
OPDIVO QVANTIG in combination with cabozantinib | Liver enzyme elevations | ALT or AST >3 times ULN but ≤10 times ULN with concurrent total bilirubin <2 times ULN | Withholda both OPDIVO QVANTIG and cabozantinib until adverse reactions recoverb to Grades 0-1
OPDIVO QVANTIG in combination with cabozantinib | Liver enzyme elevations | ALT or AST >10 times ULN or >3 times ULN with concurrent total bilirubin ≥2 times ULN | Permanently discontinuea both OPDIVO QVANTIG and cabozantinib
a Consider corticosteroid therapy for hepatic adverse reactions if OPDIVO QVANTIG is withheld or discontinued when administered in combination with cabozantinib.
b After recovery, rechallenge with one or both of OPDIVO QVANTIG and cabozantinib may be considered. If rechallenging with cabozantinib with or without OPDIVO QVANTIG, refer to cabozantinib Prescribing Information.

2.5 Preparation and Administration

To prevent medication errors, check the vial labels to ensure that the drug being prepared and administered is OPDIVO QVANTIG for subcutaneous use and NOT intravenous nivolumab. Do NOT administer OPDIVO QVANTIG intravenously. OPDIVO QVANTIG should be administered by a healthcare professional.

Each OPDIVO QVANTIG vial is for one-time use only. It is a ready-to-use solution for injection. It should not be diluted.

Visually inspect for particulate matter and discoloration prior to administration. OPDIVO QVANTIG is a clear to opalescent, colorless to yellow solution. Discard if the solution is discolored or contains extraneous particulate matter other than a few translucent-to-white particles. Do not shake.

Preparation

No incompatibilities were observed between OPDIVO QVANTIG and polypropylene and polycarbonate syringes, or between OPDIVO QVANTIG and polyethylene, polyurethane, polyvinyl chloride, and fluorinated ethylene propylene subcutaneous administration sets.

A syringe and a transfer needle are needed to withdraw OPDIVO QVANTIG solution from the vial. OPDIVO QVANTIG may be injected subcutaneously using a 23G to 25G (3/8 to 5/8 inch) hypodermic injection needle or subcutaneous administration set (eg., winged/butterfly).

Calculate the appropriate number of vials of OPDIVO QVANTIG (300 mg/5,000 units and/or 600 mg/10,000 units) needed based on the prescribed dose.

Allow vial(s) to reach room temperature 20°C to 25°C (68°F to 77°F) before withdrawing dose.

- 300 mg nivolumab and 5,000 units hyaluronidase
  ∘ Withdraw 2.5 mL from the 300 mg/5,000 units vial of OPDIVO QVANTIG into the syringe.
- 600 mg nivolumab and 10,000 units hyaluronidase
  ∘ Withdraw 5 mL from the 600 mg/10,000 units vial of OPDIVO QVANTIG into the syringe.
- 900 mg nivolumab and 15,000 units hyaluronidase
  ∘ Withdraw 5 mL from the 600 mg/10,000 units vial and 2.5 mL from the 300 mg/5,000 units vial of OPDIVO QVANTIG into a single syringe for a total volume of 7.5 mL.
- 1,200 mg nivolumab and 20,000 units hyaluronidase
  ∘ Withdraw 5 mL from each vial of 600 mg/10,000 units OPDIVO QVANTIG into a single syringe for a total volume of 10 mL.

Select the appropriate syringe label provided in the carton that matches the prescribed dose and apply to the prepared syringe.

Discard partially used or empty vials of OPDIVO QVANTIG.

If the dose is not to be used immediately, attach a tip cap to the syringe prior to storage. To avoid clogging of the hypodermic injection needle, attach a 23G to 25G (3/8 to 5/8 inch) hypodermic injection needle to the syringe immediately prior to administration.

Storage in Syringe

Once withdrawn into the syringe, OPDIVO QVANTIG should be used immediately. If not used immediately, store the syringe:

- In the refrigerator at 2°C to 8°C (36°F to 46°F), protected from light for up to 72 hours; do not freeze, or
- At room temperature 20°C to 25°C (68°F to 77°F) for up to 8 hours. Storage at room temperature for this duration does not require protection from light.
- Discard if storage time exceeds these limits.
- If stored in the refrigerator, allow the solution to come to room temperature before administration.

Administration

- Administer the full contents of the syringe into the subcutaneous tissue of 1 of the 4 quadrants of the abdomen, or thigh over a period of 3 to 5 minutes.
- Alternate injection sites across the 4 quadrants of the abdomen or thighs for successive injections. Do not inject into areas where the skin is tender, red, or bruised, or areas where there are scars or moles. If the administration of OPDIVO QVANTIG is interrupted, continue administering at the same site, or at an alternate site.
- During treatment with OPDIVO QVANTIG, do not administer other subcutaneous medications at the same site used for OPDIVO QVANTIG.

3 DOSAGE FORMS AND STRENGTHS

Injection: 300 mg nivolumab and 5,000 units hyaluronidase per 2.5 mL (120 mg/2,000 units per mL), as a clear to opalescent, colorless to yellow solution in a single-dose vial.

Injection: 600 mg nivolumab and 10,000 units hyaluronidase per 5 mL (120 mg/2,000 units per mL), as a clear to opalescent, colorless to yellow solution in a single-dose vial.

4 CONTRAINDICATIONS

None.

5 WARNINGS AND PRECAUTIONS

5.1 Severe and Fatal Immune-Mediated Adverse Reactions

OPDIVO QVANTIG is a combination of a monoclonal antibody that belongs to a class of drugs that bind to either the programmed death-receptor 1 (PD-1) or the PD-ligand 1 (PD-L1), blocking the PD-1/PD-L1 pathway, thereby removing inhibition of the immune response, potentially breaking peripheral tolerance, and inducing immune-mediated adverse reactions, and an endoglycosidase used to increase the dispersion and absorption of co-administered drugs when administered subcutaneously. Important immune-mediated adverse reactions listed under Warnings and Precautions may not include all possible severe and fatal immune-mediated reactions.

Immune-mediated adverse reactions, which may be severe or fatal, can occur in any organ system or tissue. Immune-mediated adverse reactions can occur at any time after starting treatment with a PD-1/PD-L1 blocking antibody. While immune-mediated adverse reactions usually manifest during treatment with PD‑1/PD-L1 blocking antibodies, immune-mediated adverse reactions can also manifest after discontinuation of PD-1/PD-L1 blocking antibodies.

Early identification and management of immune-mediated adverse reactions are essential to ensure safe use of PD-1/PD-L1 blocking antibodies. Monitor patients closely for symptoms and signs that may be clinical manifestations of underlying immune-mediated adverse reactions. Evaluate liver enzymes, creatinine, and thyroid function at baseline and periodically during treatment. In cases of suspected immune-mediated adverse reactions, initiate appropriate workup to exclude alternative etiologies, including infection. Institute medical management promptly, including specialty consultation as appropriate.

Withhold or permanently discontinue OPDIVO QVANTIG depending on severity [see Dosage and Administration (2.4)]. In general, if OPDIVO QVANTIG requires interruption or discontinuation, administer systemic corticosteroid therapy (1 to 2 mg/kg/day prednisone or equivalent) until improvement to Grade 1 or less. Upon improvement to Grade 1 or less, initiate corticosteroid taper and continue to taper over at least 1 month. Consider administration of other systemic immunosuppressants in patients whose immune-mediated adverse reactions are not controlled with corticosteroid therapy.

Toxicity management guidelines for adverse reactions that do not necessarily require systemic steroids (e.g., endocrinopathies and dermatologic reactions) are discussed below.

Immune-Mediated Pneumonitis

OPDIVO QVANTIG can cause immune-mediated pneumonitis, which is defined as requiring use of steroids and no clear alternate etiology. In patients treated with other PD-1/PD-L1 blocking antibodies, the incidence of pneumonitis is higher in patients who have received prior thoracic radiation.

Immune-mediated pneumonitis occurred in 2.8% (7/247) of patients receiving OPDIVO QVANTIG, including Grade 3 (0.8%) and Grade 2 (2.0%) adverse reactions. Pneumonitis led to permanent discontinuation of OPDIVO QVANTIG in 1.6% and withholding of OPDIVO QVANTIG in 1.6% of patients.

Systemic corticosteroids were required in 100% (7/7) of patients with pneumonitis. Pneumonitis resolved in 27% of the 7 patients. Of the 4 patients in whom OPDIVO QVANTIG was withheld for pneumonitis, 2 reinitiated OPDIVO QVANTIG after symptom improvement; of these, 1 (50%) had recurrence of pneumonitis.

Immune-Mediated Colitis

OPDIVO QVANTIG can cause immune-mediated colitis, defined as requiring use of corticosteroids and no clear alternate etiology. A common symptom included in the definition of colitis was diarrhea. Cytomegalovirus (CMV) infection/reactivation has been reported in patients with corticosteroid-refractory immune-mediated colitis. In cases of corticosteroid-refractory colitis, consider repeating infectious workup to exclude alternative etiologies.

Immune-mediated colitis occurred in 2.8% (7/247) of patients receiving OPDIVO QVANTIG, including Grade 3 (0.4%) and Grade 2 (2.4%) adverse reactions. Colitis led to withholding of OPDIVO QVANTIG in 2.0% of patients.

Systemic corticosteroids were required in 100% (7/7) of patients with colitis. Colitis resolved in 71% of the 7 patients. Of the 5 patients in whom OPDIVO QVANTIG was withheld for colitis, 3 reinitiated OPDIVO QVANTIG after symptom improvement; of these, 2 (67%) had recurrence of colitis.

Immune-Mediated Hepatitis and Hepatotoxicity

OPDIVO QVANTIG can cause immune-mediated hepatitis, defined as requiring the use of corticosteroids and no clear alternate etiology.

Immune-mediated hepatitis occurred in 2.4% (6/247) of patients receiving OPDIVO QVANTIG, including Grade 3 (1.6%), and Grade 2 (0.8%) adverse reactions. Hepatitis led to permanent discontinuation of OPDIVO QVANTIG in 0.8% and withholding of OPDIVO QVANTIG in 1.6% of patients.

Systemic corticosteroids were required in 100% (6/6) of patients with hepatitis. Hepatitis resolved in 67% of the 6 patients. Of the 2 patients in whom OPDIVO QVANTIG was withheld for hepatitis, 2 reinitiated OPDIVO QVANTIG after symptom improvement; of these, 1 (50%) had recurrence of hepatitis.

Intravenous Nivolumab with Cabozantinib

Nivolumab in combination with cabozantinib can cause hepatic toxicity with higher frequencies of Grade 3 and 4 ALT and AST elevations compared to nivolumab alone. Monitor liver enzymes before initiation of and periodically throughout treatment. Consider more frequent monitoring of liver enzymes as compared to when the drugs are administered as single agents. For elevated liver enzymes, interrupt nivolumab and cabozantinib and consider administering corticosteroids [see Dosage and Administration (2.4)].

With the combination of intravenous nivolumab and cabozantinib, Grades 3 and 4 increased ALT or AST were seen in 11% (35/320) of patients. ALT or AST >3 times ULN (Grade ≥2) was reported in 83 patients, of whom 23 (28%) received systemic corticosteroids; ALT or AST resolved to Grades 0-1 in 74 (89%). Among the 44 patients with Grade ≥2 increased ALT or AST who were rechallenged with either intravenous nivolumab (n=11) or cabozantinib (n=9) administered as a single agent or with both (n=24), recurrence of Grade ≥2 increased ALT or AST was observed in 2 patients receiving intravenous nivolumab, 2 patients receiving cabozantinib, and 7 patients receiving both intravenous nivolumab and cabozantinib.

Immune-Mediated Endocrinopathies

Adrenal Insufficiency

OPDIVO QVANTIG can cause primary or secondary adrenal insufficiency. For Grade 2 or higher adrenal insufficiency, initiate symptomatic treatment, including hormone replacement as clinically indicated. Withhold OPDIVO QVANTIG depending on severity [see Dosage and Administration (2.4)].

Adrenal insufficiency occurred in 2% (5/247) of patients receiving OPDIVO QVANTIG, including Grade 3 (0.8%) and Grade 2 (1.2%) adverse reactions. Adrenal insufficiency led to permanent discontinuation of OPDIVO QVANTIG in 0.4% of patients and withholding of OPDIVO QVANTIG in 0.4% of patients.

Systemic corticosteroids were required in 100% (5/5) of patients with adrenal insufficiency. Adrenal insufficiency resolved in 20% of the 5 patients.

Intravenous Nivolumab with Cabozantinib

Adrenal insufficiency occurred in 4.7% (15/320) of patients with RCC who received intravenous nivolumab with cabozantinib, including Grade 3 (2.2%) and Grade 2 (1.9%) adverse reactions. Adrenal insufficiency led to permanent discontinuation of intravenous nivolumab and cabozantinib in 0.9% and withholding of intravenous nivolumab and cabozantinib in 2.8% of patients with RCC.

Approximately 80% (12/15) of patients with adrenal insufficiency received hormone replacement therapy, including systemic corticosteroids. Adrenal insufficiency resolved in 27% (n=4) of the 15 patients. Of the 9 patients in whom intravenous nivolumab with cabozantinib was withheld for adrenal insufficiency, 6 reinstated treatment after symptom improvement; of these, all (n=6) received hormone replacement therapy and 2 had recurrence of adrenal insufficiency.

Hypophysitis

OPDIVO QVANTIG can cause immune-mediated hypophysitis. Hypophysitis can present with acute symptoms associated with mass effect such as headache, photophobia, or visual field defects. Hypophysitis can cause hypopituitarism. Initiate hormone replacement as clinically indicated. Withhold or permanently discontinue OPDIVO QVANTIG depending on severity [see Dosage and Administration (2.4)].

Intravenous Nivolumab

Hypophysitis occurred in 0.6% (12/1994) of patients treated with single agent intravenous nivolumab, including Grade 3 (0.2%) and Grade 2 (0.3%). Hypophysitis led to permanent discontinuation of intravenous nivolumab in <0.1% and withholding of intravenous nivolumab in 0.2% of patients. Approximately 67% (8/12) of patients with hypophysitis received hormone replacement therapy, including systemic corticosteroids. Hypophysitis resolved in 42% of the 12 patients. Of the 3 patients in whom intravenous nivolumab was withheld for hypophysitis, 2 reinitiated intravenous nivolumab after symptom improvement; of these, none had recurrence of hypophysitis.

Thyroid Disorders

OPDIVO QVANTIG can cause immune-mediated thyroid disorders. Thyroiditis can present with or without endocrinopathy. Hypothyroidism can follow hyperthyroidism. Initiate hormone replacement or medical management as clinically indicated. Withhold or permanently discontinue OPDIVO QVANTIG depending on severity [see Dosage and Administration (2.4)].

Thyroiditis

Thyroiditis occurred in 0.4% (1/247) of patients receiving OPDIVO QVANTIG, including a Grade 1 (0.4%) adverse reaction.

Systemic corticosteroids were not required in the patient with thyroiditis. Thyroiditis did not resolve in this patient.

Hyperthyroidism

Hyperthyroidism occurred in 0.8% (2/247) of patients receiving OPDIVO QVANTIG, including Grade 2 (0.4%) adverse reactions.

Systemic corticosteroids were not required in patients with hyperthyroidism. Hyperthyroidism resolved in 50% of the 2 patients.

Hypothyroidism

Hypothyroidism occurred in 9% (23/247) of patients receiving OPDIVO QVANTIG, including Grade 2 (5.7%) adverse reactions. Hypothyroidism led to withholding of OPDIVO QVANTIG in 0.8% of patients.

Systemic corticosteroids were not required in patients with hypothyroidism. Hypothyroidism resolved in 4.3% of the 23 patients. Of the 1 patient in whom OPDIVO QVANTIG was withheld for hypothyroidism, OPDIVO QVANTIG was not reinitiated after symptom improvement.

Type 1 Diabetes Mellitus, which can present with Diabetic Ketoacidosis

Monitor patients for hyperglycemia or other signs and symptoms of diabetes. Initiate treatment with insulin as clinically indicated. Withhold OPDIVO QVANTIG depending on severity [see Dosage and Administration (2.4)].

Grade 3 diabetes occurred in 0.4% (1/247) of patients receiving OPDIVO QVANTIG.

No patients with diabetes required systemic corticosteroids. Diabetes did not resolve in this patient.

Immune-Mediated Nephritis with Renal Dysfunction

OPDIVO QVANTIG can cause immune-mediated nephritis, which is defined as requiring use of steroids and no clear alternate etiology.

Grade 2 immune-mediated nephritis and renal dysfunction occurred in 1.2% (3/247) of patients receiving OPDIVO QVANTIG. Immune-mediated nephritis and renal dysfunction led to withholding of OPDIVO QVANTIG in 1.2% of patients.

Systemic corticosteroids were required in 100% (3/3) of patients with nephritis and renal dysfunction. Nephritis and renal dysfunction resolved in 100% of the 3 patients. Of the 3 patients in whom OPDIVO QVANTIG was withheld for nephritis or renal dysfunction, 1 reinitiated OPDIVO QVANTIG after symptom improvement without recurrence of nephritis or renal dysfunction.

Immune-Mediated Dermatologic Adverse Reactions

OPDIVO QVANTIG can cause immune-mediated rash or dermatitis, defined as requiring the use of steroids and no clear alternate etiology. Exfoliative dermatitis, including Stevens-Johnson Syndrome, toxic epidermal necrolysis (TEN), and DRESS (Drug Rash with Eosinophilia and Systemic Symptoms), has occurred with PD-1/PD-L1 blocking antibodies. Topical emollients and/or topical corticosteroids may be adequate to treat mild to moderate non-exfoliative rashes. Withhold or permanently discontinue OPDIVO QVANTIG depending on severity [see Dosage and Administration (2.4)].

Immune-mediated rash occurred in 7% (17/247) of patients, including Grade 3 (0.8%) and Grade 2 (2.8%) adverse reactions. Immune-mediated rash led to withholding of OPDIVO QVANTIG in 1.2% of patients.

Systemic corticosteroids were required in 47% (8/17) of patients with immune-mediated rash. Rash resolved in 77% of the 17 patients. Of the 3 patients in whom OPDIVO QVANTIG was withheld for immune-mediated rash, all reinitiated OPDIVO QVANTIG after symptom improvement; of these, all (100%) had recurrence of immune-mediated rash.

Other Immune-Mediated Adverse Reactions

The following clinically significant immune-mediated adverse reactions occurred at an incidence of <1% (unless otherwise noted) in patients who received OPDIVO QVANTIG or intravenous nivolumab as a single agent or in combination with chemotherapy or immunotherapy, or were reported with the use of other PD-1/PD-L1 blocking antibodies. Severe or fatal cases have been reported for some of these adverse reactions.

Cardiac/Vascular: Myocarditis, pericarditis, vasculitis

Nervous System: Meningitis, encephalitis, myelitis and demyelination, myasthenic syndrome/myasthenia gravis (including exacerbation), Guillain-Barre syndrome, nerve paresis, autoimmune neuropathy

Ocular: Uveitis, iritis, and other ocular inflammatory toxicities can occur. Some cases can be associated with retinal detachment. Various grades of visual impairment, including blindness, can occur. If uveitis occurs in combination with other immune-mediated adverse reactions, consider a Vogt-Koyanagi-Harada-like syndrome, as this may require treatment with systemic steroids to reduce the risk of permanent vision loss

Gastrointestinal: Pancreatitis to include increases in serum amylase and lipase levels, gastritis, duodenitis

Musculoskeletal and Connective Tissue: Myositis/polymyositis, rhabdomyolysis, and associated sequelae including renal failure, arthritis, polymyalgia rheumatic

Endocrine: Hypoparathyroidism

Other (Hematologic/Immune): Hemolytic anemia, aplastic anemia, hemophagocytic lymphohistiocytosis, systemic inflammatory response syndrome, histiocytic necrotizing lymphadenitis (Kikuchi lymphadenitis), sarcoidosis, immune thrombocytopenic purpura, solid organ transplant rejection, other transplant (including corneal graft) rejection.

5.2 Complications of Allogeneic Hematopoietic Stem Cell Transplantation

Fatal and other serious complications can occur in patients who receive allogeneic hematopoietic stem cell transplantation (HSCT) before or after being treated with a PD-1 receptor blocking antibody. Transplant-related complications include hyperacute graft-versus-host-disease (GVHD), acute GVHD, chronic GVHD, hepatic veno-occlusive disease (VOD) after reduced intensity conditioning, and steroid-requiring febrile syndrome (without an identified infectious cause) [see Adverse Reactions (6.1)]. These complications may occur despite intervening therapy between PD-1 blockade and allogeneic HSCT.

Follow patients closely for evidence of transplant-related complications and intervene promptly. Consider the benefit versus risks of treatment with a PD-1 receptor blocking antibody prior to or after an allogeneic HSCT.

5.3 Embryo-Fetal Toxicity

Based on its mechanism of action and data from animal studies, OPDIVO QVANTIG can cause fetal harm when administered to a pregnant woman. In animal reproduction studies, administration of nivolumab to cynomolgus monkeys from the onset of organogenesis through delivery resulted in increased abortion and premature infant death. Advise pregnant women of the potential risk to a fetus. Advise females of reproductive potential to use effective contraception during treatment with OPDIVO QVANTIG and for 5 months after the last dose [see Use in Specific Populations (8.1, 8.3)].

5.4 Increased Mortality in Patients with Multiple Myeloma when Nivolumab Is Added to a Thalidomide Analogue and Dexamethasone

In randomized clinical trials in patients with multiple myeloma, the addition of a PD-1 blocking antibody, including intravenous nivolumab, to a thalidomide analogue plus dexamethasone, a use for which no PD-1 or PD-L1 blocking antibody is indicated, resulted in increased mortality. Treatment of patients with multiple myeloma with a PD-1 or PD-L1 blocking antibody in combination with a thalidomide analogue plus dexamethasone is not recommended outside of controlled clinical trials.

6 ADVERSE REACTIONS

The following clinically significant adverse reactions are described elsewhere in the labeling.

- Severe and Fatal Immune-Mediated Adverse Reactions [see Warnings and Precautions (5.1)]
- Complications of Allogeneic HSCT [see Warnings and Precautions (5.2)]

6.1 Clinical Trials Experience

Because clinical trials are conducted under widely varying conditions, adverse reaction rates observed in the clinical trials of a drug cannot be directly compared to rates in the clinical trials of another drug and may not reflect the rates observed in practice.

The data in WARNINGS AND PRECAUTIONS reflect exposure to OPDIVO QVANTIG as a single agent in 247 patients enrolled in CHECKMATE-67T, with additional data from intravenous nivolumab single-agent (1994 patients), and from intravenous nivolumab in combination with cabozantinib (320 patients) for select adverse reactions.

Advanced Renal Cell Carcinoma

CHECKMATE-67T was a multicenter, randomized, open-label study in adult patients with advanced or metastatic RCC. Patients received OPDIVO QVANTIG dose of 1,200 mg of nivolumab and 20,000 units of hyaluronidase subcutaneously every 4 weeks (n=247) or 3 mg/kg of nivolumab intravenously every 2 weeks (n=245). Among patients who received OPDIVO QVANTIG, 52% were exposed for 6 months or longer and 20% were exposed for greater than 1 year.

Serious adverse reactions occurred in 28% of patients who received OPDIVO QVANTIG. Serious adverse reactions in >1% of patients included pleural effusion (1.6%), pneumonitis (1.6%), hyperglycemia (1.2%), hyperkalemia (1.2%), hemorrhage (1.2%) and diarrhea (1.2%). Fatal adverse reactions occurred in 3 patients (1.2%) who received OPDIVO QVANTIG and included myocarditis, myositis, and colitis complications.

Permanent discontinuation of OPDIVO QVANTIG due to an adverse reaction occurred in 10% of patients. The most common adverse reaction which resulted in permanent discontinuation was pneumonitis (2%).

Dosage interruptions of OPDIVO QVANTIG due to an adverse reaction occurred in 34% of patients. Adverse reactions which required dosage interruption in >2% of patients included COVID-19 (4.5%), increased blood creatinine (2.8%), anemia, diarrhea, and fatigue (2.4% each).

The most common adverse reactions (≥10%) were musculoskeletal pain, fatigue, pruritus, rash, hypothyroidism, diarrhea, cough, and abdominal pain.

Tables 5 and 6 summarize adverse reactions and laboratory abnormalities, respectively, in CHECKMATE-67T.

Table 5: Adverse Reactions* in ≥5% of Adult Patients with RCC Receiving OPDIVO QVANTIG in CHECKMATE-67T
Adverse Reaction | OPDIVO QVANTIG (n=247) |  | Intravenous Nivolumab (n=245)
Adverse Reaction | All Grades (%) | Grades 3-4 (%) | All Grades (%) | Grades 3-4 (%)
General
Fatiguea | 20 | 2.4 | 25 | 3.3
Injection site reactiona | 8 | 0 | 0 | 0
Edema | 5 | 0.4 | 11 | 0.8
Musculoskeletal and Connective Tissue
Musculoskeletal paina | 31 | 1.6 | 39 | 3.3
Skin and Subcutaneous Tissue
Pruritus | 16 | 0.4 | 21 | 0
Rasha | 15 | 1.2 | 13 | 1.2
Gastrointestinal
Diarrheaa | 11 | 0.4 | 14 | 0.4
Abdominal paina | 10 | 0 | 10 | 0.4
Nausea | 8 | 0 | 9 | 0
Constipation | 8 | 0 | 6 | 0
Vomiting | 6 | 0.4 | 4.9 | 0
Respiratory, Thoracic, and Mediastinal
Cough | 11 | 0 | 11 | 0
Endocrine
Hypothyroidisma | 12 | 0 | 17 | 0
Metabolism and Nutrition
Hyperglycemia | 9 | 2.4 | 13 | 2.0
Decreased appetite | 9 | 0 | 11 | 0.8
* Toxicity was graded per NCI CTCAE v5.
a Includes multiple related terms

Clinically important adverse reactions in <5% of patients who received OPDIVO QVANTIG include:

Cardiac: myocarditis

Respiratory, thoracic, and mediastinal: pneumonitis, dyspnea

Endocrine: adrenal insufficiency, hyperthyroidism, thyroiditis

Gastrointestinal: colitis, pancreatitis

Hepatobiliary: hepatitis

Nervous system: peripheral neuropathy

Skin and subcutaneous tissue: psoriasis, erythema

Musculoskeletal and connective tissue: arthritis

Blood and lymphatic system: eosinophilia

Eye disorders: uveitis

Immune system: hypersensitivity

Table 6: Laboratory Values Worsening from Baselinea (≥20%) in Patients with RCC Receiving OPDIVO QVANTIG in CHECKMATE-67T
Laboratory Abnormality | OPDIVO QVANTIG |  | Intravenous Nivolumab
Laboratory Abnormality | All Grades (%) | Grades 3-4 (%) | All Grades (%) | Grades 3-4 (%)
Hematology
Hemoglobin decreased | 46 | 7 | 48 | 9
Lymphocytes decreased | 36 | 6 | 45 | 9
Chemistry
Creatinine increased | 38 | 1.3 | 43 | 0.4
Sodium decreased | 34 | 2.6 | 40 | 2.5
Potassium increased | 34 | 3.0 | 45 | 2.9
Alkaline phosphatase increased | 32 | 2.1 | 33 | 2.0
Calcium increased | 29 | 2.1 | 31 | 4.1
Albumin decreased | 25 | 1.7 | 35 | 0.4
ALT increased | 21 | 1.3 | 26 | 4.1
a Each test incidence is based on the number of patients who had both baseline and at least one on-study laboratory measurement available: OPDIVO QVANTIG group (range: 232 to 235 patients) and intravenous nivolumab group (range: 240 to 244 patients).

Adverse Reactions in Patients Treated with Intravenous Nivolumab

The safety of OPDIVO QVANTIG for its approved indications [see Indications and Usage (1)] has been established in adequate and well-controlled clinical studies of intravenous nivolumab. Below is a description of adverse reactions in these adequate and well-controlled clinical studies.

First-line Renal Cell Carcinoma

CHECKMATE-214

The safety of intravenous nivolumab with ipilimumab was evaluated in CHECKMATE-214, a randomized open-label trial in 1082 patients with previously untreated advanced RCC; patients received intravenous nivolumab 3 mg/kg over 60 minutes with ipilimumab 1 mg/kg intravenously every 3 weeks for 4 doses followed by intravenous nivolumab as a single agent at a dose of 3 mg/kg by intravenous infusion every 2 weeks (n=547) or sunitinib 50 mg orally daily for the first 4 weeks of a 6-week cycle (n=535) [see Clinical Studies (14.1)]. The median duration of treatment was 7.9 months (range: 1 day to 21.4+ months) in intravenous nivolumab and ipilimumab-treated patients and 7.8 months (range: 1 day to 20.2+ months) in sunitinib-treated patients. In this trial, 57% of patients in the intravenous nivolumab and ipilimumab arm were exposed to treatment for >6 months and 38% of patients were exposed to treatment for >1 year.

Serious adverse reactions occurred in 59% of patients receiving intravenous nivolumab and ipilimumab. Study therapy was discontinued for adverse reactions in 31% of intravenous nivolumab and ipilimumab patients. Fifty-four percent (54%) of patients receiving intravenous nivolumab and ipilimumab had a dose interruption for an adverse reaction.

The most frequent serious adverse reactions reported in ≥2% of patients treated with intravenous nivolumab and ipilimumab were diarrhea, pyrexia, pneumonia, pneumonitis, hypophysitis, acute kidney injury, dyspnea, adrenal insufficiency, and colitis; in patients treated with sunitinib, they were pneumonia, pleural effusion, and dyspnea. The most common adverse reactions (reported in ≥20% of patients) were fatigue, rash, diarrhea, musculoskeletal pain, pruritus, nausea, cough, pyrexia, arthralgia, and decreased appetite. The most common laboratory abnormalities which have worsened compared to baseline in ≥30% of intravenous nivolumab and ipilimumab-treated patients include increased lipase, anemia, increased creatinine, increased ALT, increased AST, hyponatremia, increased amylase, and lymphopenia.

Tables 7 and 8 summarize adverse reactions and laboratory abnormalities, respectively, that occurred in >15% of intravenous nivolumab and ipilimumab‑treated patients in CHECKMATE-214.

Table 7: Adverse Reactions in >15% of Patients Receiving Intravenous Nivolumab and Ipilimumab - CHECKMATE-214
Adverse Reaction | Intravenous Nivolumab and Ipilimumab (n=547) |  | Sunitinib (n=535)
Adverse Reaction | Grades 1-4 (%) | Grades 3-4 (%) | Grades 1-4 (%) | Grades 3-4 (%)
Adverse Reaction | 99 | 65 | 99 | 76
General
Fatiguea | 58 | 8 | 69 | 13
Pyrexia | 25 | 0.7 | 17 | 0.6
Edemab | 16 | 0.5 | 17 | 0.6
Skin and Subcutaneous Tissue
Rashc | 39 | 3.7 | 25 | 1.1
Pruritus/generalized pruritus | 33 | 0.5 | 11 | 0
Gastrointestinal
Diarrhea | 38 | 4.6 | 58 | 6
Nausea | 30 | 2 | 43 | 1.5
Vomiting | 20 | 0.9 | 28 | 2.1
Abdominal pain | 19 | 1.6 | 24 | 1.9
Constipation | 17 | 0.4 | 18 | 0
Musculoskeletal and Connective Tissue
Musculoskeletal paind | 37 | 4 | 40 | 2.6
Arthralgia | 23 | 1.3 | 16 | 0
Respiratory, Thoracic and Mediastinal
Cough/productive cough | 28 | 0.2 | 25 | 0.4
Dyspnea/exertional dyspnea | 20 | 2.4 | 21 | 2.1
Metabolism and Nutrition
Decreased appetite | 21 | 1.8 | 29 | 0.9
Nervous System
Headache | 19 | 0.9 | 23 | 0.9
Endocrine
Hypothyroidism | 18 | 0.4 | 27 | 0.2
Toxicity was graded per NCI CTCAE v4.
a Includes asthenia.
b Includes peripheral edema, peripheral swelling.
c Includes dermatitis described as acneiform, bullous, and exfoliative, drug eruption, rash described as exfoliative, erythematous, follicular, generalized, macular, maculopapular, papular, pruritic, and pustular, fixed-drug eruption.
d Includes back pain, bone pain, musculoskeletal chest pain, musculoskeletal discomfort, myalgia, neck pain, pain in extremity, spinal pain.

Table 8: Laboratory Values Worsening from Baselinea Occurring in >15% of Patients on Intravenous Nivolumab and Ipilimumab - CHECKMATE-214
Laboratory Abnormality | Intravenous Nivolumab and Ipilimumab |  | Sunitinib
Laboratory Abnormality | Grades 1-4 (%) | Grades 3-4 (%) | Grades 1-4 (%) | Grades 3-4 (%)
Chemistry
Increased lipase | 48 | 20 | 51 | 20
Increased creatinine | 42 | 2.1 | 46 | 1.7
Increased ALT | 41 | 7 | 44 | 2.7
Increased AST | 40 | 4.8 | 60 | 2.1
Increased amylase | 39 | 12 | 33 | 7
Hyponatremia | 39 | 10 | 36 | 7
Increased alkaline phosphatase | 29 | 2 | 32 | 1
Hyperkalemia | 29 | 2.4 | 28 | 2.9
Hypocalcemia | 21 | 0.4 | 35 | 0.6
Hypomagnesemia | 16 | 0.4 | 26 | 1.6
Hematology
Anemia | 43 | 3 | 64 | 9
Lymphopenia | 36 | 5 | 63 | 14
a Each test incidence is based on the number of patients who had both baseline and at least one on-study laboratory measurement available: intravenous nivolumab and ipilimumab group (range: 490 to 538 patients) and sunitinib group (range: 485 to 523 patients).

In addition, among patients with TSH ≤ ULN at baseline, a lower proportion of patients experienced a treatment-emergent elevation of TSH > ULN in the intravenous nivolumab and ipilimumab group compared to the sunitinib group (31% and 61%, respectively).

CHECKMATE-9ER

The safety of intravenous nivolumab with cabozantinib was evaluated in CHECKMATE-9ER, a randomized, open-label study in patients with previously untreated advanced RCC. Patients received intravenous nivolumab 240 mg over 30 minutes every 2 weeks with cabozantinib 40 mg orally once daily (n=320) or sunitinib 50 mg daily, administered orally for 4 weeks on treatment followed by 2 weeks off (n=320) [see Clinical Studies (14.1)]. Cabozantinib could be interrupted or reduced to 20 mg daily or 20 mg every other day. The median duration of treatment was 14 months (range: 0.2 to 27 months) in intravenous nivolumab and cabozantinib-treated patients. In this trial, 82% of patients in the intravenous nivolumab and cabozantinib arm were exposed to treatment for >6 months and 60% of patients were exposed to treatment for >1 year.

Serious adverse reactions occurred in 48% of patients receiving intravenous nivolumab and cabozantinib. The most frequent (≥2%) serious adverse reactions were diarrhea, pneumonia, pneumonitis, pulmonary embolism, urinary tract infection, and hyponatremia. Fatal intestinal perforations occurred in 3 (0.9%) patients.

Adverse reactions leading to discontinuation of either intravenous nivolumab or cabozantinib occurred in 20% of patients: 7% intravenous nivolumab only, 8% cabozantinib only, and 6% both drugs due to same adverse reaction at the same time. Adverse reaction leading to dose interruption or reduction of either intravenous nivolumab or cabozantinib occurred in 83% of patients: 3% intravenous nivolumab only, 46% cabozantinib only, and 21% both drugs due to same adverse reaction at the same time, and 6% both drugs sequentially.

The most common adverse reactions reported in ≥20% of patients treated with intravenous nivolumab and cabozantinib were diarrhea, fatigue, hepatotoxicity, palmar-plantar erythrodysesthesia syndrome, stomatitis, rash, hypertension, hypothyroidism, musculoskeletal pain, decreased appetite, nausea, dysgeusia, abdominal pain, cough, and upper respiratory tract infection.

Tables 9 and 10 summarize adverse reactions and laboratory abnormalities, respectively, in CHECKMATE-9ER.

Table 9: Adverse Reactions in >15% of Patients Receiving Intravenous Nivolumab and Cabozantinib - CHECKMATE-9ER
Adverse Reaction | Intravenous Nivolumab and Cabozantinib (n=320) |  | Sunitinib (n=320)
Adverse Reaction | Grades 1-4 (%) | Grades 3-4 (%) | Grades 1-4 (%) | Grades 3-4 (%)
Gastrointestinal
Diarrhea | 64 | 7 | 47 | 4.4
Nausea | 27 | 0.6 | 31 | 0.3
Abdominal paina | 22 | 1.9 | 15 | 0.3
Vomiting | 17 | 1.9 | 21 | 0.3
Dyspepsiab | 15 | 0 | 22 | 0.3
General
Fatiguec | 51 | 8 | 50 | 8
Hepatobiliary
Hepatotoxicityd | 44 | 11 | 26 | 5
Skin and Subcutaneous Tissue
Palmar-plantar erythrodysesthesia syndrome | 40 | 8 | 41 | 8
Stomatitise | 37 | 3.4 | 46 | 4.4
Rashf | 36 | 3.1 | 14 | 0
Pruritus | 19 | 0.3 | 4.4 | 0
Vascular
Hypertensiong | 36 | 13 | 39 | 14
Endocrine
Hypothyroidismh | 34 | 0.3 | 30 | 0.3
Musculoskeletal and Connective Tissue
Musculoskeletal paini | 33 | 3.8 | 29 | 3.1
Arthralgia | 18 | 0.3 | 9 | 0.3
Metabolism and Nutrition
Decreased appetite | 28 | 1.9 | 20 | 1.3
Nervous System
Dysgeusia | 24 | 0 | 22 | 0
Headache | 16 | 0 | 12 | 0.6
Respiratory, Thoracic and Mediastinal
Coughj | 20 | 0.3 | 17 | 0
Dysphonia | 17 | 0.3 | 3.4 | 0
Infections and Infestations
Upper respiratory tract infectionk | 20 | 0.3 | 8 | 0.3
Toxicity was graded per NCI CTCAE v4.
a Includes abdominal discomfort, abdominal pain lower, abdominal pain upper.
b Includes gastroesophageal reflux disease.
c Includes asthenia.
d Includes hepatotoxicity, ALT increased, AST increased, blood alkaline phosphatase increased, gamma-glutamyl transferase increased, autoimmune hepatitis, blood bilirubin increased, drug induced liver injury, hepatic enzyme increased, hepatitis, hyperbilirubinemia, liver function test increased, liver function test abnormal, transaminases increased, hepatic failure.
e Includes mucosal inflammation, aphthous ulcer, mouth ulceration.
f Includes dermatitis, dermatitis acneiform, dermatitis bullous, exfoliative rash, rash erythematous, rash follicular, rash macular, rash maculo-papular, rash papular, rash pruritic.
g Includes blood pressure increased, blood pressure systolic increased.
h Includes primary hypothyroidism.
i Includes back pain, bone pain, musculoskeletal chest pain, musculoskeletal discomfort, myalgia, neck pain, pain in extremity, spinal pain.
j Includes productive cough.
k Includes nasopharyngitis, pharyngitis, rhinitis.

Table 10: Laboratory Values Worsening from Baselinea Occurring in >20% of Patients on Intravenous Nivolumab and Cabozantinib - CHECKMATE-9ER
Laboratory Abnormality | Intravenous Nivolumab and Cabozantinib |  | Sunitinib
Laboratory Abnormality | Grades 1-4 (%) | Grades 3-4 (%) | Grades 1-4 (%) | Grades 3-4 (%)
Chemistry
Increased ALT | 79 | 9.8 | 39 | 3.5
Increased AST | 77 | 7.9 | 57 | 2.6
Hypophosphatemia | 69 | 28 | 48 | 10
Hypocalcemia | 54 | 1.9 | 24 | 0.6
Hypomagnesemia | 47 | 1.3 | 25 | 0.3
Hyperglycemia | 44 | 3.5 | 44 | 1.7
Hyponatremia | 43 | 11 | 36 | 12
Increased lipase | 41 | 14 | 38 | 13
Increased amylase | 41 | 10 | 28 | 6
Increased alkaline phosphatase | 41 | 2.8 | 37 | 1.6
Increased creatinine | 39 | 1.3 | 42 | 0.6
Hyperkalemia | 35 | 4.7 | 27 | 1
Hypoglycemia | 26 | 0.8 | 14 | 0.4
Hematology
Lymphopenia | 42 | 6.6 | 45 | 10
Thrombocytopenia | 41 | 0.3 | 70 | 9.7
Anemia | 37 | 2.5 | 61 | 4.8
Leukopenia | 37 | 0.3 | 66 | 5.1
Neutropenia | 35 | 3.2 | 67 | 12
a Each test incidence is based on the number of patients who had both baseline and at least one on-study laboratory measurement available: intravenous nivolumab and cabozantinib group (range: 170 to 317 patients) and sunitinib group (range: 173 to 311 patients).

Previously Treated Renal Cell Carcinoma

CHECKMATE-025

The safety of intravenous nivolumab was evaluated in CHECKMATE-025, a randomized open-label trial in 803 patients with advanced RCC who had experienced disease progression during or after at least one anti-angiogenic treatment regimen received intravenous nivolumab 3 mg/kg over 60 minutes by intravenous infusion every 2 weeks (n=406) or everolimus 10 mg daily (n=397) [see Clinical Studies (14.1)]. The median duration of treatment was 5.5 months (range: 1 day to 29.6+ months) in intravenous nivolumab-treated patients and 3.7 months (range: 6 days to 25.7+ months) in everolimus-treated patients.

Rate of death on treatment or within 30 days of the last dose was 4.7% on the intravenous nivolumab arm. Serious adverse reactions occurred in 47% of patients receiving intravenous nivolumab. Study therapy was discontinued for adverse reactions in 16% of intravenous nivolumab patients. Forty-four percent (44%) of patients receiving intravenous nivolumab had a dose interruption for an adverse reaction.

The most frequent serious adverse reactions in at least 2% of patients were: acute kidney injury, pleural effusion, pneumonia, diarrhea, and hypercalcemia. The most common adverse reactions (≥20%) were fatigue, cough, nausea, rash, dyspnea, diarrhea, constipation, decreased appetite, back pain, and arthralgia. The most common laboratory abnormalities which have worsened compared to baseline in ≥30% of patients include increased creatinine, lymphopenia, anemia, increased AST, increased alkaline phosphatase, hyponatremia, increased triglycerides, and hyperkalemia. In addition, among patients with TSH < ULN at baseline, a greater proportion of patients experienced a treatment-emergent elevation of TSH > ULN in the intravenous nivolumab group compared to the everolimus group (26% and 14%, respectively).

Tables 11 and 12 summarize adverse reactions and laboratory abnormalities, respectively, in CHECKMATE-025.

Table 11: Adverse Reactions in >15% of Patients Receiving Intravenous Nivolumab - CHECKMATE-025
Adverse Reaction | Intravenous Nivolumab (n=406) |  | Everolimus (n=397)
Adverse Reaction | Grades 1-4 (%) | Grades 3-4 (%) | Grades 1-4 (%) | Grades 3-4 (%)
Adverse Reaction | 98 | 56 | 96 | 62
General
Fatiguea | 56 | 6 | 57 | 7
Pyrexia | 17 | 0.7 | 20 | 0.8
Respiratory, Thoracic and Mediastinal
Cough/productive cough | 34 | 0 | 38 | 0.5
Dyspnea/exertional dyspnea | 27 | 3 | 31 | 2
Upper respiratory infectionb | 18 | 0 | 11 | 0
Gastrointestinal
Nausea | 28 | 0.5 | 29 | 1
Diarrheac | 25 | 2.2 | 32 | 1.8
Constipation | 23 | 0.5 | 18 | 0.5
Vomiting | 16 | 0.5 | 16 | 0.5
Skin and Subcutaneous Tissue
Rashd | 28 | 1.5 | 36 | 1
Pruritus/generalized pruritus | 19 | 0 | 14 | 0
Metabolism and Nutrition
Decreased appetite | 23 | 1.2 | 30 | 1.5
Musculoskeletal and Connective Tissue
Arthralgia | 20 | 1 | 14 | 0.5
Back pain | 21 | 3.4 | 16 | 2.8
Toxicity was graded per NCI CTCAE v4.
a Includes asthenia, decreased activity, fatigue, and malaise.
b Includes nasopharyngitis, pharyngitis, rhinitis, and viral upper respiratory infection (URI).
c Includes colitis, enterocolitis, and gastroenteritis.
d Includes dermatitis, acneiform dermatitis, erythematous rash, generalized rash, macular rash, maculopapular rash, papular rash, pruritic rash, erythema multiforme, and erythema.

Other clinically important adverse reactions in CHECKMATE-025 were:

General Disorders and Administration Site Conditions: peripheral edema/edema

Gastrointestinal Disorders: abdominal pain/discomfort

Musculoskeletal and Connective Tissue Disorders: extremity pain, musculoskeletal pain

Nervous System Disorders: headache/migraine, peripheral neuropathy

Investigations: weight decreased

Skin Disorders: palmar-plantar erythrodysesthesia

Table 12: Laboratory Values Worsening from Baselinea Occurring in >15% of Patients on Intravenous Nivolumab - CHECKMATE-025
Laboratory Abnormality | Intravenous Nivolumab |  | Everolimus
Laboratory Abnormality | Grades 1-4 (%) | Grades 3-4 (%) | Grades 1-4 (%) | Grades 3-4 (%)
Hematology
Lymphopenia | 42 | 6 | 53 | 11
Anemia | 39 | 8 | 69 | 16
Chemistry
Increased creatinine | 42 | 2 | 45 | 1.6
Increased AST | 33 | 2.8 | 39 | 1.6
Increased alkaline phosphatase | 32 | 2.3 | 32 | 0.8
Hyponatremia | 32 | 7 | 26 | 6
Hyperkalemia | 30 | 4 | 20 | 2.1
Hypocalcemia | 23 | 0.9 | 26 | 1.3
Increased ALT | 22 | 3.2 | 31 | 0.8
Hypercalcemia | 19 | 3.2 | 6 | 0.3
Lipids
Increased triglycerides | 32 | 1.5 | 67 | 11
Increased cholesterol | 21 | 0.3 | 55 | 1.4
a Each test incidence is based on the number of patients who had both baseline and at least one on-study laboratory measurement available: intravenous nivolumab group (range: 259 to 401 patients) and everolimus group (range: 257 to 376 patients).

Unresectable or Metastatic Melanoma

Previously Treated Metastatic Melanoma

CHECKMATE-037

The safety of intravenous nivolumab was evaluated in CHECKMATE-037, a randomized, open-label trial in 370 patients with unresectable or metastatic melanoma [see Clinical Studies (14.2)]. Patients had documented disease progression following treatment with ipilimumab and, if BRAF V600 mutation positive, a BRAF inhibitor. The trial excluded patients with autoimmune disease, prior ipilimumab-related Grade 4 adverse reactions (except for endocrinopathies) or Grade 3 ipilimumab-related adverse reactions that had not resolved or were inadequately controlled within 12 weeks of the initiating event, patients with a condition requiring chronic systemic treatment with corticosteroids (>10 mg daily prednisone equivalent) or other immunosuppressive medications, a positive test for hepatitis B or C, and a history of HIV. Patients received intravenous nivolumab 3 mg/kg by intravenous infusion over 60 minutes every 2 weeks (n=268) or investigator’s choice of chemotherapy (n=102): dacarbazine 1000 mg/m^2 intravenously every 3 weeks or carboplatin AUC 6 mg/mL/min and paclitaxel 175 mg/m^2 intravenously every 3 weeks. The median duration of exposure was 5.3 months (range: 1 day to 13.8+ months) in intravenous nivolumab‑treated patients and was 2 months (range: 1 day to 9.6+ months) in chemotherapy-treated patients. In this ongoing trial, 24% of patients received intravenous nivolumab for >6 months and 3% of patients received intravenous nivolumab for >1 year.

The population characteristics in the intravenous nivolumab group and the chemotherapy group were similar: 66% male, median age 59.5 years, 98% White, baseline Eastern Cooperative Oncology Group (ECOG) performance status 0 (59%) or 1 (41%), 74% with M1c stage disease, 73% with cutaneous melanoma, 11% with mucosal melanoma, 73% received two or more prior therapies for advanced or metastatic disease, and 18% had brain metastasis. There were more patients in the intravenous nivolumab group with elevated lactate dehydrogenase (LDH) at baseline (51% vs. 38%).

Serious adverse reactions occurred in 41% of patients receiving intravenous nivolumab. Intravenous nivolumab was discontinued for adverse reactions in 9% of patients. Twenty-six percent of patients receiving intravenous nivolumab had a dose interruption for an adverse reaction. Grade 3 and 4 adverse reactions occurred in 42% of patients receiving intravenous nivolumab. The most frequent Grade 3 and 4 adverse reactions reported in 2% to <5% of patients receiving intravenous nivolumab were abdominal pain, hyponatremia, increased aspartate aminotransferase, and increased lipase. The most common adverse reaction (reported in ≥20% of patients) was rash.

Tables 13 and 14 summarize the adverse reactions and laboratory abnormalities, respectively, in CHECKMATE-037.

Table 13: Adverse Reactions Occurring in ≥10% of Intravenous Nivolumab-Treated Patients and at a Higher Incidence than in the Chemotherapy Arm (Between Arm Difference of ≥5% All Grades or ≥2% Grades 3-4) - CHECKMATE-037
Adverse Reaction | Intravenous Nivolumab (n=268) |  | Chemotherapy (n=102)
Adverse Reaction | All Grades (%) | Grades 3-4 (%) | All Grades (%) | Grades 3-4 (%)
Skin and Subcutaneous Tissue
Rasha | 21 | 0.4 | 7 | 0
Pruritus | 19 | 0 | 3.9 | 0
Respiratory, Thoracic and Mediastinal
Cough | 17 | 0 | 6 | 0
Infections
Upper respiratory tract infectionb | 11 | 0 | 2 | 0
General
Peripheral edema | 10 | 0 | 5 | 0
Toxicity was graded per NCI CTCAE v4.
a Includes maculopapular rash, erythematous rash, pruritic rash, follicular rash, macular rash, papular rash, pustular rash, vesicular rash, and acneiform dermatitis.
b Includes rhinitis, pharyngitis, and nasopharyngitis.

Clinically important adverse reactions in <10% of patients who received intravenous nivolumab were:

Cardiac Disorders: ventricular arrhythmia

Eye Disorders: iridocyclitis

General Disorders and Administration Site Conditions: infusion-related reactions

Investigations: increased amylase, increased lipase

Nervous System Disorders: dizziness, peripheral and sensory neuropathy

Skin and Subcutaneous Tissue Disorders: exfoliative dermatitis, erythema multiforme, vitiligo, psoriasis

Table 14: Laboratory Abnormalities Worsening from Baselinea Occurring in ≥10% of Intravenous Nivolumab-Treated Patients and at a Higher Incidence than in the Chemotherapy Arm (Between Arm Difference of ≥5% All Grades or ≥2% Grades 3-4) - CHECKMATE-037
Laboratory Abnormality | Intravenous Nivolumab |  | Chemotherapy
Laboratory Abnormality | All Grades (%) | Grades 3-4 (%) | All Grades (%) | Grades 3-4 (%)
Increased AST | 28 | 2.4 | 12 | 1
Hyponatremia | 25 | 5 | 18 | 1.1
Increased alkaline phosphatase | 22 | 2.4 | 13 | 1.1
Increased ALT | 16 | 1.6 | 5 | 0
Hyperkalemia | 15 | 2 | 6 | 0
a Each test incidence is based on the number of patients who had both baseline and at least one on-study laboratory measurement available: intravenous nivolumab group (range: 252 to 256 patients) and chemotherapy group (range: 94 to 96 patients).

Previously Untreated Metastatic Melanoma

CHECKMATE-066

The safety of intravenous nivolumab was also evaluated in CHECKMATE-066, a randomized, double-blind, active‑controlled trial in 411 previously untreated patients with BRAF V600 wild-type unresectable or metastatic melanoma [see Clinical Studies (14.2)]. The trial excluded patients with autoimmune disease and patients requiring chronic systemic treatment with corticosteroids (>10 mg daily prednisone equivalent) or other immunosuppressive medications. Patients received intravenous nivolumab 3 mg/kg by intravenous infusion over 60 minutes every 2 weeks (n=206) or dacarbazine 1000 mg/m^2 intravenously every 3 weeks (n=205). The median duration of exposure was 6.5 months (range: 1 day to 16.6 months) in intravenous nivolumab-treated patients. In this trial, 47% of patients received intravenous nivolumab for >6 months and 12% of patients received intravenous nivolumab for >1 year.

The trial population characteristics in the intravenous nivolumab group and dacarbazine group: 59% male, median age 65 years, 99.5% White, 61% with M1c stage disease, 74% with cutaneous melanoma, 11% with mucosal melanoma, 4% with brain metastasis, and 37% with elevated LDH at baseline. There were more patients in the intravenous nivolumab group with ECOG performance status 0 (71% vs. 59%).

Serious adverse reactions occurred in 36% of patients receiving intravenous nivolumab. Adverse reactions led to permanent discontinuation of intravenous nivolumab in 7% of patients and dose interruption in 26% of patients; no single type of adverse reaction accounted for the majority of intravenous nivolumab discontinuations. Grade 3 and 4 adverse reactions occurred in 41% of patients receiving intravenous nivolumab.

The most frequent Grade 3 and 4 adverse reactions reported in ≥2% of patients receiving intravenous nivolumab were increased gamma-glutamyl transferase (3.9%) and diarrhea (3.4%). The most common adverse reactions (reported in ≥20% of patients and at a higher incidence than in the dacarbazine arm) were fatigue, musculoskeletal pain, rash, and pruritus.

Tables 15 and 16 summarize selected adverse reactions and laboratory abnormalities, respectively, in CHECKMATE-066.

Table 15: Adverse Reactions Occurring in ≥10% of Intravenous Nivolumab-Treated Patients and at a Higher Incidence than in the Dacarbazine Arm (Between Arm Difference of ≥5% All Grades or ≥2% Grades 3-4) - CHECKMATE-066
Adverse Reaction | Intravenous Nivolumab (n=206) |  | Dacarbazine (n=205)
Adverse Reaction | All Grades (%) | Grades 3-4 (%) | All Grades (%) | Grades 3-4 (%)
General
Fatigue | 49 | 1.9 | 39 | 3.4
Edemaa | 12 | 1.5 | 4.9 | 0
Musculoskeletal and Connective Tissue
Musculoskeletal painb | 32 | 2.9 | 25 | 2.4
Skin and Subcutaneous Tissue
Rashc | 28 | 1.5 | 12 | 0
Pruritus | 23 | 0.5 | 12 | 0
Vitiligo | 11 | 0 | 0.5 | 0
Erythema | 10 | 0 | 2.9 | 0
Infections
Upper respiratory tract infectiond | 17 | 0 | 6 | 0
Toxicity was graded per NCI CTCAE v4.
a Includes periorbital edema, face edema, generalized edema, gravitational edema, localized edema, peripheral edema, pulmonary edema, and lymphedema.
b Includes back pain, bone pain, musculoskeletal chest pain, musculoskeletal discomfort, myalgia, neck pain, pain in extremity, pain in jaw, and spinal pain.
c Includes maculopapular rash, erythematous rash, pruritic rash, follicular rash, macular rash, papular rash, pustular rash, vesicular rash, dermatitis, allergic dermatitis, exfoliative dermatitis, acneiform dermatitis, drug eruption, and skin reaction.
d Includes rhinitis, viral rhinitis, pharyngitis, and nasopharyngitis.

Clinically important adverse reactions in <10% of patients who received intravenous nivolumab were:

Nervous System Disorders: peripheral neuropathy

Table 16: Laboratory Abnormalities Worsening from Baselinea Occurring in ≥10% of Intravenous Nivolumab-Treated Patients and at a Higher Incidence than in the Dacarbazine Arm (Between Arm Difference of ≥5% All Grades or ≥2% Grades 3-4) - CHECKMATE-066
Laboratory Abnormality | Intravenous Nivolumab |  | Dacarbazine
Laboratory Abnormality | All Grades (%) | Grades 3-4 (%) | All Grades (%) | Grades 3-4 (%)
Increased ALT | 25 | 3 | 19 | 0.5
Increased AST | 24 | 3.6 | 19 | 0.5
Increased alkaline phosphatase | 21 | 2.6 | 14 | 1.6
Increased bilirubin | 13 | 3.1 | 6 | 0
a Each test incidence is based on the number of patients who had both baseline and at least one on-study laboratory measurement available: intravenous nivolumab group (range: 194 to 197 patients) and dacarbazine group (range: 186 to 193 patients).

CHECKMATE-067

The safety of intravenous nivolumab, administered with ipilimumab or as a single agent, was evaluated in CHECKMATE-067, a randomized (1:1:1), double-blind trial in 937 patients with previously untreated, unresectable or metastatic melanoma [see Clinical Studies (14.2)]. The trial excluded patients with autoimmune disease, a medical condition requiring systemic treatment with corticosteroids (more than 10 mg daily prednisone equivalent) or other immunosuppressive medication within 14 days of the start of study therapy, a positive test result for hepatitis B or C, or a history of HIV.

Patients were randomized to receive:

- Intravenous nivolumab 1 mg/kg over 60 minutes with ipilimumab 3 mg/kg by intravenous infusion every 3 weeks for 4 doses followed by intravenous nivolumab as a single agent at a dose of 3 mg/kg by intravenous infusion over 60 minutes every 2 weeks (nivolumab and ipilimumab arm; n=313), or
- Intravenous nivolumab 3 mg/kg by intravenous infusion over 60 minutes every 2 weeks (nivolumab arm; n=313), or
- Ipilimumab 3 mg/kg by intravenous infusion every 3 weeks for up to 4 doses (ipilimumab arm; n=311).

The median duration of exposure to intravenous nivolumab was 2.8 months (range: 1 day to 36.4 months) for the intravenous nivolumab and ipilimumab arm and 6.6 months (range: 1 day to 36.0 months) for the intravenous nivolumab arm. In the intravenous nivolumab and ipilimumab arm, 39% were exposed to intravenous nivolumab for ≥6 months and 30% exposed for >1 year. In the intravenous nivolumab arm, 53% were exposed for ≥6 months and 40% for >1 year.

The population characteristics were: 65% male, median age 61 years, 97% White, baseline ECOG performance status 0 (73%) or 1 (27%), 93% with American Joint Committee on Cancer (AJCC) Stage IV disease, 58% with M1c stage disease; 36% with elevated LDH at baseline, 4% with a history of brain metastasis, and 22% had received adjuvant therapy.

Serious adverse reactions (74% and 44%), adverse reactions leading to permanent discontinuation (47% and 18%) or to dosing delays (58% and 36%), and Grade 3 or 4 adverse reactions (72% and 51%) all occurred more frequently in the intravenous nivolumab and ipilimumab arm relative to the intravenous nivolumab arm.

The most frequent (≥10%) serious adverse reactions in the intravenous nivolumab and ipilimumab arm and the intravenous nivolumab arm, respectively, were diarrhea (13% and 2.2%), colitis (10% and 1.9%), and pyrexia (10% and 1%). The most frequent adverse reactions leading to discontinuation of both drugs in the intravenous nivolumab and ipilimumab arm and of intravenous nivolumab in the intravenous nivolumab arm, respectively, were colitis (10% and 0.6%), diarrhea (8% and 2.2%), increased ALT (4.8% and 1%), increased AST (4.5% and 0.6%), and pneumonitis (1.9% and 0.3%).

The most common (≥20%) adverse reactions in the intravenous nivolumab and ipilimumab arm were fatigue, diarrhea, rash, nausea, pyrexia, pruritus, musculoskeletal pain, vomiting, decreased appetite, cough, headache, dyspnea, upper respiratory tract infection, arthralgia, and increased transaminases. The most common (≥20%) adverse reactions in the intravenous nivolumab arm were fatigue, rash, musculoskeletal pain, diarrhea, nausea, cough, pruritus, upper respiratory tract infection, decreased appetite, headache, constipation, arthralgia, and vomiting.

Tables 17 and 18 summarize the incidence of adverse reactions and laboratory abnormalities, respectively, in CHECKMATE-067.

Table 17: Adverse Reactions Occurring in ≥10% of Patients on the Intravenous Nivolumab and Ipilimumab Arm or the Intravenous Nivolumab Arm and at a Higher Incidence than in the Ipilimumab Arm (Between Arm Difference of ≥5% All Grades or ≥2% Grades 3-4) - CHECKMATE-067
Adverse Reaction | Intravenous Nivolumab and Ipilimumab (n=313) |  | Intravenous Nivolumab; (n=313) |  | Ipilimumab; (n=311)
Adverse Reaction | All Grades (%) | Grades 3-4 (%) | All Grades (%) | Grades 3-4 (%) | All Grades (%) | Grades 3-4 (%)
General
Fatiguea | 62 | 7 | 59 | 1.6 | 51 | 4.2
Pyrexia | 40 | 1.6 | 16 | 0 | 18 | 0.6
Gastrointestinal
Diarrhea | 54 | 11 | 36 | 5 | 47 | 7
Nausea | 44 | 3.8 | 30 | 0.6 | 31 | 1.9
Vomiting | 31 | 3.8 | 20 | 1 | 17 | 1.6
Skin and Subcutaneous Tissue
Rashb | 53 | 6 | 40 | 1.9 | 42 | 3.5
Vitiligo | 9 | 0 | 10 | 0.3 | 5 | 0
Musculoskeletal and Connective Tissue
Musculoskeletal painc | 32 | 2.6 | 42 | 3.8 | 36 | 1.9
Arthralgia | 21 | 0.3 | 21 | 1 | 16 | 0.3
Metabolism and Nutrition
Decreased appetite | 29 | 1.9 | 22 | 0 | 24 | 1.3
Respiratory, Thoracic and Mediastinal
Cough/productive cough | 27 | 0.3 | 28 | 0.6 | 22 | 0
Dyspnea/exertional dyspnea | 24 | 2.9 | 18 | 1.3 | 17 | 0.6
Infections
Upper respiratory tract infectiond | 23 | 0 | 22 | 0.3 | 17 | 0
Endocrine
Hypothyroidism | 19 | 0.6 | 11 | 0 | 5 | 0
Hyperthyroidism | 11 | 1.3 | 6 | 0 | 1 | 0
Investigations
Decreased weight | 12 | 0 | 7 | 0 | 7 | 0.3
Vascular
Hypertensione | 7 | 2.2 | 11 | 5 | 9 | 2.3
Toxicity was graded per NCI CTCAE v4.
a Includes asthenia and fatigue.
b Includes pustular rash, dermatitis, acneiform dermatitis, allergic dermatitis, atopic dermatitis, bullous dermatitis, exfoliative dermatitis, psoriasiform dermatitis, drug eruption, exfoliative rash, erythematous rash, generalized rash, macular rash, maculopapular rash, morbilliform rash, papular rash, papulosquamous rash, and pruritic rash.
c Includes back pain, bone pain, musculoskeletal chest pain, musculoskeletal discomfort, myalgia, neck pain, pain in extremity, and spinal pain.
d Includes upper respiratory tract infection, nasopharyngitis, pharyngitis, and rhinitis.
e Includes hypertension and blood pressure increased.

Clinically important adverse reactions in <10% of patients who received intravenous nivolumab with ipilimumab or intravenous nivolumab as a single agent were:

Gastrointestinal Disorders: stomatitis, intestinal perforation

Skin and Subcutaneous Tissue Disorders: vitiligo

Musculoskeletal and Connective Tissue Disorders: myopathy, Sjogren’s syndrome, spondyloarthropathy, myositis (including polymyositis)

Nervous System Disorders: neuritis, peroneal nerve palsy

Table 18: Laboratory Abnormalities Worsening from Baselinea Occurring in ≥20% of Patients Treated with Intravenous Nivolumab with Ipilimumab or Single-Agent Intravenous Nivolumab and at a Higher Incidence than in the Ipilimumab Arm (Between Arm Difference of ≥5% All Grades or ≥2% Grades 3-4) - CHECKMATE-067
Laboratory Abnormality | Intravenous Nivolumab and Ipilimumab |  | Intravenous Nivolumab |  | Ipilimumab
Laboratory Abnormality | All Grades (%) | Grade 3-4 (%) | All Grades (%) | Grade 3-4 (%) | All Grades (%) | Grade 3-4 (%)
Chemistry
Increased ALT | 55 | 16 | 25 | 3 | 29 | 2.7
Hyperglycemia | 53 | 5.3 | 46 | 7 | 26 | 0
Increased AST | 52 | 13 | 29 | 3.7 | 29 | 1.7
Hyponatremia | 45 | 10 | 22 | 3.3 | 26 | 7
Increased lipase | 43 | 22 | 32 | 12 | 24 | 7
Increased alkaline phosphatase | 41 | 6 | 27 | 2 | 23 | 2
Hypocalcemia | 31 | 1.1 | 15 | 0.7 | 20 | 0.7
Increased amylase | 27 | 10 | 19 | 2.7 | 15 | 1.6
Increased creatinine | 26 | 2.7 | 19 | 0.7 | 17 | 1.3
Hematology
Anemia | 52 | 2.7 | 41 | 2.6 | 41 | 6
Lymphopenia | 39 | 5 | 41 | 4.9 | 29 | 4
a Each test incidence is based on the number of patients who had both baseline and at least one on-study laboratory measurement available: intravenous nivolumab and ipilimumab (range: 75 to 297); intravenous nivolumab (range: 81 to 306); ipilimumab (range: 61 to 301).

Adjuvant Treatment of Melanoma

CHECKMATE-76K

The safety of intravenous nivolumab as a single agent was evaluated in CHECKMATE-76K, a randomized (2:1), double-blind trial in 788 patients with completely resected Stage IIB/C melanoma who received intravenous nivolumab 480 mg by intravenous infusion over 30 minutes every 4 weeks (n=524) or placebo by intravenous infusion over 30 minutes every 4 weeks (n=264) for up to 1 year [see Clinical Studies (14.3)]. The median duration of exposure was 11 months in patients treated with intravenous nivolumab and 11 months in patients treated with placebo.

Serious adverse reactions occurred in 18% of patients treated with intravenous nivolumab. A fatal adverse reaction occurred in 1 (0.2%) patient (heart failure and acute kidney injury). Permanent discontinuation of intravenous nivolumab due to an adverse reaction occurred in 17% of patients. Adverse reactions which resulted in permanent discontinuation of intravenous nivolumab in >1% of patients included diarrhea (1.1%), arthralgia (1.7%), and rash (1.7%).

Dosage interruptions of intravenous nivolumab due to an adverse reaction occurred in 25% of patients. Adverse reactions which required dosage interruption in >1% of patients included COVID-19 infection, infusion related reaction, diarrhea, arthralgia, and increased ALT.

The most common adverse reactions (reported in ≥20% of patients) were fatigue, musculoskeletal pain, rash, diarrhea, and pruritus.

Tables 19 and 20 summarize the adverse reactions and laboratory abnormalities, respectively, in CHECKMATE-76K.

Table 19: Adverse Reactions Occurring in ≥10% of Patients Treated with Intravenous Nivolumab - CHECKMATE-76K
Adverse Reaction | Intravenous Nivolumab (n=524) |  | Placebo (n=264)
Adverse Reaction | All Grades (%) | Grades 3-4 (%) | All Grades (%) | Grades 3-4 (%)
General
Fatiguea | 36 | 0.4 | 34 | 0.4
Musculoskeletal and connective tissue
Musculoskeletal painb | 30 | 0.4 | 26 | 0.4
Skin and Subcutaneous Tissue
Rashc | 28 | 1.1 | 15 | 0.4
Pruritus | 20 | 0.2 | 11 | 0
Gastrointestinal
Diarrhead | 23 | 1.3 | 16 | 0
Nausea | 14 | 0 | 11 | 0
Endocrine
Hypothyroidisme | 14 | 0 | 2.3 | 0
Nervous system
Headachef | 12 | 0.2 | 14 | 0.8
Toxicity was graded per NCI CTCAE v5.
a Includes asthenia.
b Includes arthralgia, arthritis, back pain, bone pain, musculoskeletal chest pain, musculoskeletal discomfort, musculoskeletal stiffness, myalgia, neck pain, non-cardiac chest pain, spinal pain, pain in extremity.
c Includes dermatitis, dermatitis acneiform, dyshidrotic eczema, eczema, eczema asteatotic, eyelid rash, genital rash, pemphigoid, penile rash, rash erythematous, rash follicular, rash macular, rash maculo-papular, rash papular, rash pruritic, rash pustular, rash vesicular, skin exfoliation, toxic skin eruption.
d Includes autoimmune colitis, colitis, diarrhea, enteritis, enterocolitis
e Includes autoimmune hypothyroidism, blood thyroid stimulating hormone increased.
f Includes cluster headache, migraine.

Table 20: Laboratory Abnormalities Worsening from Baselinea Occurring in ≥10% of Intravenous Nivolumab-Treated Patients - CHECKMATE-76K
Laboratory Abnormality | Intravenous Nivolumab; (n=524) |  | Placebo; (n=264)
Laboratory Abnormality | All Grades (%) | Grades 3-4 (%) | All Grades (%) | Grades 3-4 (%)
Hematology
Anemia | 19 | 0 | 14 | 0
Lymphopenia | 17 | 1.1 | 17 | 1.7
Neutropenia | 10 | 0 | 10 | 0.4
Chemistry
AST increased | 25 | 2.2 | 16 | 0.4
Lipase increased | 22 | 2.9 | 21 | 2.3
ALT increased | 20 | 2.1 | 15 | 0.4
Amylase increased | 17 | 0.4 | 9 | 0
Creatinine increased | 15 | 0.4 | 13 | 0
Sodium decreased | 13 | 0.6 | 11 | 0.4
Potassium increased | 13 | 1 | 15 | 1.1
a Each test incidence is based on the number of patients who had both baseline and at least one on-study laboratory measurement available: intravenous nivolumab group (range: 262 to 513 patients) and placebo group (range: 138 to 261 patients).

CHECKMATE-238

The safety of intravenous nivolumab as a single agent was evaluated in CHECKMATE-238, a randomized (1:1), double-blind trial in 905 patients with completely resected Stage IIIB/C or Stage IV melanoma received intravenous nivolumab 3 mg/kg by intravenous infusion over 60 minutes every 2 weeks (n=452) or ipilimumab 10 mg/kg by intravenous infusion every 3 weeks for 4 doses then every 12 weeks beginning at Week 24 for up to 1 year (n=453) [see Clinical Studies (14.3)]. The median duration of exposure was 11.5 months in intravenous nivolumab‑treated patients and was 2.7 months in ipilimumab-treated patients. In this ongoing trial, 74% of patients received intravenous nivolumab for >6 months.

Serious adverse reactions occurred in 18% of intravenous nivolumab-treated patients. Study therapy was discontinued for adverse reactions in 9% of intravenous nivolumab-treated patients and 42% of ipilimumab-treated patients. Twenty-eight percent of intravenous nivolumab-treated patients had at least one omitted dose for an adverse reaction. Grade 3 or 4 adverse reactions occurred in 25% of intravenous nivolumab-treated patients.

The most frequent Grade 3 and 4 adverse reactions reported in ≥2% of intravenous nivolumab-treated patients were diarrhea and increased lipase and amylase. The most common adverse reactions (at least 20%) were fatigue, diarrhea, rash, musculoskeletal pain, pruritus, headache, nausea, upper respiratory infection, and abdominal pain. The most common immune-mediated adverse reactions were rash (16%), diarrhea/colitis (6%), and hepatitis (3%).

Tables 21 and 22 summarize the adverse reactions and laboratory abnormalities, respectively, in CHECKMATE-238.

Table 21: Adverse Reactions Occurring in ≥10% of Intravenous Nivolumab-Treated Patients - CHECKMATE-238
Adverse Reaction | Intravenous Nivolumab (n=452) |  | Ipilimumab 10 mg/kg (n=453)
Adverse Reaction | All Grades (%) | Grades 3-4 (%) | All Grades (%) | Grades 3-4 (%)
General
Fatiguea | 57 | 0.9 | 55 | 2.4
Gastrointestinal
Diarrhea | 37 | 2.4 | 55 | 11
Nausea | 23 | 0.2 | 28 | 0
Abdominal painb | 21 | 0.2 | 23 | 0.9
Constipation | 10 | 0 | 9 | 0
Skin and Subcutaneous Tissue
Rashc | 35 | 1.1 | 47 | 5.3
Pruritus | 28 | 0 | 37 | 1.1
Musculoskeletal and Connective Tissue
Musculoskeletal paind | 32 | 0.4 | 27 | 0.4
Arthralgia | 19 | 0.4 | 13 | 0.4
Nervous System
Headache | 23 | 0.4 | 31 | 2.0
Dizzinesse | 11 | 0 | 8 | 0
Infections
Upper respiratory tract infectionf | 22 | 0 | 15 | 0.2
Respiratory, Thoracic and Mediastinal
Cough/productive cough | 19 | 0 | 19 | 0
Dyspnea/exertional dyspnea | 10 | 0.4 | 10 | 0.2
Endocrine
Hypothyroidismg | 12 | 0.2 | 7.5 | 0.4
Toxicity was graded per NCI CTCAE v4.
a Includes asthenia.
b Includes abdominal discomfort, lower abdominal pain, upper abdominal pain, and abdominal tenderness.
c Includes dermatitis described as acneiform, allergic, bullous, or exfoliative and rash described as generalized, erythematous, macular, papular, maculopapular, pruritic, pustular, vesicular, or butterfly, and drug eruption.
d Includes back pain, bone pain, musculoskeletal chest pain, musculoskeletal discomfort, myalgia, neck pain, spinal pain, and pain in extremity.
e Includes postural dizziness and vertigo.
f Includes upper respiratory tract infection including viral respiratory tract infection, lower respiratory tract infection, rhinitis, pharyngitis, and nasopharyngitis.
g Includes secondary hypothyroidism and autoimmune hypothyroidism.

Table 22: Laboratory Abnormalities Worsening from Baselinea Occurring in ≥10% of Intravenous Nivolumab-Treated Patients - CHECKMATE-238
Laboratory Abnormality | Intravenous Nivolumab |  | Ipilimumab 10 mg/kg
Laboratory Abnormality | All Grades (%) | Grades 3-4 (%) | All Grades (%) | Grades 3-4 (%)
Hematology
Lymphopenia | 27 | 0.4 | 12 | 0.9
Anemia | 26 | 0 | 34 | 0.5
Leukopenia | 14 | 0 | 2.7 | 0.2
Neutropenia | 13 | 0 | 6 | 0.5
Chemistry
Increased Lipase | 25 | 7 | 23 | 9
Increased ALT | 25 | 1.8 | 40 | 12
Increased AST | 24 | 1.3 | 33 | 9
Increased Amylase | 17 | 3.3 | 13 | 3.1
Hyponatremia | 16 | 1.1 | 22 | 3.2
Hyperkalemia | 12 | 0.2 | 9 | 0.5
Increased Creatinine | 12 | 0 | 13 | 0
Hypocalcemia | 10 | 0.7 | 16 | 0.5
a Each test incidence is based on the number of patients who had both baseline and at least one on-study laboratory measurement available: intravenous nivolumab group (range: 400 to 447 patients) and ipilimumab 10 mg/kg group (range: 392 to 443 patients).

Non-Small Cell Lung Cancer

Neoadjuvant Treatment of Resectable (Tumors ≥4 cm or Node Positive) Non-Small Cell Lung Cancer

CHECKMATE-816

The safety of intravenous nivolumab in combination with platinum-doublet chemotherapy was evaluated in CHECKMATE-816, a randomized, open-label, multicenter trial in patients with resectable NSCLC [see Clinical Studies (14.4)]. Patients received either intravenous nivolumab 360 mg administered in combination with platinum-doublet chemotherapy administered every 3 weeks for 3 cycles; or platinum-doublet chemotherapy administered every 3 weeks for 3 cycles.

The median age of patients who received intravenous nivolumab in combination with platinum-doublet chemotherapy or platinum-doublet chemotherapy was 65 years (range: 34 – 84); 72% male; 47% White, 50% Asian, and 2% Black/African American.

Serious adverse reactions occurred in 30% of patients who were treated with intravenous nivolumab in combination with platinum-doublet chemotherapy. Serious adverse reactions in >2% included pneumonia and vomiting. No fatal adverse reactions occurred in patients who received intravenous nivolumab in combination with platinum-doublet chemotherapy.

Study therapy with intravenous nivolumab in combination with platinum-doublet chemotherapy was permanently discontinued for adverse reactions in 10% of patients and 30% had at least one treatment withheld for an adverse reaction. The most common adverse reactions (≥1%) resulting in permanent discontinuation of intravenous nivolumab in combination with platinum-doublet chemotherapy were anaphylactic reaction (1.7%), acute kidney injury (1.1%), rash (1.1%), and fatigue (1.1%).

The most common (>20%) adverse reactions were nausea, constipation, fatigue, decreased appetite, and rash. The most common Grade 3 or 4 laboratory abnormalities (≥2%) were neutropenia, hyperglycemia, leukopenia, lymphopenia, increased amylase, anemia, thrombocytopenia, and hyponatremia.

Tables 23 and 24 summarize selected adverse reactions and laboratory abnormalities, respectively, in CHECKMATE-816.

Table 23: Adverse Reactions in >10% of Patients with Early-Stage NSCLC Receiving Neoadjuvant Intravenous Nivolumab and Platinum-Doublet Chemotherapy in CHECKMATE-816
Adverse Reaction | Intravenous Nivolumab and Platinum-Doublet Chemotherapy (n=176) |  | Platinum-Doublet Chemotherapy (n=176)
Adverse Reaction | All Grades; (%) | Grades 3 or 4 (%) | All Grades; (%) | Grades 3 or 4 (%)
Gastrointestinal
Nausea | 38 | 0.6 | 45 | 1.1
Constipation | 34 | 0 | 32 | 1.1
Vomiting | 11 | 1.1 | 13 | 0.6
General
Fatiguea | 26 | 2.3 | 23 | 1.1
Malaise | 15 | 0.6 | 14 | 0.6
Metabolism and Nutrition
Decreased appetite | 20 | 1.1 | 23 | 2.3
Skin and Subcutaneous Tissue
Rashb | 20 | 2.3 | 7 | 0
Alopecia | 11 | 0 | 15 | 0
Nervous System
Peripheral neuropathyc | 13 | 0 | 6 | 0
Toxicity was graded per NCI CTCAE v4.
a Includes fatigue and asthenia.
b Includes rash, dermatitis, acneiform dermatitis, atopic dermatitis, bullous dermatitis, drug eruption, maculopapular rash, and pruritic rash.
c Includes peripheral neuropathy, dysesthesia, hypoesthesia, peripheral motor neuropathy, peripheral sensory neuropathy.

Table 24: Select Laboratory Values Worsening from Baselinea Occurring in >20% of Patients with Early-Stage NSCLC Receiving Neoadjuvant Intravenous Nivolumab and Platinum-Doublet Chemotherapy in CHECKMATE-816
Laboratory Abnormality | Intravenous Nivolumab and Platinum-Doublet Chemotherapya |  | Platinum-Doublet Chemotherapya
Laboratory Abnormality | All Grades; (%) | Grades 3 or 4 (%) | All Grades; (%) | Grades 3 or 4 (%)
Hematology
Anemia | 63 | 3.5 | 70 | 6
Neutropenia | 58 | 22 | 58 | 27
Leukopenia | 53 | 5 | 51 | 11
Lymphopenia | 38 | 4.7 | 31 | 1.8
Thrombocytopenia | 24 | 2.9 | 22 | 3
Chemistry
Hyperglycemia | 37 | 6 | 35 | 2.9
Hypomagnesemia | 25 | 1.2 | 29 | 1.2
Hyponatremia | 25 | 2.4 | 28 | 1.8
Increased amylase | 23 | 3.6 | 13 | 1.8
Increased ALT | 23 | 0 | 20 | 1.2
a Each test incidence is based on the number of patients who had both baseline and at least one on-study laboratory measurement available: intravenous nivolumab and platinum-doublet chemotherapy group (range: 73 to 171 patients) and platinum-doublet chemotherapy group (range: 68 to 171 patients).

Neoadjuvant and Adjuvant Treatment of Resectable (Tumors ≥4 cm or Node Positive) Non-Small Cell Lung Cancer

CHECKMATE-77T

The safety of intravenous nivolumab in combination with neoadjuvant platinum-doublet chemotherapy followed by surgery and continued adjuvant treatment with intravenous nivolumab as a single agent after surgery was evaluated in CHECKMATE-77T, a randomized, double-blind, multicenter trial in patients with previously untreated resectable Stage IIA (>4 cm) to IIIB (T3N2 or T4N2) NSCLC (per the AJCC Cancer Staging Manual 8th Edition) [see Clinical Studies (14.5)]. Patients with active autoimmune disease or a medical condition that required immunosuppression were ineligible. The median duration of exposure to intravenous nivolumab was 10.3 months (range: 1 day to 22.3 months).

The study population characteristics were: median age 66 years (range: 35 - 86); 71% male; 72% White, 25% Asian, 1.7% Black/African American, and 1.5% other race; and 6% Hispanic or Latino.

Adverse reactions occurring in patients with resectable NSCLC receiving intravenous nivolumab in combination with platinum-doublet chemotherapy, given as neoadjuvant treatment and followed as a single agent adjuvant treatment after surgery, were generally similar to those occurring in patients in other clinical trials across tumor types receiving intravenous nivolumab in combination with chemotherapy.

Neoadjuvant Phase of CHECKMATE-77T

A total of 228 patients received at least 1 dose of intravenous nivolumab in combination with platinum-doublet chemotherapy as neoadjuvant treatment and 230 patients received at least 1 dose of placebo in combination with platinum-doublet chemotherapy as neoadjuvant treatment.

Serious adverse reactions occurred in 21% of patients who received intravenous nivolumab in combination with platinum-doublet chemotherapy as neoadjuvant treatment; the most frequent (≥2%) serious adverse reactions was pneumonia. Fatal adverse reactions occurred in 2.2% of patients, due to cerebrovascular accident, COVID-19 infection, hemoptysis, pneumonia, and pneumonitis (0.4% each).

Permanent discontinuation of any study drug due to an adverse reaction occurred in 13% of patients who received intravenous nivolumab in combination with platinum-doublet chemotherapy as neoadjuvant treatment; the most frequent (≥1%) adverse reaction that led to permanent discontinuation of any study drug was peripheral sensory neuropathy (2.2%).

Of the 228 intravenous nivolumab-treated patients and 230 placebo-treated patients who received neoadjuvant treatment, 5.3% (n=12) and 3.5% (n=8), respectively, did not receive surgery due to adverse reactions. The adverse reactions that led to cancellation of surgery in intravenous nivolumab-treated patients were cerebrovascular accident, pneumonia, and colitis/diarrhea (2 patients each) and acute coronary syndrome, myocarditis, hemoptysis, pneumonitis, COVID-19, and myositis (1 patient each).

Of the 178 intravenous nivolumab-treated patients who received surgery, 4.5% (n=8) experienced delay of surgery (surgery more than 6 weeks from last neoadjuvant treatment) due to adverse reactions. Of the 178 placebo-treated patients who received surgery, 3.9% (n=7) experienced delay of surgery due to adverse reactions.

Of the 178 intravenous nivolumab-treated patients who received surgery, 7% (n=13) did not receive adjuvant treatment due to adverse reactions. Of the 178 placebo-treated patients who received surgery, 2.8% (n=5) did not receive adjuvant treatment due to adverse reactions.

Adjuvant Phase of CHECKMATE-77T

A total of 142 patients in the intravenous nivolumab arm and 152 patients in the placebo arm received at least 1 dose of adjuvant treatment.

Of the patients who received single agent intravenous nivolumab as adjuvant treatment, 22% experienced serious adverse reactions; the most frequent serious adverse reaction was pneumonitis/ILD (2.8%). One fatal adverse reaction due to COVID-19 occurred. Permanent discontinuation of adjuvant intravenous nivolumab due to an adverse reaction occurred in 14% of patients; the most frequent (≥1%) adverse reactions that led to permanent discontinuation of adjuvant intravenous nivolumab were pneumonitis (4.2%) and diarrhea (1.4%).

Second-line Treatment of Metastatic NSCLC

CHECKMATE-017 and CHECKMATE-057

The safety of intravenous nivolumab was evaluated in CHECKMATE-017, a randomized open-label, multicenter trial in patients with metastatic squamous NSCLC and progression on or after one prior platinum doublet-based chemotherapy regimen and in CHECKMATE-057, a randomized, open-label, multicenter trial in patients with metastatic non-squamous NSCLC and progression on or after one prior platinum doublet-based chemotherapy regimen [see Clinical Studies (14.6)]. These trials excluded patients with active autoimmune disease, medical conditions requiring systemic immunosuppression, or with symptomatic interstitial lung disease. Patients received intravenous nivolumab 3 mg/kg over 60 minutes by intravenous infusion every 2 weeks or docetaxel 75 mg/m^2 intravenously every 3 weeks. The median duration of therapy in intravenous nivolumab-treated patients in CHECKMATE-017 was 3.3 months (range: 1 day to 21.7+ months) and in CHECKMATE-057 was 2.6 months (range: 0 to 24.0+ months). In CHECKMATE-017, 36% of patients received intravenous nivolumab for at least 6 months and 18% of patients received intravenous nivolumab for at least 1 year and in CHECKMATE-057, 30% of patients received intravenous nivolumab for >6 months and 20% of patients received intravenous nivolumab for >1 year.

Across both trials, the median age of intravenous nivolumab-treated patients was 61 years (range: 37 to 85); 38% were ≥65 years of age, 61% were male, and 91% were White. Ten percent of patients had brain metastases and ECOG performance status was 0 (26%) or 1 (74%).

In CHECKMATE-057, in the intravenous nivolumab arm, seven deaths were due to infection including one case of Pneumocystis jirovecii pneumonia, four were due to pulmonary embolism, and one death was due to limbic encephalitis. Serious adverse reactions occurred in 46% of patients receiving intravenous nivolumab. Intravenous nivolumab was discontinued in 11% of patients and was delayed in 28% of patients for an adverse reaction.

The most frequent serious adverse reactions reported in ≥2% of patients receiving intravenous nivolumab were pneumonia, pulmonary embolism, dyspnea, pyrexia, pleural effusion, pneumonitis, and respiratory failure. Across both trials, the most common adverse reactions (≥20%) were fatigue, musculoskeletal pain, cough, dyspnea, and decreased appetite.

Tables 25 and 26 summarize selected adverse reactions and laboratory abnormalities, respectively, in CHECKMATE-057.

Table 25: Adverse Reactions Occurring in ≥10% of Intravenous Nivolumab-Treated Patients and at a Higher Incidence than Docetaxel (Between Arm Difference of ≥5% All Grades or ≥2% Grades 3-4) - CHECKMATE-017 and CHECKMATE-057
Adverse Reaction | Intravenous Nivolumab (n=418) |  | Docetaxel (n=397)
Adverse Reaction | All Grades (%) | Grades 3-4 (%) | All Grades (%) | Grades 3-4 (%)
Respiratory, Thoracic and Mediastinal
Cough | 31 | 0.7 | 24 | 0
Metabolism and Nutrition
Decreased appetite | 28 | 1.4 | 23 | 1.5
Skin and Subcutaneous Tissue
Pruritus | 10 | 0.2 | 2 | 0
Toxicity was graded per NCI CTCAE v4.

Other clinically important adverse reactions observed in intravenous nivolumab-treated patients and which occurred at a similar incidence in docetaxel-treated patients and not listed elsewhere in section 6 include: fatigue/asthenia (48% all Grades, 5% Grade 3-4), musculoskeletal pain (33% all Grades), pleural effusion (4.5% all Grades), pulmonary embolism (3.3% all Grades).

Table 26: Laboratory Abnormalities Worsening from Baselinea Occurring in ≥10% of Intravenous Nivolumab-Treated Patients for all NCI CTCAE Grades and at a Higher Incidence than Docetaxel (Between Arm Difference of ≥5% All Grades or ≥2% Grades 3-4) - CHECKMATE-017 and CHECKMATE-057
Laboratory Abnormality | Intravenous Nivolumab |  | Docetaxel
Laboratory Abnormality | All Grades (%) | Grades 3-4 (%) | All Grades (%) | Grades 3-4 (%)
Chemistry
Hyponatremia | 35 | 7 | 34 | 4.9
Increased AST | 27 | 1.9 | 13 | 0.8
Increased alkaline phosphatase | 26 | 0.7 | 18 | 0.8
Increased ALT | 22 | 1.7 | 17 | 0.5
Increased creatinine | 18 | 0 | 12 | 0.5
Increased TSHb | 14 | N/A | 6 | N/A
a Each test incidence is based on the number of patients who had both baseline and at least one on-study laboratory measurement available: intravenous nivolumab group (range: 405 to 417 patients) and docetaxel group (range: 372 to 390 patients), except for TSH: intravenous nivolumab group n=314 and docetaxel group n=297.
b Not graded per NCI CTCAE v4.

Squamous Cell Carcinoma of the Head and Neck

CHECKMATE-141

The safety of intravenous nivolumab was evaluated in CHECKMATE-141, a randomized, active-controlled, open-label, multicenter trial in patients with recurrent or metastatic SCCHN with progression during or within 6 months of receiving prior platinum-based therapy [see Clinical Studies (14.7)]. The trial excluded patients with active autoimmune disease, medical conditions requiring systemic immunosuppression, or recurrent or metastatic carcinoma of the nasopharynx, squamous cell carcinoma of unknown primary histology, salivary gland or non-squamous histologies (e.g., mucosal melanoma). Patients received intravenous nivolumab 3 mg/kg by intravenous infusion over 60 minutes every 2 weeks (n=236) or investigator’s choice of either cetuximab (400 mg/m^2 initial dose intravenously followed by 250 mg/m^2 weekly), or methotrexate (40 to 60 mg/m^2 intravenously weekly), or docetaxel (30 to 40 mg/m^2 intravenously weekly). The median duration of exposure to nivolumab was 1.9 months (range: 1 day to 16.1+ months) in intravenous nivolumab-treated patients. In this trial, 18% of patients received intravenous nivolumab for >6 months and 2.5% of patients received intravenous nivolumab for >1 year.

The median age of all randomized patients was 60 years (range: 28 to 83); 28% of patients in the intravenous nivolumab group were ≥65 years of age and 37% in the comparator group were ≥65 years of age, 83% were male and 83% were White, 12% were Asian, and 4% were Black. Baseline ECOG performance status was 0 (20%) or 1 (78%), 45% of patients received only one prior line of systemic therapy, the remaining 55% of patients had two or more prior lines of therapy, and 90% had prior radiation therapy.

Serious adverse reactions occurred in 49% of patients receiving intravenous nivolumab. Intravenous nivolumab was discontinued in 14% of patients and was delayed in 24% of patients for an adverse reaction. Adverse reactions and laboratory abnormalities occurring in patients with SCCHN were generally similar to those occurring in patients with melanoma and NSCLC.

The most frequent serious adverse reactions reported in ≥2% of patients receiving intravenous nivolumab were pneumonia, dyspnea, respiratory failure, respiratory tract infection, and sepsis. The most common adverse reactions occurring in ≥10% of intravenous nivolumab-treated patients and at a higher incidence than investigator’s choice were cough and dyspnea. The most common laboratory abnormalities occurring in ≥10% of intravenous nivolumab-treated patients and at a higher incidence than investigator’s choice were increased alkaline phosphatase, increased amylase, hypercalcemia, hyperkalemia, and increased TSH.

Urothelial Carcinoma

Adjuvant Treatment of Urothelial Carcinoma (UC)

CHECKMATE-274

The safety of intravenous nivolumab was evaluated in CHECKMATE-274, a randomized, double‑blind, multicenter trial of adjuvant intravenous nivolumab versus placebo in adult patients who had undergone radical resection of UC originating in the bladder or upper urinary tract (renal pelvis or ureter) and were at high risk of recurrence [see Clinical Studies (14.8)]. Patients received intravenous nivolumab 240 mg by intravenous infusion over 30 minutes every 2 weeks (n=351) or placebo (n=348) until recurrence or unacceptable toxicity for a maximum of 1 year. The median duration of intravenous nivolumab treatment was 8.8 months (range: 0 to 12.5).

Serious adverse reactions occurred in 30% of intravenous nivolumab patients. The most frequent serious adverse reaction reported in ≥2% of patients was urinary tract infection. Fatal adverse reactions occurred in 1% of patients; these included events of pneumonitis (0.6%). Intravenous nivolumab was discontinued for adverse reactions in 18% of patients. Intravenous nivolumab was delayed for adverse reaction in 33% of patients.

The most common adverse reactions (reported in ≥20% of patients) were rash, fatigue, diarrhea, pruritus, musculoskeletal pain, and urinary tract infection.

Tables 27 and 28 summarize adverse reactions and laboratory abnormalities, respectively, in CHECKMATE-274.

Table 27: Adverse Reactions Occurring in ≥10% of Patients - CHECKMATE-274
Adverse Reaction | Intravenous Nivolumab; (n=351) |  | Placebo; (n=348)
Adverse Reaction | All Grades (%) | Grades 3-4 (%) | All Grades (%) | Grades 3-4 (%)
Skin and Subcutaneous Tissue
Rasha | 36 | 1.7 | 19 | 0.3
Pruritus | 30 | 0 | 16 | 0
General
Fatigue/Asthenia | 36 | 1.1 | 32 | 0.3
Pyrexia | 10 | 0.3 | 10 | 0.3
Gastrointestinal
Diarrheab | 30 | 2.8 | 27 | 1.7
Nausea | 16 | 0.6 | 13 | 0
Abdominal painc | 15 | 0.9 | 15 | 0.6
Constipation | 13 | 0.3 | 15 | 0.3
Musculoskeletal and Connective Tissue
Musculoskeletal paind | 28 | 0.6 | 24 | 0.9
Arthralgia | 11 | 0.3 | 13 | 0
Infections
Urinary tract infectione | 22 | 6 | 23 | 9
Upper respiratory tract infectionf | 16 | 0.3 | 16 | 0.6
Endocrine
Hyperthyroidism | 11 | 0 | 1.1 | 0
Hypothyroidism | 11 | 0 | 2.3 | 0
Renal and Urinary Disorders
Renal dysfunctiong | 17 | 1.7 | 16 | 0.9
Respiratory, Thoracic and Mediastinal
Coughh | 14 | 0 | 11 | 0
Dyspneai | 11 | 0.3 | 6 | 0.3
Metabolism and Nutrition
Decreased appetite | 13 | 0.9 | 7 | 0.3
Nervous System Disorders
Dizzinessj | 11 | 0.3 | 9 | 0
Hepatobiliary
Hepatitisk | 11 | 4 | 8 | 0.6
Toxicity was graded per NCI CTCAE v4.
a Includes acne, blister, dermatitis, dermatitis acneiform, dermatitis allergic, dermatitis contact, eczema, eczema asteatotic, eczema nummular, erythema, erythema multiforme, lichen sclerosus, lichenoid keratosis, pemphigoid, photosensitivity reaction, pigmentation disorder, psoriasis, rash, rash erythematous, rash macular, rash maculo-papular, rash papular, rash pruritic, rosacea, skin exfoliation, skin lesion, skin reaction, toxic skin eruption, and urticaria.
b Includes colitis, colitis microscopic, diarrhea, duodenitis, enteritis, immune-mediated enterocolitis.
c Includes abdominal pain, abdominal discomfort, abdominal tenderness, lower and upper abdominal pain.
d Includes musculoskeletal pain, back pain, bone pain, musculoskeletal chest pain, musculoskeletal discomfort, myalgia, neck pain, pain in extremity and spinal pain.
e Includes cystitis, escherichia urinary tract infection, pyelonephritis, pyelonephritis acute, pyelonephritis chronic, urethritis, urinary tract infection, urinary tract infection bacterial, urinary tract infection staphylococcal, and urosepsis.
f Includes upper respiratory tract infection, nasopharyngitis, pharyngitis and rhinitis.
g Includes acute kidney injury, autoimmune nephritis, blood creatinine increased, glomerular filtration rate decreased, immune-mediated nephritis, nephritis, renal failure, and renal impairment.
h Includes cough, productive cough, and upper-airway cough syndrome.
i Includes dyspnea and exertional dyspnea.
j Includes dizziness, postural dizziness and vertigo.
k Includes aspartate aminotransferase increased, alanine aminotransferase increased, blood bilirubin increased, cholangitis, drug-induced liver injury, hepatic failure, hepatic function abnormal, hepatitis, hepatocellular injury, hyperbilirubinemia, gamma-glutamyl transferase increased, liver injury, and transaminases increased.

Table 28: Laboratory Abnormalities Worsening from Baselinea Occurring in ≥10% of Patients - CHECKMATE-274
Laboratory Abnormality | Intravenous Nivolumab; (n=351) |  | Placebo; (n=348)
Laboratory Abnormality | All Grades (%) | Grades 3-4 (%) | All Grades (%) | Grades 3-4 (%)
Chemistry
Increased creatinine | 36 | 1.7 | 36 | 2.6
Increased amylase | 34 | 8 | 23 | 3.2
Increased lipase | 33 | 12 | 31 | 10
Hyperkalemia | 32 | 5 | 30 | 6
Increased alkaline phosphatase | 24 | 2.3 | 15 | 0.6
Increased AST | 24 | 3.5 | 16 | 0.9
Increased ALT | 23 | 2.9 | 15 | 0.6
Hyponatremia | 22 | 4.1 | 17 | 1.8
Hypocalcemia | 17 | 1.2 | 11 | 0.9
Hypomagnesemia | 16 | 0 | 9 | 0
Hypercalcemia | 12 | 0.3 | 8 | 0.3
Hematology
Lymphopenia | 33 | 2.9 | 27 | 1.5
Anemia | 30 | 1.4 | 28 | 0.9
Neutropenia | 11 | 0.6 | 10 | 0.3
a Each test incidence is based on the number of patients who had both baseline and at least one on-study laboratory measurement available: intravenous nivolumab group (range: 322 to 348 patients) and placebo group (range: 312 to 341 patients).

First-line Treatment of Unresectable or Metastatic UC

CHECKMATE-901

The safety of intravenous nivolumab was evaluated in CHECKMATE-901, a randomized, open-label trial in cisplatin-eligible patients with unresectable or metastatic UC [see Clinical Studies (14.8)]. Patients received either intravenous nivolumab 360 mg with cisplatin and gemcitabine every 3 weeks for up to 6 cycles followed by single-agent intravenous nivolumab 480 mg every 4 weeks up to 2 years (n=304), or cisplatin and gemcitabine chemotherapy every 3 weeks for up to 6 cycles (n=288). Patients discontinuing cisplatin alone were permitted to switch to carboplatin.

Among patients who received intravenous nivolumab with chemotherapy, the median duration of intravenous nivolumab exposure was 7.4 months (range: 0.03 to 47.9 months). Serious adverse reactions occurred in 48% of patients receiving intravenous nivolumab in combination with chemotherapy. The most frequent serious adverse reactions reported in ≥2% of patients who received intravenous nivolumab with chemotherapy were urinary tract infection (4.9%), acute kidney injury (4.3%), anemia (3%), pulmonary embolism (2.6%), sepsis (2.3%), and platelet count decreased (2.3%). The most common adverse reactions (reported in ≥20% of patients) were nausea, fatigue, musculoskeletal pain, constipation, decreased appetite, rash, vomiting, and peripheral neuropathy.

Fatal adverse reactions occurred in 3.6% of patients who received intravenous nivolumab in combination with chemotherapy; these included sepsis (1%).

Intravenous nivolumab and/or chemotherapy were discontinued in 30% of patients and were delayed in 67% of patients for an adverse reaction.

Tables 29 and 30 summarize the adverse reactions and laboratory abnormalities, respectively, in CHECKMATE-901.

Table 29: Adverse Reactions Occurring in ≥10% of Treated Patients - CHECKMATE-901
Adverse Reaction | Intravenous Nivolumab and Platinum-Doublet Chemotherapy (n=304) |  | Platinum-Doublet Chemotherapy (n=288)
Adverse Reaction | All Grades (%) | Grades 3-4 (%) | All Grades (%) | Grades 3-4 (%)
Gastrointestinal disorders
Nausea | 52 | 0.3 | 53 | 1
Constipation | 30 | 0 | 28 | 0.7
Vomiting | 23 | 1.3 | 19 | 2.1
Diarrheaa | 19 | 2 | 14 | 0
Abdominal painb | 14 | 0.3 | 9 | 0.3
General
Fatiguec | 48 | 3.9 | 43 | 4.2
Edemad | 18 | 0 | 9 | 0.3
Pyrexiae | 14 | 1 | 14 | 0
Musculoskeletal and Connective Tissue
Musculoskeletal painf | 33 | 3 | 21 | 0.3
Metabolism and Nutrition
Decreased appetite | 30 | 1.6 | 19 | 1
Skin and Subcutaneous Tissue
Rashg | 25 | 2.3 | 7 | 0.3
Pruritus | 17 | 0.7 | 3.5 | 0
Nervous System Disorders
Peripheral neuropathyh | 20 | 0.7 | 14 | 0
Headachei | 11 | 0 | 5 | 0
Infections
Urinary tract infectionj | 19 | 8 | 18 | 8
Endocrine disorders
Hypothyroidismk | 17 | 0 | 0.3 | 0
Renal and Urinary Disorders
Renal dysfunctionl | 14 | 6 | 11 | 1.7
Hematuria | 11 | 1 | 7 | 1.4
Investigations
Weight decreased | 11 | 0.3 | 6 | 0
Toxicity was graded per NCI CTCAE v4.
a Includes colitis, immune-mediated enterocolitis.
b Includes upper abdominal pain, lower abdominal pain, abdominal discomfort, epigastric discomfort, gastrointestinal pain, and hepatic pain.
c Includes asthenia.
d Includes peripheral edema, swelling, peripheral swelling, localized edema, swelling, face edema, testicular edema, gravitational edema, and edema genital.
e Includes hyperthermia, body temperature increased and hyperpyrexia.
f Includes back pain, arthralgia, bone pain, arthritis, musculoskeletal chest pain, non-cardiac chest pain, myalgia, neck pain, pain in extremity, and spinal pain.
g Includes maculopapular rash, erythematous rash, macular rash, papular rash, pustular rash, acneiform dermatitis, dermatitis, allergic dermatitis, atopic dermatitis, exfoliative rash, eczema asteatotic, erythema multiforme, palmar-plantar erythrodysesthesia syndrome, eczema, dermatitis exfoliative generalized, and skin exfoliation.
h Includes paresthesia, peripheral sensory neuropathy, hypoesthesia, dysesthesia, neuralgia, hyperesthesia, peripheral motor neuropathy, polyneuropathy.
i Includes occipital neuralgia.
j Includes urosepsis, cystitis, pyelonephritis, pyelonephritis acute, urinary tract infection enterococcal, escherichia urinary tract infection.
k Includes blood stimulating hormone increased.
l Includes acute kidney injury, renal failure, renal impairment, glomerular filtration rate decreased, anuria, azotemia.

Table 30: Selected Laboratory Abnormalities Worsening from Baselinea Occurring in ≥20% of Patients - CHECKMATE-901
Laboratory Abnormality | Intravenous Nivolumab and Platinum-Doublet Chemotherapy (n=304) |  | Platinum-Doublet Chemotherapy (n=288)
Laboratory Abnormality | Grades 1-4 (%) | Grades 3-4 (%) | Grades 1-4 (%) | Grades 3-4 (%)
Hematology
Anemia | 88 | 21 | 80 | 21
Neutropenia | 82 | 35 | 76 | 28
Lymphopenia | 71 | 17 | 56 | 13
Thrombocytopenia | 60 | 13 | 51 | 8
Chemistry
Increased creatinine | 53 | 2.4 | 42 | 1.1
Hypomagnesemia | 48 | 3.8 | 39 | 1.5
Hyponatremia | 43 | 13 | 39 | 8
Hyperglycemia | 41 | 3.9 | 37 | 3.2
Hypocalcemia | 36 | 2.1 | 24 | 1.1
Hyperkalemia | 33 | 3.0 | 32 | 1.1
Increased amylase | 32 | 4.2 | 23 | 3.6
Increased AST | 31 | 2.4 | 17 | 0.7
Increased ALT | 29 | 2.4 | 19 | 0.7
a Each test incidence is based on the number of patients who had both baseline and at least one on-study laboratory measurement available: intravenous nivolumab group (range: 289-301 patients) and chemotherapy group (range: 265-281 patients).

Previously Treated Advanced or Metastatic UC

CHECKMATE-275

The safety of intravenous nivolumab was evaluated in CHECKMATE-275, a single arm trial in which 270 patients with locally advanced or metastatic UC had disease progression during or following platinum-containing chemotherapy or had disease progression within 12 months of neoadjuvant or adjuvant treatment with platinum-containing chemotherapy [see Clinical Studies (14.8)]. Patients received intravenous nivolumab 3 mg/kg by intravenous infusion over 60 minutes every 2 weeks until disease progression or unacceptable toxicity. The median duration of treatment was 3.3 months (range: 0 to 13.4+). Forty-six percent (46%) of patients had a dose interruption for an adverse reaction.

Fourteen patients (5.2%) died from causes other than disease progression. This includes 4 patients (1.5%) who died from pneumonitis or cardiovascular failure which was attributed to treatment with intravenous nivolumab. Serious adverse reactions occurred in 54% of patients. Intravenous nivolumab was discontinued for adverse reactions in 17% of patients.

The most frequent serious adverse reactions reported in ≥2% of patients were urinary tract infection, sepsis, diarrhea, small intestine obstruction, and general physical health deterioration. The most common adverse reactions (reported in ≥20% of patients) were fatigue, musculoskeletal pain, nausea, and decreased appetite.

Tables 31 and 32 summarize adverse reactions and laboratory abnormalities, respectively, in CHECKMATE-275.

Table 31: Adverse Reactions Occurring in ≥10% of Patients - CHECKMATE-275
Adverse Reaction | Intravenous Nivolumab; (n=270)
Adverse Reaction | All Grades (%) | Grades 3-4 (%)
Adverse Reaction | 99 | 51
General
Asthenia/fatigue/malaise | 46 | 7
Pyrexia/tumor associated fever | 17 | 0.4
Edema/peripheral edema/peripheral swelling | 13 | 0.4
Musculoskeletal and Connective Tissue
Musculoskeletal paina | 30 | 2.6
Arthralgia | 10 | 0.7
Metabolism and Nutrition
Decreased appetite | 22 | 2.2
Gastrointestinal
Nausea | 22 | 0.7
Diarrhea | 17 | 2.6
Constipation | 16 | 0.4
Abdominal painb | 13 | 1.5
Vomiting | 12 | 1.9
Respiratory, Thoracic and Mediastinal
Cough/productive cough | 18 | 0
Dyspnea/exertional dyspnea | 14 | 3.3
Infections
Urinary tract infection/escherichia/fungal urinary tract infection | 17 | 7
Skin and Subcutaneous Tissue
Rashc | 16 | 1.5
Pruritus | 12 | 0
Endocrine
Thyroid disordersd | 15 | 0
Toxicity was graded per NCI CTCAE v4.
a Includes back pain, bone pain, musculoskeletal chest pain, musculoskeletal discomfort, myalgia, neck pain, pain in extremity and spinal pain.
b Includes abdominal discomfort, lower and upper abdominal pain.
c Includes dermatitis, dermatitis acneiform, dermatitis bullous, and rash described as generalized, macular, maculopapular, or pruritic.
d Includes autoimmune thyroiditis, blood TSH decrease, blood TSH increase, hyperthyroidism, hypothyroidism, thyroiditis, thyroxine decreased, thyroxine free increased, thyroxine increased, tri-iodothyronine free increased, tri-iodothyronine increased.

Table 32: Laboratory Abnormalities Worsening from Baseline Occurring in ≥10% of Patients - CHECKMATE-275
Laboratory Abnormality | Intravenous Nivolumaba
Laboratory Abnormality | All Grades (%) | Grades 3-4 (%)
Chemistry
Hyperglycemia | 42 | 2.4
Hyponatremia | 41 | 11
Increased creatinine | 39 | 2
Increased alkaline phosphatase | 33 | 5.5
Hypocalcemia | 26 | 0.8
Increased AST | 24 | 3.5
Increased lipase | 20 | 7
Hyperkalemia | 19 | 1.2
Increased ALT | 18 | 1.2
Increased amylase | 18 | 4.4
Hypomagnesemia | 16 | 0
Hematology
Lymphopenia | 42 | 9
Anemia | 40 | 7
Thrombocytopenia | 15 | 2.4
Leukopenia | 11 | 0
a Each test incidence is based on the number of patients who had both baseline and at least one on-study laboratory measurement available: range: 84 to 256 patients.

MSI-H or dMMR Metastatic Colorectal Cancer

First-line Treatment of MSI-H or dMMR Metastatic Colorectal Cancer (mCRC)

CHECKMATE-8HW

The safety of intravenous nivolumab in combination with ipilimumab, or as a single agent, was evaluated in CHECKMATE-8HW, a randomized, open-label, three arm trial in immunotherapy naïve patients with MSI-H or dMMR mCRC [see Clinical Studies (14.11)]. Patients received one of the following:

- Intravenous nivolumab 240 mg every 3 weeks and ipilimumab 1 mg/kg every 3 weeks for a maximum of 4 doses, then intravenous nivolumab 480 mg every 4 weeks
- Intravenous nivolumab 240 mg every 2 weeks for 6 doses, then intravenous nivolumab 480 mg every 4 weeks
- Investigator’s choice chemotherapy: mFOLFOX or FOLFIRI [see Clinical Studies (14.11)]

In the intravenous nivolumab and ipilimumab arm, the median duration of exposure to intravenous nivolumab was 20.5 months (range: 0 to 35.9 months), 70% patients were exposed for >6 months and 63% were exposed for >1 year. In the intravenous nivolumab arm, the median duration of exposure to intravenous nivolumab was 16.4 months (range: 0 to 36 months), 64% patients were exposed for >6 months and 54% were exposed for >1 year.

Serious adverse reactions occurred in 46% of patients receiving intravenous nivolumab in combination with ipilimumab, and 39% of patients receiving intravenous nivolumab alone. The most frequent serious adverse reactions reported in ≥1% of patients who received intravenous nivolumab with ipilimumab were adrenal insufficiency (2.8%), hypophysitis (2.8%), diarrhea (2.0%), abdominal pain (2.0%), small intestinal obstruction (2.0%), pneumonia (1.7%), acute kidney injury (1.4%), immune mediated enterocolitis (1.4%), pneumonitis (1.4%), colitis (1.1%), large intestinal obstruction (1.1%), and urinary tract infection (1.1%). The most frequent serious adverse reactions reported in >1% of patients who received intravenous nivolumab, as a single agent, were intestinal obstruction (2.3%), acute kidney injury (1.7%), COVID-19 (1.7%), abdominal pain (1.4%), diarrhea (1.4%), ileus (1.4%), subileus (1.4%), pulmonary embolism (1.4%), adrenal insufficiency (1.1%) and pneumonia (1.1%).

Fatal adverse reactions occurred in 2 (0.6%) patients who received intravenous nivolumab in combination with ipilimumab; these included myocarditis, and pneumonitis (1 each). Fatal adverse reactions occurring in 3 (0.9%) patients who received intravenous nivolumab as a single agent; these included pneumonitis (n=2) and myasthenia gravis.

Intravenous nivolumab and/or ipilimumab were permanently discontinued in 19% of patients receiving the combination. The most frequent adverse reactions (>1%) leading to permanent discontinuation were adrenal insufficiency (1.4%), immune mediated enterocolitis (1.1%), and pneumonitis (1.1%). Intravenous nivolumab was permanently discontinued in 13% of patients receiving single agent intravenous nivolumab. Adverse reactions leading to the delay of intravenous nivolumab and/or ipilimumab occurred in 48% of patients receiving the combination; single agent intravenous nivolumab was delayed in 37% of patients due to adverse reactions.

The most common adverse reactions reported in ≥20% of patients treated with intravenous nivolumab in combination with ipilimumab were fatigue, diarrhea, pruritus, abdominal pain, musculoskeletal pain, and nausea. The most common adverse reactions reported in ≥20% of patients treated with intravenous nivolumab as a single agent, were fatigue, diarrhea, abdominal pain, pruritus, and musculoskeletal pain.

Tables 33 and 34 summarize selected adverse reactions and selected laboratory abnormalities for intravenous nivolumab in combination with ipilimumab and the single agent intravenous nivolumab arms respectively, in CHECKMATE-8HW.

Table 33: Adverse Reactionsa in ≥10% in Patients with a Difference Between Arms of >5% for All Grades in CHECKMATE-8HW
Adverse Reaction | Intravenous Nivolumab and Ipilimumab (n=352) |  | Intravenous Nivolumab (n=351)
Adverse Reaction | All Grades (%) | Grades 3 or 4 (%) | All Grades (%) | Grades 3 or 4 (%)
Gastrointestinal
Diarrheaa | 35 | 4.5 | 30 | 3.4
Skin and Subcutaneous Tissue
Pruritus | 30 | 0 | 23 | 0
Musculoskeletal and Connective Tissue
Arthralgia | 20 | 0.6 | 15 | 0.6
Endocrine
Hypothyroidism | 18 | 0.6 | 10 | 0
Hyperthyroidism | 12 | 0 | 5 | 0
Toxicity was graded per NCI CTCAE v5.
a Includes colitis, diarrhea, enterocolitis, immune mediated enterocolitis

Table 34: Laboratory Values Worsening from Baselinea in ≥10% of Patients and a Difference Between Arms of >5% for All Grades - CHECKMATE-8HW
Laboratory Abnormalitya | Intravenous Nivolumab and Ipilimumab (n=352) |  | Intravenous Nivolumab (n=351)
Laboratory Abnormalitya | All Grades (%) | Grades 3 or 4 (%) | All Grades (%) | Grades 3 or 4 (%)
Chemistry
Lipase increased | 44 | 10 | 32 | 11
Amylase increased | 41 | 4.6 | 33 | 5
ALT increased | 39 | 3.5 | 32 | 1.4
AST increased | 38 | 3.2 | 29 | 1.4
Sodium decreased | 36 | 3.2 | 30 | 2.3
Creatinine increased | 32 | 2 | 25 | 1.4
Potassium increased | 29 | 1.2 | 35 | 0.9
Glucose decreased | 17 | 0 | 12 | 0
Hematology
Lymphocytes decreased | 30 | 5 | 37 | 4
Neutrophils decreased | 21 | 1.7 | 12 | 0.6
a Each test incidence is based on the number of patients who had both baseline and at least one on-study laboratory measurement available: OPDIVO and ipilimumab group (range: 108 to 343 patients) or nivolumab group (range: 102 to 348 patients).

MSI-H or dMMR mCRC After Progression Following Treatment with a Fluoropyrimidine, Oxaliplatin, and Irinotecan

CHECKMATE-142

The safety of intravenous nivolumab administered as a single agent or in combination with ipilimumab was evaluated in CHECKMATE‑142, a multicenter, non-randomized, multiple parallel-cohort, open-label trial [see Clinical Studies (14.9)]. In CHECKMATE-142, 74 patients with mCRC received intravenous nivolumab 3 mg/kg by intravenous infusion over 60 minutes every 2 weeks until disease progression or until intolerable toxicity and 119 patients with mCRC received intravenous nivolumab 3 mg/kg and ipilimumab 1 mg/kg every 3 weeks for 4 doses, then intravenous nivolumab 3 mg/kg every 2 weeks until disease progression or until unacceptable toxicity.

In the intravenous nivolumab with ipilimumab cohort, serious adverse reactions occurred in 47% of patients. Treatment was discontinued in 13% of patients and delayed in 45% of patients for an adverse reaction. The most frequent serious adverse reactions reported in ≥2% of patients were colitis/diarrhea, hepatic events, abdominal pain, acute kidney injury, pyrexia, and dehydration. The most common adverse reactions (reported in ≥20% of patients) were fatigue, diarrhea, pyrexia, musculoskeletal pain, abdominal pain, pruritus, nausea, rash, decreased appetite, and vomiting.

Tables 35 and 36 summarize adverse reactions and laboratory abnormalities, respectively, in CHECKMATE-142. Based on the design of CHECKMATE-142, the data below cannot be used to identify statistically significant differences between the two cohorts summarized below for any adverse reaction.

Table 35: Adverse Reactions Occurring in ≥10% of Patients - CHECKMATE-142
Adverse Reaction | Intravenous Nivolumab (n=74) |  | Intravenous Nivolumab and Ipilimumab (n=119)
Adverse Reaction | All Grades (%) | Grades 3-4 (%) | All Grades (%) | Grades 3-4 (%)
General
Fatiguea | 54 | 5 | 49 | 6
Pyrexia | 24 | 0 | 36 | 0
Edemab | 12 | 0 | 7 | 0
Gastrointestinal
Diarrhea | 43 | 2.7 | 45 | 3.4
Abdominal painc | 34 | 2.7 | 30 | 5
Nausea | 34 | 1.4 | 26 | 0.8
Vomiting | 28 | 4.1 | 20 | 1.7
Constipation | 20 | 0 | 15 | 0
Musculoskeletal and Connective Tissue
Musculoskeletal paind | 28 | 1.4 | 36 | 3.4
Arthralgia | 19 | 0 | 14 | 0.8
Respiratory, Thoracic and Mediastinal
Cough | 26 | 0 | 19 | 0.8
Dyspnea | 8 | 1 | 13 | 1.7
Skin and Subcutaneous Tissue
Rashe | 23 | 1.4 | 25 | 4.2
Pruritus | 19 | 0 | 28 | 1.7
Dry Skin | 7 | 0 | 11 | 0
Infections
Upper respiratory tract infectionf | 20 | 0 | 9 | 0
Endocrine
Hyperglycemia | 19 | 2.7 | 6 | 1
Hypothyroidism | 5 | 0 | 14 | 0.8
Hyperthyroidism | 4 | 0 | 12 | 0
Nervous System
Headache | 16 | 0 | 17 | 1.7
Dizziness | 14 | 0 | 11 | 0
Metabolism and Nutrition
Decreased appetite | 14 | 1.4 | 20 | 1.7
Psychiatric
Insomnia | 9 | 0 | 13 | 0.8
Investigations
Weight decreased | 8 | 0 | 10 | 0
Toxicity was graded per NCI CTCAE v4.
a Includes asthenia.
b Includes peripheral edema and peripheral swelling.
c Includes upper abdominal pain, lower abdominal pain, and abdominal discomfort.
d Includes back pain, pain in extremity, myalgia, neck pain, and bone pain.
e Includes dermatitis, dermatitis acneiform, and rash described as maculo-papular, erythematous, and generalized.
f Includes nasopharyngitis and rhinitis.

Clinically important adverse reactions reported in <10% of patients receiving intravenous nivolumab with ipilimumab were encephalitis (0.8%), necrotizing myositis (0.8%), and uveitis (0.8%).

Table 36: Laboratory Abnormalities Worsening from Baselinea Occurring in ≥10% of Patients - CHECKMATE-142
Laboratory Abnormality | Intravenous Nivolumab (n=74) |  | Intravenous Nivolumab and Ipilimumab (n=119)
Laboratory Abnormality | All Grades (%) | Grades 3-4 (%) | All Grades (%) | Grades 3-4 (%)
Hematology
Anemia | 50 | 7 | 42 | 9
Lymphopenia | 36 | 7 | 25 | 6
Neutropenia | 20 | 4.3 | 18 | 0
Thrombocytopenia | 16 | 1.4 | 26 | 0.9
Chemistry
Increased alkaline phosphatase | 37 | 2.8 | 28 | 5
Increased lipase | 33 | 19 | 39 | 12
Increased ALT | 32 | 2.8 | 33 | 12
Increased AST | 31 | 1.4 | 40 | 12
Hyponatremia | 27 | 4.3 | 26 | 5
Hypocalcemia | 19 | 0 | 16 | 0
Hypomagnesemia | 17 | 0 | 18 | 0
Increased amylase | 16 | 4.8 | 36 | 3.4
Increased bilirubin | 14 | 4.2 | 21 | 5
Hypokalemia | 14 | 0 | 15 | 1.8
Increased creatinine | 12 | 0 | 25 | 3.6
Hyperkalemia | 11 | 0 | 23 | 0.9
a Each test incidence is based on the number of patients who had both baseline and at least one on-study laboratory measurement available. Number of evaluable patients ranges from 62 to 71 for the intravenous nivolumab cohort and from 87 to 114 for the intravenous nivolumab and ipilimumab cohort.

Hepatocellular Carcinoma

Unresectable or Metastatic Hepatocellular Carcinoma (HCC)

CHECKMATE-9DW

The safety of intravenous nivolumab 1 mg/kg in combination with ipilimumab was evaluated in CHECKMATE-9DW, a randomized, open-label trial in adult patients with unresectable or metastatic HCC [see Clinical Studies (14.10)]. Patients received intravenous nivolumab 1 mg/kg in combination with ipilimumab (n=332) or investigator’s choice of lenvatinib (n=275) or sorafenib (n=50) at the following dosage:

- Intravenous nivolumab 1 mg/kg administered intravenously over 30 minutes in combination with ipilimumab 3 mg/kg administered intravenously over 30 minutes every 3 weeks, for a maximum of 4 doses, followed by single-agent intravenous nivolumab at 480 mg administered intravenously over 30 minutes every 4 weeks, or
- Investigator’s choice:
  - Lenvatinib 8 mg orally daily (if body weight <60 kg) or 12 mg orally daily (if body weight ≥60 kg), or
  - Sorafenib 400 mg orally twice daily

In the intravenous nivolumab 1 mg/kg and ipilimumab arm, the median duration of exposure to intravenous nivolumab 1 mg/kg was 4.7 months (range: <0.1 to 24.4 months), 45% were exposed for >6 months and 30% were exposed for >1 year.

Serious adverse reactions occurred in 53% of patients treated with intravenous nivolumab 1 mg/kg in combination with ipilimumab. The most frequent non liver-related serious adverse reactions reported in ≥2% of patients who received intravenous nivolumab 1 mg/kg in combination with ipilimumab were diarrhea/colitis (4.5%), gastrointestinal hemorrhage (3%), and rash (2.4%).

Liver-related serious adverse reactions occurred in 17% of patients treated with intravenous nivolumab 1 mg/kg in combination with ipilimumab, including Grade 3-4 events in 16% of patients. The most frequently reported all grade liver-related serious adverse reactions occurring in ≥ 1% of patients who received intravenous nivolumab 1 mg/kg in combination with ipilimumab were immune-mediated hepatitis (3%), increased AST/ALT (3%), hepatic failure (2.4%), ascites (2.4%), and hepatotoxicity (1.2%).

Fatal adverse reactions occurred in 12 (3.6%) patients who received intravenous nivolumab 1 mg/kg in combination with ipilimumab; these included 4 (1.2%) patients who died due to immune-mediated or autoimmune hepatitis and 4 (1.2%) patients who died of hepatic failure.

Permanent discontinuations of intravenous nivolumab 1 mg/kg due to an adverse reaction occurred in 27% of patients. Adverse reactions leading to permanent discontinuation of intravenous nivolumab 1 mg/kg in >1% of patients included immune-mediated hepatitis (1.8%), diarrhea/colitis (1.8%), hepatic failure (1.2%).

Dosage interruptions of intravenous nivolumab 1 mg/kg due to an adverse reaction occurred in 62% of patients. Adverse reactions which required dosage interruption in >5% of patients included increased AST (13%), increased ALT (11%), and diarrhea/colitis (8%).

The most common (>20%) adverse reactions were rash, pruritus, fatigue, and diarrhea.

Tables 37 and 38 summarize the adverse reactions and laboratory abnormalities, respectively, in CHECKMATE-9DW.

Table 37: Adverse Reactions Occurring in ≥10% of Intravenous Nivolumab 1 mg/kg in combination with Ipilimumab-Treated Patients - CHECKMATE-9DW
Adverse Reaction | Intravenous Nivolumab 1 mg/kg and Ipilimumab; (n=332) |  | Lenvatinib or Sorafenib; (n=325)
Adverse Reaction | All Grades (%) | Grades 3-4 (%) | All Grades (%) | Grades 3-4 (%)
Skin and Subcutaneous Tissue
Rasha | 36 | 3.6 | 15 | 1.2
Pruritus | 34 | 1.5 | 7 | 0.3
General
Fatiguea | 33 | 2.4 | 39 | 4
Pyrexiaa | 15 | 0.6 | 9 | 1.5
Edemaa | 13 | 1.2 | 13 | 1.5
Gastrointestinal
Diarrheaa | 25 | 6 | 39 | 3.4
Abdominal paina | 14 | 1.2 | 27 | 2.5
Nausea | 10 | 0.3 | 16 | 0.9
Musculoskeletal and Connective Tissue
Musculoskeletal paina | 17 | 0.6 | 23 | 0.3
Arthralgia | 12 | 0.3 | 13 | 0.6
Metabolism and Nutrition
Decreased appetite | 16 | 1.2 | 28 | 1.8
Endocrine
Hypothyroidisma | 14 | 0 | 27 | 0
Hyperthyroidism | 11 | 0.6 | 1.5 | 0
Respiratory, Thoracic and Mediastinal
Cougha | 13 | 0 | 8 | 0
Toxicity was graded per NCI CTCAE v5
a Represents a composite of multiple related terms.

Clinically important adverse reactions reported in <10% of patients who received intravenous nivolumab 1 mg/kg with ipilimumab were hyperglycemia (8%), adrenal insufficiency (4.2%), pneumonitis (2.7%), and pancreatitis (2.4%).

Table 38: Laboratory Values Worsening from Baselinea Occurring in ≥20% of intravenous Nivolumab 1 mg/kg in combination with Ipilimumab-Treated Patients - CHECKMATE-9DW
Laboratory Abnormality | Intravenous Nivolumab 1 mg/kg and Ipilimumab; (n=332) |  | Lenvatinib or Sorafenib; (n=325)
Laboratory Abnormality | Grades 1-4 (%) | Grades 3-4 (%) | Grades 1-4 (%) | Grades 3-4 (%)
Chemistry
Increased AST | 62 | 29 | 51 | 14
Increased ALT | 61 | 17 | 46 | 9
Increased lipase | 58 | 16 | 39 | 5
Decreased albumin | 48 | 0.9 | 57 | 0.6
Hyponatremia | 45 | 6 | 42 | 3.8
Hyperglycemia | 44 | 15 | 32 | 2.1
Increased bilirubin | 44 | 10 | 44 | 8
Increased amylase | 41 | 6 | 26 | 1
Increased alkaline phosphatase | 36 | 1.2 | 38 | 5
Hypocalcemia | 29 | 0.9 | 46 | 0
Increased creatinine | 26 | 2.4 | 23 | 0.6
Hypokalemia | 21 | 2.1 | 20 | 2.6
Hematology
Anemia | 44 | 5 | 40 | 3.8
Lymphopenia | 40 | 6.1 | 40 | 8
Thrombocytopenia | 27 | 4 | 44 | 4.8
Neutropenia | 24 | 4 | 32 | 3.5
a Each test incidence is based on the number of patients who had both baseline and at least one on-study laboratory measurement available: intravenous nivolumab 1 mg/kg and ipilimumab group (range: 168 to 331 patients) and lenvatinib or sorafenib group (range: 145 to 315 patients).

Previously Treated Hepatocellular Carcinoma

CHECKMATE-040

The safety of intravenous nivolumab 1 mg/kg in combination with ipilimumab 3 mg/kg was evaluated in a subgroup comprising 49 patients with HCC and Child-Pugh Class A cirrhosis enrolled in Cohort 4 of CHECKMATE-040, a multicenter, multiple-cohort, open-label trial [see Clinical Studies (14.10)] who progressed on or were intolerant to sorafenib. Intravenous nivolumab and ipilimumab were administered every 3 weeks for 4 doses, followed by single-agent intravenous nivolumab 240 mg every 2 weeks until disease progression or unacceptable toxicity. During the intravenous nivolumab and ipilimumab combination period, 33 of 49 (67%) patients received all 4 planned doses of intravenous nivolumab and ipilimumab. During the entire treatment period, the median duration of exposure to intravenous nivolumab was 5.1 months (range: 0 to 35+ months) and to ipilimumab was 2.1 months (range: 0 to 4.5 months). Forty-seven percent of patients were exposed to treatment for >6 months, and 35% of patients were exposed to treatment for >1 year. Serious adverse reactions occurred in 59% of patients. Treatment was discontinued in 29% of patients and delayed in 65% of patients for an adverse reaction.

The most frequent serious adverse reactions (reported in ≥4% of patients) were pyrexia, diarrhea, anemia, increased AST, adrenal insufficiency, ascites, esophageal varices hemorrhage, hyponatremia, increased blood bilirubin, and pneumonitis.

Tables 39 and 40 summarize the adverse reactions and laboratory abnormalities, respectively, in CHECKMATE-040.

Table 39: Adverse Reactions Occurring in ≥10% of Patients Receiving Intravenous Nivolumab in Combination with Ipilimumab in Cohort 4 of CHECKMATE-040
Adverse Reaction | Intravenous Nivolumab and Ipilimumab; (n=49)
Adverse Reaction | All Grades (%) | Grades 3-4 (%)
Skin and Subcutaneous Tissue
Rash | 53 | 8
Pruritus | 53 | 4
Musculoskeletal and Connective Tissue
Musculoskeletal pain | 41 | 2
Arthralgia | 10 | 0
Gastrointestinal
Diarrhea | 39 | 4
Abdominal pain | 22 | 6
Nausea | 20 | 0
Ascites | 14 | 6
Constipation | 14 | 0
Dry mouth | 12 | 0
Dyspepsia | 12 | 2
Vomiting | 12 | 2
Stomatitis | 10 | 0
Respiratory, Thoracic and Mediastinal
Cough | 37 | 0
Dyspnea | 14 | 0
Pneumonitis | 10 | 2
Metabolism and Nutrition
Decreased appetite | 35 | 2
General
Fatigue | 27 | 2
Pyrexia | 27 | 0
Malaise | 18 | 2
Edema | 16 | 2
Influenza-like illness | 14 | 0
Chills | 10 | 0
Nervous System
Headache | 22 | 0
Dizziness | 20 | 0
Endocrine
Hypothyroidism | 20 | 0
Adrenal insufficiency | 18 | 4
Investigations
Weight decreased | 20 | 0
Psychiatric
Insomnia | 18 | 0
Blood and Lymphatic System
Anemia | 10 | 4
Infections
Influenza | 10 | 2
Vascular
Hypotension | 10 | 0

Clinically important adverse reactions reported in <10% of patients who received intravenous nivolumab with ipilimumab were hyperglycemia (8%), colitis (4%), and increased blood creatine phosphokinase (2%).

Table 40: Laboratory Abnormalities Worsening from Baseline Occurring in ≥10% of Patients Receiving Intravenous Nivolumab in Combination with Ipilimumab in Cohort 4 of CHECKMATE-040
Laboratory Abnormality | Intravenous Nivolumab and Ipilimumab; (n=47)
Laboratory Abnormality | All Grades (%) | Grades 3-4 (%)
Hematology
Lymphopenia | 53 | 13
Anemia | 43 | 4.3
Neutropenia | 43 | 9
Leukopenia | 40 | 2.1
Thrombocytopenia | 34 | 4.3
Chemistry
Increased AST | 66 | 40
Increased ALT | 66 | 21
Increased bilirubin | 55 | 11
Increased lipase | 51 | 26
Hyponatremia | 49 | 32
Hypocalcemia | 47 | 0
Increased alkaline phosphatase | 40 | 4.3
Increased amylase | 38 | 15
Hypokalemia | 26 | 2.1
Hyperkalemia | 23 | 4.3
Increased creatinine | 21 | 0
Hypomagnesemia | 11 | 0

In patients who received intravenous nivolumab with ipilimumab, virologic breakthrough occurred in 4 of 28 (14%) patients and 2 of 4 (50%) patients with active HBV or HCV at baseline, respectively. HBV virologic breakthrough was defined as at least a 1 log increase in HBV DNA for those patients with detectable HBV DNA at baseline. HCV virologic breakthrough was defined as a 1 log increase in HCV RNA from baseline.

Esophageal Cancer

Adjuvant Treatment of Resected Esophageal or Gastroesophageal Junction Cancer

CHECKMATE-577

The safety of intravenous nivolumab was evaluated in CHECKMATE-577, a randomized, placebo-controlled, double-blinded, multicenter trial in 792 treated patients with completely resected (negative margins) esophageal or gastroesophageal junction cancer who had residual pathologic disease following chemoradiotherapy (CRT) [see Clinical Studies (14.11)]. The trial excluded patients who did not receive concurrent CRT prior to surgery, had stage IV resectable disease, autoimmune disease, or any condition requiring systemic treatment with either corticosteroids (>10 mg daily prednisone or equivalent) or other immunosuppressive medications. Patients received either intravenous nivolumab 240 mg or placebo by intravenous infusion over 30 minutes every 2 weeks for 16 weeks followed by 480 mg or placebo by intravenous infusion over 30 minutes every 4 weeks beginning at week 17. Patients were treated until disease recurrence, unacceptable toxicity, or for up to 1‑year total duration. The median duration of exposure was 10.1 months (range: <0.1 to 14 months) in intravenous nivolumab-treated patients and 9 months (range: <0.1 to 15 months) in placebo-treated patients. Among patients who received intravenous nivolumab, 61% were exposed for >6 months and 54% were exposed for >9 months.

Serious adverse reactions occurred in 33% of patients receiving intravenous nivolumab. A serious adverse reaction reported in ≥2% of patients who received intravenous nivolumab was pneumonitis. A fatal adverse reaction of myocardial infarction occurred in one patient who received intravenous nivolumab.

Intravenous nivolumab was discontinued in 12% of patients and was delayed in 28% of patients for an adverse reaction.

Tables 41 and 42 summarize the adverse reactions and laboratory abnormalities, respectively, in CHECKMATE-577.

Table 41: Adverse Reactions Occurring in ≥10% of Patients Receiving Intravenous Nivolumab - CHECKMATE-577
Adverse Reaction | Intravenous Nivolumab; (n=532) |  | Placebo; (n=260)
Adverse Reaction | All Grades (%) | Grades 3-4 (%) | All Grades (%) | Grades 3-4 (%)
Adverse Reaction | 96 | 34 | 93 | 32
Gastrointestinal
Diarrhea | 29 | 0.9 | 29 | 0.8
Nausea | 23 | 0.8 | 21 | 0
Abdominal Paina | 17 | 0.8 | 20 | 1.5
Vomiting | 15 | 0.6 | 16 | 1.2
Dysphagia | 13 | 0.8 | 17 | 3.5
Dyspepsiab | 12 | 0.2 | 16 | 0.4
Constipation | 11 | 0 | 12 | 0
General
Fatiguec | 34 | 1.3 | 29 | 1.5
Respiratory, Thoracic and Mediastinal
Coughd | 20 | 0.2 | 21 | 0.4
Dyspneae | 12 | 0.8 | 12 | 0.4
Skin and Subcutaneous Tissue
Rashf | 21 | 0.9 | 10 | 0.4
Pruritus | 13 | 0.4 | 6 | 0
Investigations
Weight decreased | 13 | 0.4 | 9 | 0
Musculoskeletal and Connective Tissue
Musculoskeletal paing | 21 | 0.6 | 20 | 0.8
Arthralgia | 10 | 0.2 | 8 | 0
Metabolism and Nutrition
Decreased appetite | 15 | 0.9 | 10 | 0.8
Endocrine
Hypothyroidism | 11 | 0 | 1.5 | 0
a Includes upper abdominal pain, lower abdominal pain, and abdominal discomfort.
b Includes gastroesophageal reflux.
c Includes asthenia.
d Includes productive cough.
e Includes dyspnea exertional.
f Includes rash pustular, dermatitis, dermatitis acneiform, dermatitis allergic, dermatitis bullous, exfoliative rash, rash erythematous, rash macular, rash maculo-papular, rash papular, rash pruritic.
g Includes back pain, bone pain, musculoskeletal chest pain, musculoskeletal discomfort, myalgia, myalgia intercostal, neck pain, pain in extremity, spinal pain.

Table 42: Laboratory Abnormalities Worsening from Baselinea Occurring in ≥10% of Patients - CHECKMATE-577
Laboratory Abnormality | Intravenous Nivolumab; (n=532) |  | Placebo; (n=260)
Laboratory Abnormality | All Grades (%) | Grades 3-4 (%) | All Grades (%) | Grades 3-4 (%)
Chemistry
Increased AST | 27 | 2.1 | 22 | 0.8
Increased alkaline phosphatase | 25 | 0.8 | 18 | 0.8
Increased albumin | 21 | 0.2 | 18 | 0
Increased ALT | 20 | 1.9 | 16 | 1.2
Increased amylase | 20 | 3.9 | 13 | 1.3
Hyponatremia | 19 | 1.7 | 12 | 1.2
Hyperkalemia | 17 | 0.8 | 15 | 1.6
Hypokalemia | 12 | 1 | 11 | 1.2
Transaminases increasedb | 11 | 1.5 | 6 | 1.2
Hematology
Lymphopenia | 44 | 17 | 35 | 12
Anemia | 27 | 0.8 | 21 | 0.4
Neutropenia | 24 | 1.5 | 23 | 0.4
a Each test incidence is based on the number of patients who had both baseline and at least one on-study laboratory measurement available: intravenous nivolumab group (range: 163 to 526 patients) and Placebo group (range: 86 to 256 patients).
b Includes alanine aminotransferase increased, aspartate aminotransferase increased.

First-line Treatment of Unresectable Advanced or Metastatic ESCC

CHECKMATE‑648

The safety of intravenous nivolumab in combination with chemotherapy or in combination with ipilimumab was evaluated in CHECKMATE‑648, a randomized, active-controlled, multicenter, open-label trial in patients with previously untreated unresectable advanced, recurrent or metastatic ESCC [see Clinical Studies (14.11)]. Patients received one of the following treatments:

- intravenous nivolumab 240 mg on days 1 and 15, 5-FU (fluorouracil) 800 mg/m^2/day intravenously on days 1 through 5 (for 5 days), and cisplatin 80 mg/m^2 intravenously on day 1 (of a 4‑week cycle).
- intravenous nivolumab 3 mg/kg every 2 weeks in combination with ipilimumab 1 mg/kg every 6 weeks.
- 5-FU (fluorouracil) 800 mg/m^2/day intravenously on days 1 through 5 (for 5 days), and cisplatin 80 mg/m^2 intravenously on day 1 (of a 4-week cycle).

Among patients who received intravenous nivolumab with chemotherapy, the median duration of exposure was 5.7 months (range: 0.1 to 30.6 months). Among patients who received intravenous nivolumab and ipilimumab, the median duration of exposure was 2.8 months (range: 0 to 24 months).

Serious adverse reactions occurred in 62% of patients receiving intravenous nivolumab in combination with chemotherapy and in 69% of patients receiving intravenous nivolumab in combination with ipilimumab. The most frequent serious adverse reactions reported in ≥2% of patients who received intravenous nivolumab with chemotherapy were pneumonia (11%), dysphagia (7%), esophageal stenosis (2.9%), acute kidney injury (2.9%), and pyrexia (2.3%). The most frequent serious adverse reactions reported in ≥2% of patients who received intravenous nivolumab with ipilimumab were pneumonia (10%), pyrexia (4.3%), pneumonitis (4%), aspiration pneumonia (3.7%), dysphagia (3.7%), hepatic function abnormal (2.8%), decreased appetite (2.8%), adrenal insufficiency (2.5%), and dehydration (2.5%).

Fatal adverse reactions occurred in 5 (1.6%) patients who received intravenous nivolumab in combination with chemotherapy; these included pneumonitis, pneumatosis intestinalis, pneumonia, and acute kidney injury and in 5 (1.6%) patients who received intravenous nivolumab in combination with ipilimumab; these included pneumonitis, interstitial lung disease, pulmonary embolism, and acute respiratory distress syndrome.

Intravenous nivolumab and/or chemotherapy were discontinued in 39% of patients and were delayed in 71% of patients for an adverse reaction. Intravenous nivolumab and/or ipilimumab were discontinued in 23% of patients and were delayed in 46% of patients for an adverse reaction.

The most common adverse reactions reported in ≥20% of patients treated with intravenous nivolumab in combination with chemotherapy were nausea, decreased appetite, fatigue, constipation, stomatitis, diarrhea, and vomiting. The most common adverse reactions reported in ≥20% of patients treated with intravenous nivolumab in combination with ipilimumab were rash, fatigue, pyrexia, nausea, diarrhea, and constipation.

Tables 43 and 44 summarize the adverse reactions and laboratory abnormalities, respectively, in CHECKMATE-648.

Table 43: Adverse Reactions in ≥10% of Patients - CHECKMATE-648
Adverse Reaction | Intravenous Nivolumab with Cisplatin and 5‑FU; (n=310) |  | Intravenous Nivolumab and Ipilimumab; (n=322) |  | Cisplatin and 5-FU; (n=304)
Adverse Reaction | All Grades (%) | Grades 3-4 (%) | All Grades (%) | Grades 3-4 (%) | All Grades (%) | Grades 3‑4 (%)
Gastrointestinal
Nausea | 65 | 4.2 | 22 | 0.6 | 56 | 2.6
Constipation | 44 | 1.0 | 20 | 0.3 | 43 | 1
Stomatitisa | 44 | 9 | 11 | 0.6 | 35 | 3
Diarrhea | 29 | 2.9 | 22 | 1.9 | 20 | 2
Vomiting | 23 | 2.3 | 15 | 1.6 | 19 | 3
Dysphagia | 14 | 7 | 12 | 5 | 12 | 4.9
Abdominal painb | 13 | 1.9 | 10 | 0.9 | 11 | 0.7
Metabolism and Nutrition
Decreased appetite | 51 | 7 | 17 | 4 | 50 | 6
General
Fatiguec | 47 | 3.5 | 28 | 2.5 | 41 | 4.9
Pyrexiad | 19 | 0.3 | 23 | 0.9 | 12 | 0.3
Edemae | 16 | 0 | 7 | 0 | 13 | 0
Nervous System
Peripheral neuropathyf | 18 | 1.3 | 2.8 | 0 | 13 | 1
Psychiatric
Insomnia | 16 | 0 | 8 | 0 | 10 | 0.3
Skin and Subcutaneous Tissue
Rashg | 16 | 0.6 | 31 | 3.1 | 7 | 0
Pruritus | 11 | 0 | 17 | 0.9 | 3.6 | 0
Alopecia | 10 | 0 |  |  | 11 | 0
Respiratory, Thoracic and Mediastinal
Coughh | 16 | 0.3 | 13 | 0.3 | 13 | 0.3
Infections and Infestations
Pneumoniai | 13 | 5 | 14 | 8 | 10 | 2.6
Endocrine
Hypothyroidism | 7 | 0 | 14 | 0 | 0.3 | 0
Investigations
Weight decreased | 12 | 0.6 | 12 | 1.9 | 11 | 1
Musculoskeletal and Connective Tissue
Musculoskeletal painj | 11 | 0.3 | 14 | 0.6 | 8 | 0.3
Toxicity was graded per NCI CTCAE v4.
a Includes aphthous ulcer, mouth ulceration, and mucosal inflammation.
b Includes abdominal discomfort, abdominal pain lower, and abdominal pain upper.
c Includes asthenia and malaise.
d Includes tumor associated fever.
e Includes swelling, generalized edema, edema peripheral, and peripheral swelling.
f Includes hyperesthesia, hypoesthesia, peripheral motor neuropathy, peripheral sensorimotor neuropathy, and peripheral sensory neuropathy.
g Includes dermatitis, dermatitis acneiform, dermatitis allergic, dermatitis bullous, drug eruption, exfoliative rash, rash erythematous, rash follicular, rash macular, rash maculo-papular, rash papular, and rash pruritic.
h Includes productive cough.
i Includes organizing pneumonia, pneumonia bacterial, and pneumonia pseudomonal.
j Includes back pain, bone pain, musculoskeletal chest pain, myalgia, neck pain, pain in extremity, and spinal pain.

Table 44: Laboratory Values Worsening from Baselinea Occurring in ≥10% of Patients - CHECKMATE-648
Laboratory Abnormality | Intravenous Nivolumab with Cisplatin and 5‑FU (n=310) |  | Intravenous Nivolumab and Ipilimumab; (n=322) |  | Cisplatin and 5-FU (n=304)
Laboratory Abnormality | Grades 1-4 (%) | Grades 3-4 (%) | Grades 1-4 (%) | Grades 3-4 (%) | Grades 1-4 (%) | Grades 3-4 (%)
Hematology
Anemia | 81 | 21 | 52 | 7 | 66 | 14
Lymphopenia | 67 | 23 | 50 | 13 | 44 | 8
Neutropenia | 61 | 18 | 13 | 1.3 | 48 | 13
Leukopenia | 53 | 11 |  |  | 39 | 5
Thrombocytopenia | 43 | 3.3 | 12 | 1 | 29 | 2.8
Chemistry
Hyponatremia | 52 | 15 | 45 | 11 | 40 | 8
Hypocalcemia | 43 | 3 | 32 | 0 | 23 | 0.7
Increased creatinine | 41 | 2.3 | 15 | 0.7 | 31 | 0.7
Hypomagnesemia | 35 | 1.7 | 15 | 0 | 25 | 1.8
Hyperglycemia | 34 | 0 | 43 | 4.3 | 36 | 0.8
Hyperkalemia | 33 | 2.3 | 23 | 1.6 | 24 | 0.7
Hypokalemia | 29 | 9 | 19 | 5 | 17 | 6
Increased alkaline phosphatase | 26 | 1.3 | 31 | 3.3 | 15 | 0
Increased AST | 23 | 3.3 | 39 | 6 | 11 | 1.4
Increased ALT | 23 | 2.3 | 33 | 6 | 8 | 0.7
Hypoglycemia | 18 | 0.4 | 15 | 1.2 | 7 | 0
Hypercalcemia | 11 | 2.6 | 15 | 2 | 8 | 0
a Each test incidence is based on the number of patients who had both baseline and at least one on-study laboratory measurement available: intravenous nivolumab with cisplatin and 5-FU group (range: 60 to 305 patients), intravenous nivolumab and ipilimumab group (range: 59 to 307 patients) or cisplatin and 5-FU group (range: 56 to 283 patients).

Previously-Treated Unresectable Advanced, Recurrent or Metastatic Esophageal Squamous Cell Carcinoma (ESCC)

ATTRACTION-3

The safety of intravenous nivolumab was evaluated in ATTRACTION-3, a randomized, active-controlled, open‑label, multicenter trial in 209 patients with unresectable advanced, recurrent or metastatic ESCC refractory or intolerant to at least one fluoropyrimidine- and platinum‑based chemotherapy [see Clinical Studies (14.11)]. The trial excluded patients who were refractory or intolerant to taxane therapy, had brain metastases that were symptomatic or required treatment, had autoimmune disease, used systemic corticosteroids or immunosuppressants, had apparent tumor invasion of organs adjacent to the esophageal tumor or had stents in the esophagus or respiratory tract. Patients received intravenous nivolumab 240 mg by intravenous infusion over 30 minutes every 2 weeks (n=209) or investigator’s choice: docetaxel 75 mg/m^2 intravenously every 3 weeks (n=65) or paclitaxel 100 mg/m^2 intravenously once a week for 6 weeks followed by 1 week off (n=143). Patients were treated until disease progression or unacceptable toxicity. The median duration of exposure was 2.6 months (range: 0 to 29.2 months) in intravenous nivolumab-treated patients and 2.6 months (range: 0 to 21.4 months) in docetaxel- or paclitaxel-treated patients. Among patients who received intravenous nivolumab, 26% were exposed for >6 months and 10% were exposed for >1 year.

Serious adverse reactions occurred in 38% of patients receiving intravenous nivolumab. Serious adverse reactions reported in ≥2% of patients who received intravenous nivolumab were pneumonia, esophageal fistula, interstitial lung disease and pyrexia. The following fatal adverse reactions occurred in patients who received intravenous nivolumab: interstitial lung disease or pneumonitis (1.4%), pneumonia (1.0%), septic shock (0.5%), esophageal fistula (0.5%), gastrointestinal hemorrhage (0.5%), pulmonary embolism (0.5%), and sudden death (0.5%).

Intravenous nivolumab was discontinued in 13% of patients and was delayed in 27% of patients for an adverse reaction.

Tables 45 and 46 summarize the adverse reactions and laboratory abnormalities, respectively, in ATTRACTION-3.

Table 45: Adverse Reactions Occurring in ≥10% of Patients Receiving Intravenous Nivolumab - ATTRACTION-3
Adverse Reaction | Intravenous Nivolumab; (n=209) |  | Docetaxel or Paclitaxel; (n=208)
Adverse Reaction | All Grades (%) | Grades 3-4 (%) | All Grades (%) | Grades 3-4 (%)
Skin and Subcutaneous Tissue
Rasha | 22 | 1.9 | 28 | 1
Pruritus | 12 | 0 | 7 | 0
Metabolism and Nutrition
Decreased appetiteb | 21 | 1.9 | 35 | 5
Gastrointestinal
Diarrheac | 18 | 1.9 | 17 | 1.4
Constipation | 17 | 0 | 19 | 0
Nausea | 11 | 0 | 20 | 0.5
Musculoskeletal and Connective Tissue
Musculoskeletal paind | 17 | 0 | 26 | 1.4
Infections
Upper respiratory tract infectione | 17 | 1 | 14 | 0
Pneumoniaf | 13 | 5 | 19 | 9
Respiratory, Thoracic and Mediastinal
Coughg | 16 | 0 | 14 | 0.5
General
Pyrexiah | 16 | 0.5 | 19 | 0.5
Fatiguei | 12 | 1.4 | 27 | 4.8
Blood and Lymphatic System
Anemiaj | 13 | 8 | 30 | 13
Endocrine
Hypothyroidismk | 11 | 0 | 1.4 | 0
Toxicity was graded per NCI CTCAE v4.
a Includes urticaria, drug eruption, eczema, eczema asteatotic, eczema nummular, palmar-plantar erythrodysesthesia syndrome, erythema, erythema multiforme, blister, skin exfoliation, Stevens-Johnson syndrome, dermatitis, dermatitis described as acneiform, bullous, or contact, and rash described as maculo-papular, generalized, or pustular.
b Includes hypophagia, and food aversion.
c Includes colitis.
d Includes spondylolisthesis, periarthritis, musculoskeletal chest pain, neck pain, arthralgia, back pain, myalgia, pain in extremity, arthritis, bone pain, and periarthritis calcarea.
e Includes influenza, influenza like illness, pharyngitis, nasopharyngitis, tracheitis, and bronchitis and upper respiratory infection with bronchitis.
f Includes pneumonia aspiration, pneumonia bacterial, and lung infection. Two patients (1.0%) died of pneumonia in the intravenous nivolumab treatment arm. Two patients (1.0%) died of pneumonia in the chemotherapy treatment arm; these deaths occurred with paclitaxel only.
g Includes productive cough.
h Includes tumor-associated fever.
i Includes asthenia.
j Includes hemoglobin decreased, and iron deficiency anemia.
k Includes blood thyroid stimulating hormone increased.

Table 46: Laboratory Abnormalities Worsening from Baselinea Occurring in ≥10% of Patients - ATTRACTION-3
Laboratory Abnormality | Intravenous Nivolumab; (n=209) |  | Docetaxel or Paclitaxel; (n=208)
Laboratory Abnormality | All Grades (%) | Grades 3-4 (%) | All Grades (%) | Grades 3-4 (%)
Chemistry
Increased creatinine | 78 | 0.5 | 68 | 0.5
Hyperglycemia | 52 | 5 | 62 | 5
Hyponatremia | 42 | 11 | 50 | 12
Increased AST | 40 | 6 | 30 | 1
Increased alkaline phosphatase | 33 | 4.8 | 24 | 1.0
Increased ALT | 31 | 5 | 22 | 1.9
Hypercalcemia | 22 | 6 | 14 | 2.9
Hyperkalemia | 22 | 0.5 | 31 | 1
Hypoglycemia | 14 | 1.4 | 14 | 0.5
Hypokalemia | 11 | 2.9 | 13 | 3.4
Hematology
Lymphopenia | 46 | 19 | 72 | 43
Anemia | 42 | 9 | 71 | 17
Leukopenia | 11 | 0.5 | 79 | 45
a Each test incidence is based on the number of patients who had both baseline and at least one on-study laboratory measurement available: intravenous nivolumab group (209 patients) and Docetaxel or Paclitaxel group (range: 207 to 208 patients).

Gastric Cancer, Gastroesophageal Junction Cancer, and Esophageal Adenocarcinoma

CHECKMATE-649

The safety of intravenous nivolumab in combination with chemotherapy was evaluated in CHECKMATE-649, a randomized, multicenter, open-label trial in patients with previously untreated advanced or metastatic gastric cancer, gastroesophageal junction cancer, and esophageal adenocarcinoma [see Clinical Studies (14.12)]. The trial excluded patients who were known human epidermal growth factor receptor 2 (HER2) positive or had untreated central nervous system (CNS) metastases. Patients were randomized to receive intravenous nivolumab in combination with chemotherapy or chemotherapy. Patients received one of the following treatments:

- intravenous nivolumab 240 mg in combination with mFOLFOX6 (fluorouracil, leucovorin and oxaliplatin) every 2 weeks or mFOLFOX6 every 2 weeks.
- intravenous nivolumab 360 mg in combination with CapeOX (capecitabine and oxaliplatin) every 3 weeks or CapeOX every 3 weeks.

Patients were treated with intravenous nivolumab in combination with chemotherapy or chemotherapy until disease progression, unacceptable toxicity, or up to 2 years. The median duration of exposure was 6.8 months (range: 0 to 33.5 months) in intravenous nivolumab and chemotherapy-treated patients. Among patients who received intravenous nivolumab and chemotherapy, 54% were exposed for >6 months and 28% were exposed for >1 year.

Fatal adverse reactions occurred in 16 (2.0%) patients who were treated with intravenous nivolumab in combination with chemotherapy; these included pneumonitis (4 patients), febrile neutropenia (2 patients), stroke (2 patients), gastrointestinal toxicity, intestinal mucositis, septic shock, pneumonia, infection, gastrointestinal bleeding, mesenteric vessel thrombosis, and disseminated intravascular coagulation. Serious adverse reactions occurred in 52% of patients treated with intravenous nivolumab in combination with chemotherapy. Intravenous nivolumab and/or chemotherapy were discontinued in 44% of patients and at least one dose was withheld in 76% of patients due to an adverse reaction.

The most frequent serious adverse reactions reported in ≥2% of patients treated with intravenous nivolumab in combination with chemotherapy were vomiting (3.7%), pneumonia (3.6%), anemia (3.6%), pyrexia (2.8%), diarrhea (2.7%), febrile neutropenia (2.6%), and pneumonitis (2.4%). The most common adverse reactions reported in ≥20% of patients treated with intravenous nivolumab in combination with chemotherapy were peripheral neuropathy, nausea, fatigue, diarrhea, vomiting, decreased appetite, abdominal pain, constipation, and musculoskeletal pain.

Tables 47 and 48 summarize the adverse reactions and laboratory abnormalities, respectively, in CHECKMATE-649.

Table 47: Adverse Reactions in ≥10% of Patients Receiving Intravenous Nivolumab and Chemotherapy - CHECKMATE-649
Adverse Reaction | Intravenous Nivolumab and mFOLFOX6 or CapeOX; (n=782) |  | mFOLFOX6 or CapeOX (n=767)
Adverse Reaction | All Grades (%) | Grades 3-4 (%) | All Grades (%) | Grades 3-4 (%)
Adverse Reaction | 99 | 69 | 98 | 59
Nervous System
Peripheral neuropathya | 53 | 7 | 46 | 4.8
Headache | 11 | 0.8 | 6 | 0.3
Gastrointestinal
Nausea | 48 | 3.2 | 44 | 3.7
Diarrhea | 39 | 5 | 34 | 3.7
Vomiting | 31 | 4.2 | 29 | 4.2
Abdominal painb | 27 | 2.8 | 24 | 2.6
Constipation | 25 | 0.6 | 21 | 0.4
Stomatitisc | 17 | 1.8 | 13 | 0.8
General
Fatigued | 44 | 7 | 40 | 5
Pyrexiae | 19 | 1 | 11 | 0.4
Edemaf | 12 | 0.5 | 8 | 0.1
Metabolism and Nutrition
Decreased appetite | 29 | 3.6 | 26 | 2.5
Hypoalbuminemiag | 14 | 0.3 | 9 | 0.3
Investigations
Weight decreased | 17 | 1.3 | 15 | 0.7
Increased lipase | 14 | 7 | 8 | 3.7
Increased amylase | 12 | 3.1 | 5 | 0.4
Musculoskeletal and Connective Tissue
Musculoskeletal painh | 20 | 1.3 | 14 | 2
Skin and Subcutaneous Tissue
Rashi | 18 | 1.7 | 4.4 | 0.1
Palmar-plantar erythrodysesthesia syndrome | 13 | 1.5 | 12 | 0.8
Respiratory, Thoracic and Mediastinal
Coughj | 13 | 0.1 | 9 | 0
Infections and Infestations
Upper respiratory tract infectionk | 10 | 0.1 | 7 | 0.1
Toxicity was graded per NCI CTCAE v4.
a Includes dysesthesia, hypoesthesia, peripheral motor neuropathy, peripheral sensorimotor neuropathy, and peripheral sensory neuropathy.
b Includes abdominal discomfort, abdominal pain lower, and abdominal pain upper.
c Includes aphthous ulcer, mouth ulceration, and mucosal inflammation.
d Includes asthenia.
e Includes tumor associated fever.
f Includes swelling, generalized edema, edema peripheral, and peripheral swelling.
g Includes blood albumin decreased.
h Includes back pain, bone pain, musculoskeletal chest pain, musculoskeletal discomfort, myalgia, neck pain, pain in extremity, and spinal pain.
i Includes dermatitis, dermatitis acneiform, dermatitis allergic, dermatitis bullous, drug eruption, exfoliative rash, nodular rash, rash erythematous, rash macular, rash maculo-papular, rash papular, rash pruritic, and rash vesicular.
j Includes productive cough.
k Includes nasopharyngitis, pharyngitis, and rhinitis.

Table 48: Laboratory Values Worsening from Baselinea Occurring in ≥10% of Patients - CHECKMATE-649
Laboratory Abnormality | Intravenous Nivolumab and mFOLFOX6 or CapeOX (n=782) |  | mFOLFOX6 or CapeOX (n=767)
Laboratory Abnormality | Grades 1-4 (%) | Grades 3-4 (%) | Grades 1-4 (%) | Grades 3-4 (%)
Hematology
Neutropenia | 73 | 29 | 62 | 23
Leukopenia | 69 | 12 | 59 | 9
Thrombocytopenia | 68 | 7 | 63 | 4.4
Anemia | 59 | 14 | 60 | 10
Lymphopenia | 59 | 12 | 49 | 9
Chemistry
Increased AST | 52 | 4.6 | 47 | 1.9
Hypocalcemia | 42 | 1.6 | 37 | 1
Hyperglycemia | 41 | 3.9 | 38 | 2.7
Increased ALT | 37 | 3.4 | 30 | 1.9
Hyponatremia | 34 | 6 | 24 | 5
Hypokalemia | 27 | 7 | 24 | 4.8
Hyperbilirubinemia | 24 | 2.8 | 21 | 2
Increased creatinine | 15 | 1 | 9 | 0.5
Hyperkalemia | 14 | 1.4 | 11 | 0.7
Hypoglycemia | 12 | 0.7 | 9 | 0.2
Hypernatremia | 11 | 0.5 | 7.1 | 0
a Each test incidence is based on the number of patients who had both baseline and at least one on-study laboratory measurement available: intravenous nivolumab and mFOLFOX6 or CapeOX group (407 to 767 patients) or mFOLFOX6 or CapeOX group (range: 405 to 735 patients).

6.2 Postmarketing Experience

The following adverse reactions have been identified during post-approval use of intravenous nivolumab. Because these reactions are reported voluntarily from a population of uncertain size, it is not always possible to reliably estimate their frequency or establish a causal relationship to drug exposure.

Eye: Vogt-Koyanagi-Harada (VKH) syndrome

Complications of Intravenous Nivolumab Treatment After Allogeneic HSCT: Treatment refractory, severe acute and chronic GVHD

Blood and lymphatic system disorders: Hemophagocytic lymphohistiocytosis (HLH) (including fatal cases), autoimmune hemolytic anemia (including fatal cases)

8 USE IN SPECIFIC POPULATIONS

8.1 Pregnancy

Risk Summary

Based on data from animal studies and its mechanism of action [see Clinical Pharmacology (12.1)], OPDIVO QVANTIG can cause fetal harm when administered to a pregnant woman. In animal reproduction studies, administration of nivolumab to cynomolgus monkeys from the onset of organogenesis through delivery resulted in increased abortion and premature infant death (see Data). Human IgG4 is known to cross the placental barrier and nivolumab is an immunoglobulin G4 (IgG4); therefore, nivolumab has the potential to be transmitted from the mother to the developing fetus. The effects of OPDIVO QVANTIG are likely to be greater during the second and third trimesters of pregnancy. There are no available data on OPDIVO QVANTIG use in pregnant women to evaluate a drug-associated risk. Advise pregnant women of the potential risk to a fetus.

The background risk in the U.S. general population of major birth defects is 2% to 4% and of miscarriage is 15% to 20% of clinically recognized pregnancies.

Data

Animal Data

OPDIVO QVANTIG for subcutaneous injection contains nivolumab and hyaluronidase [see Description (11)].

Nivolumab

A central function of the PD-1/PD-L1 pathway is to preserve pregnancy by maintaining maternal immune tolerance to the fetus. Blockade of PD-L1 signaling has been shown in murine models of pregnancy to disrupt tolerance to the fetus and to increase fetal loss. The effects of nivolumab on prenatal and postnatal development were evaluated in monkeys that received nivolumab intravenously twice weekly from the onset of organogenesis through delivery, at exposure levels of between 4 and 15 times higher than those observed at the clinical dose of 600 mg once every 2 weeks, 900 mg once every 3 weeks, or 1,200 mg once every 4 weeks (based on AUC). Nivolumab administration resulted in a non-dose-related increase in spontaneous abortion and increased neonatal death. Based on its mechanism of action, fetal exposure to nivolumab may increase the risk of developing immune-mediated disorders or altering the normal immune response, and immune-mediated disorders have been reported in PD-1 knockout mice. In surviving infants (18 of 32 compared to 11 of 16 vehicle-exposed infants) of cynomolgus monkeys treated with nivolumab, there were no apparent malformations and no effects on neurobehavioral, immunological, or clinical pathology parameters throughout the 6-month postnatal period.

Hyaluronidase

In an embryo-fetal development study, mice were dosed daily by subcutaneous injection during the period of organogenesis with hyaluronidase (recombinant human) at dose levels up to 2,200,000 U/kg, which is at least 6,600 times higher than the human dose of 10,000 U once every 2 weeks, 15,000 U once every 3 weeks, or 20,000 U once every 4 weeks (U/kg basis), when administered with nivolumab. The study found no evidence of teratogenicity. Reduced fetal weight and increased numbers of fetal resorptions were observed, with no effects found at a daily dose of 360,000 U/kg, which is at least 1,080 times higher than the human dose of 10,000 U once every 2 weeks, 15,000 U once every 3 weeks, or 20,000 U once every 4 weeks (U/kg basis), when administered with nivolumab.

8.2 Lactation

Risk Summary

There are no data on the presence of nivolumab or hyaluronidase in human milk, the effects on the breastfed child, or the effects on milk production. Because of the potential for serious adverse reactions in the breastfed child, advise women not to breastfeed during treatment and for 5 months after the last dose of OPDIVO QVANTIG.

8.3 Females and Males of Reproductive Potential

Pregnancy Testing

Verify the pregnancy status of females of reproductive potential prior to initiating OPDIVO QVANTIG [see Use in Specific Populations (8.1)].

Contraception

OPDIVO QVANTIG can cause fetal harm when administered to a pregnant woman [see Use in Specific Populations (8.1)]. Advise females of reproductive potential to use effective contraception during treatment with OPDIVO QVANTIG and for 5 months following the last dose.

8.4 Pediatric Use

The safety and effectiveness of OPDIVO QVANTIG have been established in pediatric patients aged 12 years and older who weigh 30 kg or greater for the following indications:

- Unresectable or metastatic melanoma [see Indications and Usage (1.2)]
- Unresectable or metastatic melanoma following combination treatment with intravenous nivolumab and ipilimumab [see Indications and Usage (1.2)]
- Completely resected Stage IIB, Stage IIC, Stage III, or Stage IV melanoma as adjuvant treatment [see Indications and Usage (1.3)]
- Unresectable or metastatic MSI-H or dMMR CRC following combination treatment with intravenous nivolumab and ipilimumab [see Indications and Usage (1.9)]
- MSI-H or dMMR mCRC that has progressed following treatment with a fluoropyrimidine, oxaliplatin, irinotecan [see Indications and Usage (1.9)]

Use of OPDIVO QVANTIG in pediatric patients for these indications is supported by evidence from adequate and well-controlled studies for intravenous nivolumab in adults and additional pharmacokinetic and safety data for intravenous nivolumab in pediatric patients 12 years and older who weigh 30 kg or greater [see Adverse Reactions (6.1) and Clinical Studies (14)]. Nivolumab exposure in pediatric patients 12 years and older who receive OPDIVO QVANTIG is predicted to be within range of those observed/predicted in adult patients at the recommended dosage [see Adverse Reactions (6.1), Clinical Pharmacology (12.3)].

The safety and effectiveness of OPDIVO QVANTIG have not been established for pediatric patients younger than 12 years old with melanoma or MSI-H or dMMR mCRC.

The safety and effectiveness of OPDIVO QVANTIG have not been established in pediatric patients for other approved adult indications [see Indications and Usage (1)].

8.5 Geriatric Use

Monotherapy

Of the 248 patients who were randomized to monotherapy OPDIVO QVANTIG in clinical studies, 48% were 65 years and over and 14% were 75 years and over. No overall differences in safety or effectiveness were observed between elderly patients and younger patients.

Single Agent Intravenous Nivolumab

Of 3569 patients with melanoma, NSCLC, renal cell carcinoma, urothelial carcinoma, ESCC, and esophageal or gastroesophageal junction cancer who were randomized to single agent intravenous nivolumab in clinical studies, 41% were 65 years and over and 10% were 75 years and over. No overall differences in safety or effectiveness were observed between elderly patients and younger patients [see Clinical Studies (14.1, 14.2, 14.3, 14.6, 14.8, 14.11, 14.12)].

Clinical studies in patients with recurrent head and neck SCC, or dMMR or MSI-H metastatic CRC (mCRC) who were treated with single agent intravenous nivolumab did not include sufficient numbers of patients aged 65 years and over to determine whether they respond differently from younger patients [see Clinical Studies (14.7, 14.9)].

Intravenous Nivolumab in Combination with Platinum-Containing Chemotherapy

Of the 179 patients with NSCLC who were randomized to intravenous nivolumab in combination with platinum-doublet chemotherapy, 48% were 65 years old or older and 6% were 75 years old or older. No overall differences in safety or effectiveness were reported between patients older and younger than 65 years [see Clinical Studies (14.4)].

Of the 229 patients with NSCLC who were randomized to intravenous nivolumab 360 mg in combination with platinum-doublet chemotherapy every 3 weeks for up to 4 cycles, followed by intravenous nivolumab 480 mg every 4 weeks, 56% were 65 years old or older and 7% were 75 years old or older. No overall differences in safety or effectiveness were reported between patients older and younger than 65 years.

Of the 1,110 patients with ESCC, GC, GEJC, or EAC who were randomized to intravenous nivolumab in combination with fluoropyrimidine- and platinum-containing chemotherapy, 42% were 65 years or older and 10% were 75 years or older. No overall difference in safety was reported between elderly patients and younger patients [see Clinical Studies (14.11, 14.12)].

Of the 304 patients with UC who were treated with intravenous nivolumab in combination with gemcitabine and platinum-doublet chemotherapy, 40% were 65 years or older and 11% were 75 years or older. No overall differences in safety or effectiveness were observed between patients 65 years of age and over and younger patients. Clinical studies of intravenous nivolumab with platinum-doublet chemotherapy did not include sufficient numbers of patients aged 75 years and over to determine whether safety and effectiveness differs compared to younger patients. [see Clinical Studies (14.8)].

In Combination with Cabozantinib

Of the 320 patients with renal cell carcinoma who were treated with intravenous nivolumab in combination with cabozantinib, 41% were 65 years or older and 9% were 75 years or older. No overall difference in safety was reported between elderly patients and younger patients [see Clinical Studies (14.1)].

11 DESCRIPTION

OPDIVO QVANTIG is a fixed-combination drug product containing nivolumab and hyaluronidase (human recombinant).

Nivolumab is a programmed death receptor-1 (PD-1) blocking antibody. Nivolumab is an IgG4 kappa immunoglobulin that has a calculated molecular mass of 146 kDa. It is expressed in a recombinant Chinese Hamster Ovary (CHO) cell line.

Hyaluronidase (human recombinant) is an endoglycosidase used to increase the dispersion and absorption of co-administered drugs when administered subcutaneously. Hyaluronidase (human recombinant) is a glycosylated single-chain protein produced by CHO cells containing a DNA plasmid encoding for a soluble fragment of human hyaluronidase (PH20). Hyaluronidase (human recombinant) has a molecular weight of approximately 61 kDa.

OPDIVO QVANTIG (nivolumab and hyaluronidase-nvhy) injection is a sterile, preservative-free, clear to opalescent, colorless to yellow solution that may contain a few translucent-to-white particles, supplied in a single-dose vial for subcutaneous use.

Each 2.5 mL single-dose vial contains 300 mg of nivolumab and 5,000 units of hyaluronidase (human recombinant), and the inactive ingredients: histidine (3.88 mg), histidine hydrochloride monohydrate (5.25 mg), methionine (1.87 mg), pentetic acid (0.049 mg), polysorbate 80 (1.25 mg), sucrose (214 mg), and Water for Injection, USP. The pH is 5.5 to 6.5.

Each 5 mL single-dose vial contains 600 mg of nivolumab and 10,000 units of hyaluronidase (human recombinant), and the inactive ingredients: histidine (7.75 mg), histidine hydrochloride monohydrate (10.5 mg), methionine (3.73 mg), pentetic acid (0.0985 mg), polysorbate 80 (2.5 mg), sucrose (428 mg), and Water for Injection, USP. The pH is 5.5 to 6.5.

12 CLINICAL PHARMACOLOGY

12.1 Mechanism of Action

Binding of the PD-1 ligands, PD-L1 and PD-L2, to the PD-1 receptor found on T cells, inhibits T-cell proliferation and cytokine production. Upregulation of PD-1 ligands occurs in some tumors and signaling through this pathway can contribute to inhibition of active T-cell immune surveillance of tumors. Nivolumab is a human immunoglobulin G4 (IgG4) monoclonal antibody that binds to the PD-1 receptor and blocks its interaction with PD-L1 and PD-L2, releasing PD-1 pathway-mediated inhibition of the immune response, including the anti-tumor immune response. In syngeneic mouse tumor models, blocking PD-1 activity resulted in decreased tumor growth.

Hyaluronan is a polysaccharide found in the extracellular matrix of the subcutaneous tissue. It is depolymerized by the naturally occurring enzyme hyaluronidase. Unlike the stable structural components of the interstitial matrix, hyaluronan has a half-life of approximately 0.5 days. Hyaluronidase increases permeability of the subcutaneous tissue by temporarily depolymerizing hyaluronan. In the doses administered, hyaluronidase in OPDIVO QVANTIG acts transiently and locally. The effects of hyaluronidase are reversible and permeability of the subcutaneous tissue is restored within 24 to 48 hours.

12.2 Pharmacodynamics

Exposure-Response Relationship

The exposure-response relationship and time course of pharmacodynamics of OPDIVO QVANTIG have not been fully characterized.

12.3 Pharmacokinetics

Nivolumab pharmacokinetics were characterized at cycle 1 and at steady state in patients with advanced solid tumors at the approved recommended dosages and are presented as geometric mean (CV%) unless otherwise specified.

When comparing nivolumab exposures following OPDIVO QVANTIG to those of intravenous nivolumab in CHECKMATE-67T [see Clinical Studies (14.1)], the geometric mean ratios (GMRs) (90% CI) for time-averaged concentration (Cavg) over 28 days and at steady state were 2.10 (2.00, 2.20) and 1.98 (1.87, 2.11), respectively, and for minimum concentration (Cmin) at 28 days and at steady state were 1.60 (1.49, 1.72) and 1.77 (1.63, 1.93), respectively.

Nivolumab steady state was achieved by 16 weeks. The systemic accumulation ratio was 2.3.

Absorption

Nivolumab bioavailability is 74% (14%). Peak concentrations occurred by approximately 6 days.

Distribution

The volume of distribution at steady state is 6.8 L (27%).

Elimination

Nivolumab clearance decreases over time, with a maximal reduction from baseline values of 24.5% (47.6%), resulting in a steady-state clearance of 8.2 mL/h (53.9%) in patients with metastatic tumors; this decrease in clearance is not considered clinically relevant. Nivolumab clearance does not decrease over time in patients with completely resected melanoma, as the clearance is 24% lower in this patient population compared with patients with metastatic melanoma at steady state.

The elimination half-life is 25 days (78%).

Specific Populations

No clinically significant differences in the pharmacokinetics of nivolumab were observed based on body weight (35 to 153 kg), sex, eGFR (24 to 124 mL/min/1.73 m^2), and performance status.

Pediatric Patients

Nivolumab exposures in pediatric patients 12 years and older who weigh 30 kg or greater are predicted to be within range of those observed in adults at the recommended dosage [see Dosage and Administration (2.3)].

12.6 Immunogenicity

The observed incidence of anti-drug antibodies is highly dependent on the sensitivity and specificity of the assay. Differences in assay methods preclude meaningful comparisons of the incidence of anti-drug antibodies in the studies described below with the incidence of anti-drug antibodies in other studies, including those of OPDIVO QVANTIG or of other nivolumab products or hyaluronidase products.

During the 2-year treatment period in CHECKMATE-67T [see Clinical Studies (14.1)], 23% (46/202) of patients who received OPDIVO QVANTIG developed anti-nivolumab antibodies (ADA) and 4.3% (2/46) had neutralizing antibodies against nivolumab (NAb). The corresponding incidence of ADA was 7% (15/215) and NAb was 0% (0/15) for intravenous nivolumab in the same study. The incidence of anti-hyaluronidase antibodies in CHECKMATE-67T was 8.8% (19/215); 5 (26%) of these 19 patients developed NAb.

Nivolumab clearance increased by approximately 26% in patients who received OPDIVO QVANTIG and tested positive for ADA compared to patients who tested negative for ADA; this change in clearance is not considered clinically significant. Local injection-site reactions were reported in 15% (7/46) of patients who developed ADA to nivolumab and 7% (10/155) of patients who did not develop ADA to nivolumab; however, all events were Grade 1 or 2 and resolved. Because of low occurrence of anti-nivolumab or anti-hyaluronidase antibodies, the effect of ADA on the effectiveness of OPDIVO QVANTIG is unknown.

13 NONCLINICAL TOXICOLOGY

13.1 Carcinogenesis, Mutagenesis, Impairment of Fertility

No studies have been performed to assess the potential of nivolumab for carcinogenicity or genotoxicity. Fertility studies have not been performed with nivolumab. In 1-month and 3-month repeat-dose toxicology studies in monkeys, there were no notable effects in the male and female reproductive organs; however, most animals in these studies were not sexually mature.

Hyaluronidases are found in most tissues of the body. Long-term animal studies have not been performed to assess the carcinogenic or mutagenic potential of hyaluronidase. In addition, when subcutaneous hyaluronidase (recombinant human) was administered to cynomolgus monkeys for 39 weeks at dose levels up to 220,000 U/kg, which is at least 600 times higher than the human dose (U/kg basis), of 10,000 U once every 2 weeks, 15,000 U once every 3 weeks, or 20,000 U once every 4 weeks, no evidence of toxicity to the male or female reproductive system was found through periodic monitoring of in-life parameters, e.g., semen analyses, hormone levels, menstrual cycles, and also from gross pathology, histopathology and organ weight data.

13.2 Animal Toxicology and/or Pharmacology

In animal models, inhibition of PD-1 signaling increased the severity of some infections and enhanced inflammatory responses. Mycobacterium tuberculosis–infected PD-1 knockout mice exhibit markedly decreased survival compared with wild-type controls, which correlated with increased bacterial proliferation and inflammatory responses in these animals. PD-1 blockade using a primate anti–PD-1 antibody was also shown to exacerbate M. tuberculosis infection in rhesus macaques. PD-1 knockout mice have also shown decreased survival following infection with lymphocytic choriomeningitis virus.

14 CLINICAL STUDIES

14.1 Advanced Renal Cell Carcinoma

Previously Treated Renal Cell Carcinoma - OPDIVO QVANTIG

The efficacy of OPDIVO QVANTIG was evaluated in CHECKMATE-67T (NCT04810078), a multicenter, randomized, open-label study in patients with advanced or metastatic clear cell renal cell carcinoma. Patients 18 years of age or older with histologically confirmed advanced or metastatic renal cell carcinoma with a clear cell component, including those with sarcomatoid features, and who received no more than 2 prior systemic treatment regimens were randomized to receive OPDIVO QVANTIG (containing 1,200 mg of nivolumab and 20,000 units of hyaluronidase) every 4 weeks subcutaneously, or nivolumab 3 mg/kg every 2 weeks intravenously. Patients with untreated, symptomatic central nervous system (CNS) metastases; leptomeningeal metastases; concurrent malignancies requiring treatment or history of prior malignancy within the previous 2 years; active, known, or suspected autoimmune disease; or who received prior treatment with a checkpoint inhibitor were excluded from the study. Patients with asymptomatic, stable CNS metastases that did not require immediate treatment were eligible if there was no evidence of progression within 28 days prior to the first dose of study drug administration. Stratification factors for randomization were weight (<80 kg vs ≥80 kg) and International Metastatic Renal Cell Carcinoma Database Consortium (IMDC) risk classification (favorable vs intermediate, vs poor risk). The primary objective was to assess the nivolumab exposure of subcutaneous administration of OPDIVO QVANTIG as compared to the intravenous administration of nivolumab. The secondary objective of the study was to evaluate overall response rate (ORR) by blinded independent central review (BICR).

A total of 495 patients were randomized to receive either OPDIVO QVANTIG (n=248) or intravenous nivolumab (n=247). The median age was 65 years (range: 20 to 93), with 51% ≥65 years of age and 14% ≥75 years of age; 68% male; 85% White, 12.5% not reported, 1% American Indian or Alaska Native, 0.8% Asian, and 0.4% Black; 36% Hispanic or Latino, 33% not Hispanic or Latino, and 31% not reported. Fifty-seven percent of patients weighed <80 kg and 43% weighed ≥80 kg. Baseline Karnofsky performance status was 70 (7%), 80 (20%), 90 (34%), or 100 (39%). Patient distribution by IMDC risk categories was 21% favorable, 62% intermediate, and 17% poor.

When comparing subcutaneous administration of OPDIVO QVANTIG to the intravenous administration of nivolumab, CHECKMATE-67T met the predefined acceptance margin for pharmacokinetic endpoints, with the lower boundary of 90% confidence interval of geometric mean ratios of not less than 0.8 for both serum nivolumab Cavg over 28 days and Cmin at steady state. [see Clinical Pharmacology 12.3]. Efficacy results are shown in Table 49.

Table 49: Efficacy Results - CHECKMATE-67T
 | OPDIVO QVANTIG; N=248 | Intravenous Nivolumab; N=247
ORR per BICR, n (%) | 60 (24) | 45 (18)
95% CIa | (19, 30) | (14, 24)
a Confidence interval based on the Clopper and Pearson method.

RCC Trials - Intravenous Nivolumab

The effectiveness of OPDIVO QVANTIG has been established for the following:

- as monotherapy, for advanced renal cell carcinoma (RCC) following treatment with intravenous nivolumab and ipilimumab combination therapy (CHECKMATE-214 study).
- in combination with cabozantinib, for the first-line treatment of adult patients with advanced RCC (CHECKMATE-9ER study).
- as monotherapy, for the treatment of adult patients with advanced RCC who have received prior anti-angiogenic therapy (CHECKMATE-025 study).

Use of OPDIVO QVANTIG for these RCC indications is supported by evidence from adequate and well-controlled studies conducted with intravenous nivolumab, and additional pharmacokinetic and safety data that demonstrated comparable pharmacokinetics and safety profiles between OPDIVO QVANTIG and intravenous nivolumab in the CHECKMATE-67T trial [see Adverse Reactions (6.1), Clinical Pharmacology (12.3), and Clinical Studies (14.1)]. Below is a description of the efficacy results of these adequate and well-controlled studies of intravenous nivolumab in these RCC populations.

First-line Renal Cell Carcinoma

CHECKMATE-214

CHECKMATE-214 (NCT02231749) was a randomized (1:1), open-label trial in patients with previously untreated advanced RCC. Patients were included regardless of their PD-L1 status. CHECKMATE-214 excluded patients with any history of or concurrent brain metastases, active autoimmune disease, or medical conditions requiring systemic immunosuppression. Patients were stratified by International Metastatic RCC Database Consortium (IMDC) prognostic score and region.

Efficacy was evaluated in intermediate/poor risk patients with at least 1 or more of 6 prognostic risk factors as per the IMDC criteria (less than one year from time of initial renal cell carcinoma diagnosis to randomization, Karnofsky performance status <80%, hemoglobin less than the lower limit of normal, corrected calcium of >10 mg/dL, platelet count greater than the upper limit of normal, and absolute neutrophil count greater than the upper limit of normal).

Patients were randomized to nivolumab 3 mg/kg and ipilimumab 1 mg/kg intravenously every 3 weeks for 4 doses followed by nivolumab 3 mg/kg intravenously every two weeks (n=425), or sunitinib 50 mg orally daily for the first 4 weeks of a 6-week cycle (n=422). Treatment continued until disease progression or unacceptable toxicity.

The trial population characteristics were: median age was 61 years (range: 21 to 85) with 38% ≥65 years of age and 8% ≥75 years of age. The majority of patients were male (73%) and White (87%) and 26% and 74% of patients had a baseline KPS of 70% to 80% and 90% to 100%, respectively.

The major efficacy outcome measures were OS, PFS (independent radiographic review committee [IRRC]-assessed) and confirmed ORR (IRRC-assessed) in intermediate/poor risk patients. In this population, the trial demonstrated statistically significant improvement in OS and ORR for patients randomized to intravenous nivolumab and ipilimumab as compared with sunitinib (Table 50 and Figure 1). OS benefit was observed regardless of PD-L1 expression level. The trial did not demonstrate a statistically significant improvement in PFS. Efficacy results are shown in Table 50 and Figure 1.

Table 50: Efficacy Results - CHECKMATE-214
 | Intermediate/Poor-Risk
 | Intravenous Nivolumab and Ipilimumab (n=425) | Sunitinib (n=422)
Overall Survival
Deaths (%) | 140 (32.9) | 188 (44.5)
Median survival (months) | NRa | 25.9
Hazard ratio (99.8% CI)b | 0.63 (0.44, 0.89)
p-valuec,d | <0.0001
Confirmed Overall Response Rate (95% CI) | 41.6% (36.9, 46.5) | 26.5% (22.4, 31.0)
p-valuee,f | <0.0001
Complete response (CR) | 40 (9.4) | 5 (1.2)
Partial response (PR) | 137 (32.2) | 107 (25.4)
Median duration of response (months) (95% CI) | NRa (21.8, NRa) | 18.2 (14.8, NRa)
Progression-free Survival
Disease progression or death (%) | 228 (53.6) | 228 (54.0)
Median (months) | 11.6 | 8.4
Hazard ratio (99.1% CI)a | 0.82 (0.64, 1.05)
p-valuec | NSg
a Not Reached
b Based on a stratified proportional hazards model.
c Based on a stratified log-rank test.
d p-value is compared to alpha 0.002 in order to achieve statistical significance.
e Based on the stratified DerSimonian-Laird test.
f p-value is compared to alpha 0.001 in order to achieve statistical significance.
g Not Significant at alpha level of 0.009.

Figure 1: Overall Survival (Intermediate/Poor Risk Population) - CHECKMATE-214

CHECKMATE-214 also randomized 249 favorable risk patients as per IMDC criteria to intravenous nivolumab and ipilimumab (n=125) or to sunitinib (n=124). These patients were not evaluated as part of the efficacy analysis population. OS in favorable risk patients receiving intravenous nivolumab and ipilimumab compared to sunitinib has a hazard ratio of 1.45 (95% CI: 0.75, 2.81). The efficacy of intravenous nivolumab and ipilimumab in previously untreated renal cell carcinoma with favorable-risk disease has not been established.

CHECKMATE-9ER

CHECKMATE-9ER (NCT03141177) was a randomized, open-label study of intravenous nivolumab combined with cabozantinib versus sunitinib in patients with previously untreated advanced RCC. CHECKMATE-9ER excluded patients with autoimmune disease or other medical conditions requiring systemic immunosuppression. Patients were stratified by IMDC prognostic score (favorable vs. intermediate vs. poor), PD-L1 tumor expression (≥1% vs. <1% or indeterminate), and region (US/Canada/Western Europe/Northern Europe vs. Rest of World).

Patients were randomized to nivolumab 240 mg intravenously every 2 weeks and cabozantinib 40 mg orally daily (n=323), or sunitinib 50 mg orally daily for the first 4 weeks of a 6-week cycle (4 weeks on treatment followed by 2 weeks off) (n=328). Treatment continued until disease progression per RECIST v1.1 or unacceptable toxicity. Treatment beyond RECIST‑defined disease progression was permitted if the patient was clinically stable and considered to be deriving clinical benefit by the investigator. Tumor assessments were performed at baseline, after randomization at Week 12, then every 6 weeks until Week 60, and then every 12 weeks thereafter.

The trial population characteristics were: median age 61 years (range: 28 to 90) with 38% ≥65 years of age and 10% ≥75 years of age. The majority of patients were male (74%) and White (82%) and 23% and 77% of patients had a baseline KPS of 70% to 80% and 90% to 100%, respectively. Patient distribution by IMDC risk categories was 22% favorable, 58% intermediate, and 20% poor.

The major efficacy outcome measure was PFS (BICR assessed). Additional efficacy outcome measures were OS and ORR (BICR assessed). The trial demonstrated a statistically significant improvement in PFS, OS, and ORR for patients randomized to intravenous nivolumab and cabozantinib compared with sunitinib. Consistent results for PFS were observed across pre-specified subgroups of IMDC risk categories and PD-L1 tumor expression status. An updated OS analysis was conducted when 271 deaths were observed based on the pre-specified number of deaths for the pre-planned final analysis of OS. Efficacy results are shown in Table 51 and Figures 2 and 3.

Table 51: Efficacy Results - CHECKMATE-9ER
 | Intravenous Nivolumab and Cabozantinib (n=323) | Sunitinib (n=328)
Progression-free Survival
Disease progression or death (%) | 144 (45) | 191 (58)
Median PFS (months)a (95% CI) | 16.6 (12.5, 24.9) | 8.3 (7.0, 9.7)
Hazard ratio (95% CI)b | 0.51 (0.41, 0.64)
p-valuec,d | <0.0001
Overall Survival
Deaths (%) | 67 (21) | 99 (30)
Median OS (months)a (95% CI) | NRe | NR (22.6, NRe)
Hazard ratio (98.89% CI)b | 0.60 (0.40, 0.89)
p-valuec,d,f | 0.0010
Updated Overall Survival
Deaths (%) | 121 (37) | 150 (46)
Median OS (months)a (95% CI) | 37.7 (35.5, NR) | 34.3 (29.0, NR)
Hazard ratio (95% CI)b | 0.70 (0.55, 0.90)
Confirmed Objective Response Rate (95% CI)g | 55.7% (50.1, 61.2) | 27.1% (22.4, 32.3)
p-valueh | <0.0001
Complete Response | 26 (8%) | 15 (4.6%)
Partial Response | 154 (48%) | 74 (23%)
Median duration of response in months (95% CI)a | 20.2 (17.3, NRe) | 11.5 (8.3, 18.4)
a Based on Kaplan-Meier estimates.
b Stratified Cox proportional hazards model.
c Based on stratified log-rank test
d 2-sided p-values from stratified log-rank test.
e Not Reached
f p-value is compared with the allocated alpha of 0.0111 for this interim analysis
g CI based on the Clopper-Pearson method.
h 2-sided p-value from Cochran-Mantel-Haenszel test.

Figure 2: Progression-free Survival - CHECKMATE-9ER

Figure 3: Updated Overall Survival - CHECKMATE-9ER

In an exploratory analysis, the updated analysis of OS in patients with IMDC favorable, intermediate, intermediate/poor, and poor risk demonstrated a HR (95% CI) of 1.03 (0.55, 1.92), 0.74 (0.54, 1.01), 0.65 (0.50, 0.85), and 0.49 (0.31, 0.79), respectively.

Previously Treated Renal Cell Carcinoma

CHECKMATE-025

CHECKMATE-025 (NCT01668784) was a randomized (1:1), open-label trial in patients with advanced RCC who had experienced disease progression during or after one or two prior anti-angiogenic therapy regimens. Patients had to have a Karnofsky Performance Score (KPS) ≥70% and patients were included regardless of their PD-L1 status. The trial excluded patients with any history of or concurrent brain metastases, prior treatment with an mTOR inhibitor, active autoimmune disease, or medical conditions requiring systemic immunosuppression. Patients were stratified by region, Memorial Sloan Kettering Cancer Center (MSKCC) Risk Group and the number of prior anti-angiogenic therapies. Patients were randomized to nivolumab 3 mg/kg by intravenous infusion every 2 weeks (n=410) or everolimus 10 mg orally daily (n=411). The first tumor assessments were conducted 8 weeks after randomization and continued every 8 weeks thereafter for the first year and then every 12 weeks until progression or treatment discontinuation, whichever occurred later. The major efficacy outcome measure was overall survival (OS).

The trial population characteristics were: median age was 62 years (range: 18 to 88) with 40% ≥65 years of age and 9% ≥75 years of age. The majority of patients were male (75%) and White (88%) and 34% and 66% of patients had a baseline KPS of 70% to 80% and 90% to 100%, respectively. The majority of patients (77%) were treated with one prior anti-angiogenic therapy. Patient distribution by MSKCC risk groups was 34% favorable, 47% intermediate, and 19% poor.

The trial demonstrated a statistically significant improvement in OS for patients randomized to intravenous nivolumab as compared with everolimus at the prespecified interim analysis when 398 events were observed (70% of the planned number of events for final analysis). OS benefit was observed regardless of PD-L1 expression level. Efficacy results are shown in Table 52 and Figure 4.

Table 52: Efficacy Results - CHECKMATE-025
 | Intravenous Nivolumab (n=410) | Everolimus (n=411)
Overall Survival
Deaths (%) | 183 (45) | 215 (52)
Median survival (months) (95% CI) | 25.0 (21.7, NRa) | 19.6 (17.6, 23.1)
Hazard ratio (95% CI)b | 0.73 (0.60, 0.89)
p-valuec,d | 0.0018
Confirmed Overall Response Rate (95% CI) | 21.5% (17.6, 25.8) | 3.9% (2.2, 6.2)
Median duration of response (months) (95% CI) | 23.0 (12.0, NRa) | 13.7 (8.3, 21.9)
Median time to onset of confirmed response (months) (min, max) | 3.0 (1.4, 13.0) | 3.7 (1.5, 11.2)
a Not Reached
b Based on a stratified proportional hazards model.
c Based on a stratified log-rank test.
d p-value is compared with 0.0148 of the allocated alpha for this interim analysis.

Figure 4: Overall Survival - CHECKMATE-025

14.2 Unresectable or Metastatic Melanoma

Previously Treated Metastatic Melanoma

The effectiveness of OPDIVO QVANTIG has been established for the treatment of previously treated unresectable or metastatic melanoma in adult and pediatric patients 12 years and older who weigh 30 kg or greater. Use of OPDIVO QVANTIG for this indication is supported by evidence from an adequate and well-controlled study conducted with intravenous nivolumab, and additional pharmacokinetic and safety data that demonstrated comparable pharmacokinetics and safety profiles between OPDIVO QVANTIG and intravenous nivolumab [see Adverse Reactions (6.1) and Clinical Pharmacology (12.3)]. Below is a description of the efficacy results of this adequate and well-controlled study of intravenous nivolumab in this melanoma population.

CHECKMATE-037

CHECKMATE-037 (NCT01721746) was a multicenter, open-label trial that randomized (2:1) patients with unresectable or metastatic melanoma to receive nivolumab 3 mg/kg intravenously every 2 weeks or investigator’s choice of chemotherapy, either single-agent dacarbazine 1000 mg/m^2 every 3 weeks or the combination of carboplatin AUC 6 intravenously every 3 weeks and paclitaxel 175 mg/m^2 intravenously every 3 weeks. Patients were required to have progression of disease on or following ipilimumab treatment and, if BRAF V600 mutation positive, a BRAF inhibitor. The trial excluded patients with autoimmune disease, medical conditions requiring systemic immunosuppression, ocular melanoma, active brain metastasis, or a history of Grade 4 ipilimumab-related adverse reactions (except for endocrinopathies) or Grade 3 ipilimumab‑related adverse reactions that had not resolved or were inadequately controlled within 12 weeks of the initiating event. Tumor assessments were conducted 9 weeks after randomization then every 6 weeks for the first year, and every 12 weeks thereafter.

Efficacy was evaluated in a single-arm, non-comparative, planned interim analysis of the first 120 patients who received intravenous nivolumab in CHECKMATE-037 and in whom the minimum duration of follow-up was 6 months. The major efficacy outcome measures in this population were confirmed overall response rate (ORR) as measured by blinded independent central review using Response Evaluation Criteria in Solid Tumors (RECIST 1.1) and duration of response.

Among the 120 patients treated with intravenous nivolumab, the median age was 58 years (range: 25 to 88), 65% of patients were male, 98% were White, and the ECOG performance score was 0 (58%) or 1 (42%). Disease characteristics were M1c disease (76%), BRAF V600 mutation positive (22%), elevated LDH (56%), history of brain metastases (18%), and two or more prior systemic therapies for metastatic disease (68%).

The ORR was 32% (95% confidence interval [CI]: 23, 41), consisting of 4 complete responses and 34 partial responses in intravenous nivolumab-treated patients. Of 38 patients with responses, 87% had ongoing responses with durations ranging from 2.6+ to 10+ months, which included 13 patients with ongoing responses of 6 months or longer.

There were responses in patients with and without BRAF V600 mutation-positive melanoma. A total of 405 patients were randomized and the median duration of OS was 15.7 months (95% CI: 12.9, 19.9) in nivolumab-treated patients compared to 14.4 months (95% CI: 11.7, 18.2) (HR 0.95; 95.54% CI: 0.73, 1.24) in patients assigned to investigator’s choice of treatment. Figure 5 summarizes the OS results.

Figure 5: Overall Survival - CHECKMATE-037*

* The primary OS analysis was not adjusted to account for subsequent therapies, with 54 (40.6%) patients in the chemotherapy arm subsequently receiving an anti-PD1 treatment. OS may be confounded by dropout, imbalance of subsequent therapies, and differences in baseline factors.

Previously Untreated Metastatic Melanoma

The effectiveness of OPDIVO QVANTIG has been established for the treatment of previously untreated unresectable or metastatic melanoma in adult and pediatric patients 12 years and older who weigh 30 kg or greater. Use of OPDIVO QVANTIG for this indication is supported by evidence from adequate and well-controlled studies conducted with intravenous nivolumab, and additional pharmacokinetic and safety data that demonstrated comparable pharmacokinetics and safety profiles between OPDIVO QVANTIG and intravenous nivolumab [see Adverse Reactions (6.1) and Clinical Pharmacology (12.3)]. Below is a description of the efficacy results of these adequate and well-controlled studies of intravenous nivolumab in this melanoma population.

CHECKMATE-066

CHECKMATE-066 (NCT01721772) was a multicenter, double-blind, randomized (1:1) trial in 418 patients with BRAF V600 wild-type unresectable or metastatic melanoma. Patients were randomized to receive either nivolumab 3 mg/kg by intravenous infusion every 2 weeks or dacarbazine 1000 mg/m^2 intravenously every 3 weeks until disease progression or unacceptable toxicity. Randomization was stratified by PD-L1 status (≥5% of tumor cell membrane staining by immunohistochemistry vs. <5% or indeterminate result) and M stage (M0/M1a/M1b versus M1c). Key eligibility criteria included histologically confirmed, unresectable or metastatic, cutaneous, mucosal, or acral melanoma; no prior therapy for metastatic disease; completion of prior adjuvant or neoadjuvant therapy at least 6 weeks prior to randomization; ECOG performance status 0 or 1; absence of autoimmune disease; and absence of active brain or leptomeningeal metastases. The trial excluded patients with ocular melanoma. Tumor assessments were conducted 9 weeks after randomization then every 6 weeks for the first year and then every 12 weeks thereafter. The major efficacy outcome measure was overall survival (OS). Additional outcome measures included investigator-assessed progression-free survival (PFS) and ORR per RECIST v1.1.

The trial population characteristics were: median age was 65 years (range: 18 to 87), 59% were male, and 99.5% were White. Disease characteristics were M1c stage disease (61%), cutaneous melanoma (74%), mucosal melanoma (11%), elevated LDH level (37%), PD-L1 ≥5% tumor cell membrane expression (35%), and history of brain metastasis (4%). More patients in the intravenous nivolumab arm had an ECOG performance status of 0 (71% vs. 58%).

CHECKMATE-066 demonstrated a statistically significant improvement in OS for the intravenous nivolumab arm compared with the dacarbazine arm in an interim analysis based on 47% of the total planned events for OS. At the time of analysis, 88% (63/72) of intravenous nivolumab-treated patients had ongoing responses, which included 43 patients with ongoing response of 6 months or longer. Efficacy results are shown in Table 53 and Figure 6.

Table 53: Efficacy Results - CHECKMATE-066
 | Intravenous Nivolumab (n=210) | Dacarbazine (n=208)
Overall Survival
Deaths (%) | 50 (24) | 96 (46)
Median (months) (95% CI) | NRa | 10.8 (9.3, 12.1)
Hazard ratio (95% CI)b | 0.42 (0.30, 0.60)
p-valuec,d | <0.0001
Progression-free Survival
Disease progression or death (%) | 108 (51) | 163 (78)
Median (months) (95% CI) | 5.1 (3.5, 10.8) | 2.2 (2.1, 2.4)
Hazard ratio (95% CI)b | 0.43 (0.34, 0.56)
p-valuec,d | <0.0001
Overall Response Rate | 34% | 9%
(95% CI) | (28, 41) | (5, 13)
Complete response rate | 4% | 1%
Partial response rate | 30% | 8%
a Not Reached.
b Based on a stratified proportional hazards model.
c Based on stratified log-rank test.
d p-value is compared with the allocated alpha of 0.0021 for this interim analysis.

Figure 6: Overall Survival - CHECKMATE-066

CHECKMATE-067

CHECKMATE-067 (NCT01844505) was a multicenter, randomized (1:1:1), double-blind trial in 945 patients with previously untreated, unresectable or metastatic melanoma to one of the following arms: intravenous nivolumab and ipilimumab, intravenous nivolumab, or ipilimumab. Patients were required to have completed adjuvant or neoadjuvant treatment at least 6 weeks prior to randomization and have no prior treatment with anti-CTLA-4 antibody and no evidence of active brain metastasis, ocular melanoma, autoimmune disease, or medical conditions requiring systemic immunosuppression.

Patients were randomized to receive:

- Intravenous nivolumab 1 mg/kg with ipilimumab 3 mg/kg intravenously every 3 weeks for 4 doses, followed by nivolumab as a single agent at a dose of 3 mg/kg by intravenous infusion every 2 weeks (nivolumab and ipilimumab arm),
- Nivolumab 3 mg/kg by intravenous infusion every 2 weeks (nivolumab arm), or
- Ipilimumab 3 mg/kg intravenously every 3 weeks for 4 doses, followed by placebo every 2 weeks (ipilimumab arm).

Randomization was stratified by PD-L1 expression (≥5% vs. <5% tumor cell membrane expression) as determined by a clinical trial assay, BRAF V600 mutation status, and M stage per the AJCC staging system (M0, M1a, M1b vs. M1c). Tumor assessments were conducted 12 weeks after randomization then every 6 weeks for the first year, and every 12 weeks thereafter. The major efficacy outcome measures were investigator-assessed PFS per RECIST v1.1 and OS. Additional efficacy outcome measures were confirmed ORR and duration of response.

The trial population characteristics were: median age 61 years (range: 18 to 90); 65% male; 97% White; ECOG performance score 0 (73%) or 1 (27%). Disease characteristics were: AJCC Stage IV disease (93%); M1c disease (58%); elevated LDH (36%); history of brain metastases (4%); BRAF V600 mutation-positive melanoma (32%); PD-L1 ≥5% tumor cell membrane expression as determined by the clinical trials assay (46%); and prior adjuvant therapy (22%).

CHECKMATE-067 demonstrated statistically significant improvements in OS and PFS for patients randomized to either intravenous nivolumab-containing arm as compared with the ipilimumab arm. The trial was not designed to assess whether adding ipilimumab to intravenous nivolumab improves PFS or OS compared to intravenous nivolumab as a single agent. Efficacy results are shown in Table 54 and Figure 7.

Table 54: Efficacy Results - CHECKMATE-067
 | Intravenous Nivolumab and Ipilimumab (n=314) | Intravenous Nivolumab (n=316) | Ipilimumab (n=315)
Overall Survivala
Deaths (%) | 128 (41) | 142 (45) | 197 (63)
Hazard ratiob (vs. ipilimumab); (95% CI) | 0.55; (0.44, 0.69) | 0.63; (0.50, 0.78)
p-valuec, d | <0.0001 | <0.0001
Progression-free Survivala
Disease progression or death | 151 (48%) | 174 (55%) | 234 (74%)
Median (months); (95% CI) | 11.5 (8.9, 16.7) | 6.9 (4.3, 9.5) | 2.9 (2.8, 3.4)
Hazard ratiob (vs. ipilimumab); (95% CI) | 0.42; (0.34, 0.51) | 0.57; (0.47, 0.69)
p-valuec, e | <0.0001 | <0.0001
Confirmed Overall Response Ratea | 50% | 40% | 14%
(95% CI) | (44, 55) | (34, 46) | (10, 18)
p-valuef | <0.0001 | <0.0001
Complete response | 8.9% | 8.5% | 1.9%
Partial response | 41% | 31% | 12%
Duration of Response
Proportion ≥6 months in duration | 76% | 74% | 63%
Range (months) | 1.2+ to 15.8+ | 1.3+ to 14.6+ | 1.0+ to 13.8+
a OS results are based on final OS analysis with 28 months of minimum follow-up; PFS (co-primary endpoint) and ORR (secondary endpoint) results were based on primary analysis with 9 months of minimum follow-up.
b Based on a stratified proportional hazards model.
c Based on stratified log-rank test.
d If the maximum of the two OS p-values is less than 0.04 (a significance level assigned by the Hochberg procedure), then both p-values are considered significant.
e p-value is compared with .005 of the allocated alpha for final PFS treatment comparisons.
f Based on the stratified Cochran-Mantel-Haenszel test.
+ Censored observation

Figure 7: Overall Survival - CHECKMATE-067

Based on a minimum follow-up of 48 months, the median OS was not reached (95% CI: 38.2, NR) in the intravenous nivolumab and ipilimumab arm. The median OS was 36.9 months (95% CI: 28.3, NR) in the intravenous nivolumab arm and 19.9 months (95% CI: 16.9, 24.6) in the ipilimumab arm.

Based on a minimum follow-up of 28 months, the median PFS was 11.7 months (95% CI: 8.9, 21.9) in the intravenous nivolumab and ipilimumab arm, 6.9 months (95% CI: 4.3, 9.5) in the intravenous nivolumab arm, and 2.9 months (95% CI: 2.8, 3.2) in the ipilimumab arm. Based on a minimum follow-up of 28 months, the proportion of responses lasting ≥24 months was 55% in the intravenous nivolumab and ipilimumab arm, 56% in the intravenous nivolumab arm, and 39% in the ipilimumab arm.

14.3 Adjuvant Treatment of Melanoma

The effectiveness of OPDIVO QVANTIG has been established for the adjuvant treatment of Stage IIB, Stage IIC, Stage III, or Stage IV melanoma in adult and pediatric patients 12 years and older who weigh 30 kg or greater. Use of OPDIVO QVANTIG for this indication is supported by evidence from adequate and well-controlled studies conducted with intravenous nivolumab [see Adverse Reactions (6.1) and Clinical Pharmacology (12.3)]. Below is a description of the efficacy results of these adequate and well-controlled studies of intravenous nivolumab in these melanoma populations.

CHECKMATE-76K

CHECKMATE-76K (NCT04099251) was a randomized, double-blind trial in 790 patients with completely resected Stage IIB/C melanoma. Patients were randomized (2:1) to receive nivolumab 480 mg or placebo by intravenous infusion every 4 weeks for up to 1 year or until disease recurrence or unacceptable toxicity. Enrollment required complete resection of the primary melanoma with negative margins and a negative sentinel lymph node within 12 weeks prior to randomization, and ECOG performance status of 0 or 1. The trial excluded patients with ocular/uveal or mucosal melanoma, autoimmune disease, any condition requiring systemic treatment with either corticosteroids (≥10 mg daily prednisone or equivalent) or other immunosuppressive medications, as well as patients with prior therapy for melanoma except surgery. Randomization was stratified by AJCC 8th staging system edition (T3b vs. T4a vs. T4b). The major efficacy outcome measure was recurrence-free survival (RFS) defined as the time between the date of randomization and the date of first recurrence (local, regional, or distant metastasis), new primary melanoma, or death, from any cause, whichever occurred first and as assessed by the investigator. Tumor assessments were conducted every 26 weeks during years 1-3 and every 52 weeks thereafter until year 5.

The trial population characteristics were: median age 62 years (range: 19 to 92), 61% were male, 98% were White, 0.4% Black or African American, 0.1% Asian, and 1.1% race unknown, 2.2% Hispanic or Latino, 58% Not Hispanic or Latino, 40% ethnicity unknown, and 94% had an ECOG performance status of 0. Sixty one percent had stage IIB and 39% had stage IIC melanoma.

CHECKMATE-76K demonstrated a statistically significant improvement in RFS for patients randomized to the intravenous nivolumab arm compared with the placebo arm. Efficacy results are shown in Table 55 and Figure 8.

Table 55: Efficacy Results - CHECKMATE-76K
 | Intravenous Nivolumab n=526 | Placebo n=264
Recurrence-free Survival
Number of events, n (%) | 66 (13%) | 69 (26%)
Median (months)b; (95% CI) | NRa; (28.5, NR) | NRa; (21.6, NR)
Hazard ratioc; (95% CI) p-valued | 0.42 (0.30, 0.59) p<0.0001
a Not reached.
b Based on Kaplan-Meier estimates.
c Hazard Ratio is intravenous nivolumab over placebo based on a stratified Cox proportional hazard model.
d Based on a 2-sided stratified log-rank test. Boundary for statistical significance: p-value <0.033.

Figure 8: Recurrence-free Survival - CHECKMATE-76K

CHECKMATE-238

CHECKMATE-238 (NCT02388906) was a randomized, double-blind trial in 906 patients with completely resected Stage IIIB/C or Stage IV melanoma. Patients were randomized (1:1) to receive nivolumab 3 mg/kg by intravenous infusion every 2 weeks or ipilimumab 10 mg/kg intravenously every 3 weeks for 4 doses then every 12 weeks beginning at Week 24 for up to 1 year. Enrollment required complete resection of melanoma with margins negative for disease within 12 weeks prior to randomization. The trial excluded patients with a history of ocular/uveal melanoma, autoimmune disease, and any condition requiring systemic treatment with either corticosteroids (≥10 mg daily prednisone or equivalent) or other immunosuppressive medications, as well as patients with prior therapy for melanoma except surgery, adjuvant radiotherapy after neurosurgical resection for lesions of the central nervous system, and prior adjuvant interferon completed ≥6 months prior to randomization. Randomization was stratified by PD-L1 status (positive [based on 5% level] vs. negative/indeterminate) and AJCC stage (Stage IIIB/C vs. Stage IV M1a-M1b vs. Stage IV M1c). The major efficacy outcome measure was recurrence-free survival (RFS) defined as the time between the date of randomization and the date of first recurrence (local, regional, or distant metastasis), new primary melanoma, or death, from any cause, whichever occurs first and as assessed by the investigator. Patients underwent imaging for tumor recurrence every 12 weeks for the first 2 years then every 6 months thereafter.

The trial population characteristics were: median age was 55 years (range: 18 to 86), 58% were male, 95% were White, and 90% had an ECOG performance status of 0. Disease characteristics were AJCC Stage IIIB (34%), Stage IIIC (47%), Stage IV (19%), M1a-b (14%), BRAF V600 mutation positive (42%), BRAF wild-type (45%), elevated LDH (8%), PD-L1 ≥5% tumor cell membrane expression determined by clinical trial assay (34%), macroscopic lymph nodes (48%), and tumor ulceration (32%).

CHECKMATE-238 demonstrated a statistically significant improvement in RFS for patients randomized to the intravenous nivolumab arm compared with the ipilimumab 10 mg/kg arm. Efficacy results are shown in Table 56 and Figure 9.

Table 56: Efficacy Results - CHECKMATE-238
 | Intravenous Nivolumab N=453 | Ipilimumab 10 mg/kg N=453
Recurrence-free Survival
Number of events, n (%) | 154 (34%) | 206 (45%)
Median (months); (95% CI) | NRa | NRa (16.56, NRa)
Hazard ratiob; (95% CI) p-valuec,d | 0.65 (0.53, 0.80) p<0.0001
Overall Survival
Number of events, n (%)e | 100 (22%) | 111 (25%)
Median (months); (95% CI) | NRa | NRa
Hazard ratiob; (95% CI) p-value | 0.87; (0.67, 1.14); 0.3148
a Not reached.
b Based on a stratified proportional hazards model.
c Based on a stratified log-rank test.
d p-value is compared with 0.0244 of the allocated alpha for this analysis.
e At the time of the final OS analysis, fewer overall survival events were observed than originally anticipated (approximately 302).

Figure 9: Recurrence-free Survival - CHECKMATE-238

14.4 Neoadjuvant Treatment of Resectable Non-Small Cell Lung Cancer

The effectiveness of OPDIVO QVANTIG has been established for the neoadjuvant treatment of resectable (tumors ≥4 cm or node positive) NSCLC in combination with platinum doublet chemotherapy. Use of OPDIVO QVANTIG for this indication is supported by evidence from adequate and well-controlled studies conducted with intravenous nivolumab (CHECKMATE-816, NCT02998528), and additional pharmacokinetic and safety data that demonstrated comparable pharmacokinetics and safety profiles between OPDIVO QVANTIG and intravenous nivolumab [see Adverse Reactions (6.1) and Clinical Pharmacology (12.3)]. Below is a description of the efficacy results of the adequate and well-controlled study of intravenous nivolumab in this lung cancer population.

CHECKMATE-816

CHECKMATE-816 (NCT02998528) was a randomized, open label trial in patients with resectable NSCLC. The trial included patients with resectable, histologically confirmed Stage IB (≥4 cm), II, or IIIA NSCLC (per the 7th edition American Joint Committee on Cancer/Union for International Cancer Control (AJCC/UICC) staging criteria), ECOG performance status 0 or 1, and measurable disease (per RECIST version 1.1). Patients with unresectable or metastatic NSCLC, known EGFR mutations or ALK translocations, Grade 2 or greater peripheral neuropathy, active autoimmune disease, or medical conditions requiring systemic immunosuppression were excluded from the study.

Patients were randomized to receive either:

- nivolumab 360 mg administered intravenously over 30 minutes and platinum-doublet chemotherapy administered intravenously every 3 weeks for up to 3 cycles, or
- platinum-doublet chemotherapy administered every 3 weeks for up to 3 cycles.

Platinum-doublet chemotherapy consisted of paclitaxel 175 mg/m^2 or 200 mg/m^2 and carboplatin AUC 5 or AUC 6 (any histology); pemetrexed 500 mg/m^2 and cisplatin 75 mg/m^2 (non-squamous histology); or gemcitabine 1000 mg/m^2 or 1250 mg/m^2 and cisplatin 75 mg/m^2 (squamous histology). In the platinum-doublet chemotherapy arm, two additional treatment regimen options included vinorelbine 25 mg/m^2 or 30 mg/m^2 and cisplatin 75 mg/m^2; or docetaxel 60 mg/m^2 or 75 mg/m^2 and cisplatin 75 mg/m^2 (any histology).

Stratification factors for randomization were tumor PD-L1 expression level (≥1% versus <1% or non-quantifiable), disease stage (IB/II versus IIIA), and sex (male versus female). Tumor assessments were performed at baseline, within 14 days of surgery, every 12 weeks after surgery for 2 years, then every 6 months for 3 years, and every year for 5 years until disease recurrence or progression. The major efficacy outcome measures were event-free survival (EFS) based on blinded independent central review (BICR) assessment and pathologic complete response (pCR) as evaluated by blinded independent pathology review (BIPR). Additional efficacy outcome measures included OS.

A total of 358 patients were randomized to receive either intravenous nivolumab in combination with platinum‑doublet chemotherapy (n=179) or platinum-doublet chemotherapy (n=179). The median age was 65 years (range: 34 to 84) with 51% of patients ≥65 years and 7% of patients ≥75 years, 50% were Asian, 47% were White, 2% were Black, and 71% were male. Baseline ECOG performance status was 0 (67%) or 1 (33%); 50% had tumors with PD-L1 expression ≥1%; 35% had stage IB/II and 64% had stage IIIA disease; 51% had tumors with squamous histology and 49% had tumors with non-squamous histology; and 89% were former/current smokers.

Eighty-three percent of patients in the intravenous nivolumab in combination with platinum-doublet chemotherapy arm had definitive surgery compared to 75% of patients in the platinum-doublet chemotherapy arm.

The study demonstrated statistically significant improvements in EFS and pCR. Efficacy results are presented in Table 57 and Figure 10.

Table 57: Efficacy Results - CHECKMATE-816
 | Intravenous Nivolumab and Platinum-Doublet Chemotherapy (n=179) | Platinum-Doublet Chemotherapy (n=179)
Event-free Survival (EFS) per BICR
Events (%) | 64 (35.8) | 87 (48.6)
Median (months) a; (95% CI) | 31.6; (30.2, NR) | 20.8; (14.0, 26.7)
Hazard Ratiob; (95% CI) | 0.63; (0.45, 0.87)
Stratified log-rank p-valuec | 0.0052
Pathologic Complete Response (pCR) per BIPR
Number of patients with pCR | 43 | 4
pCR Rate (%), (95% CI)d | 24.0 (18.0, 31.0) | 2.2 (0.6, 5.6)
Estimated treatment difference (95% CI)e | 21.6 (15.1, 28.2)
p-valuef | <0.0001
Minimum follow-up for EFS was 21 months.
a Kaplan-Meier estimate.
b Based on a stratified Cox proportional hazard model.
c Based on a stratified log-rank test. Boundary for statistical significance: p-value <0.0262.
d Based on Clopper and Pearson method.
e Strata-adjusted difference based on Cochran-Mantel-Haenszel method of weighting.
f From stratified CMH test.

Figure 10: Event-Free Survival - CHECKMATE-816

At the time of the EFS analysis, 26% of the patients had died. A prespecified interim analysis for OS resulted in a HR of 0.57 (95% CI: 0.38, 0.87), which did not cross the boundary for statistical significance.

14.5 Neoadjuvant and Adjuvant Treatment of Resectable Non-Small Cell Lung Cancer

The effectiveness of OPDIVO QVANTIG has been established for neoadjuvant treatment of resectable (tumors ≥4 cm or node positive) NSCLC and no EGFR mutations or ALK rearrangements in combination with platinum doublet chemotherapy followed by adjuvant treatment with intravenous nivolumab. Use of OPDIVO QVANTIG for this indication is supported by evidence from adequate and well-controlled studies conducted with intravenous nivolumab (CHECKMATE-77T, NCT04025879), and additional pharmacokinetic and safety data that demonstrated comparable pharmacokinetics and safety profiles between OPDIVO QVANTIG and intravenous nivolumab [see Adverse Reactions (6.1) and Clinical Pharmacology (12.3)]. Below is a description of the efficacy results of the adequate and well-controlled study of intravenous nivolumab in this lung cancer population.

CHECKMATE-77T

The efficacy of intravenous nivolumab, in combination with platinum-doublet chemotherapy, followed by surgery, and continued adjuvant treatment with intravenous nivolumab as a single agent, was investigated in CHECKMATE-77T (NCT04025879), a randomized, double-blind trial in 461 patients with resectable NSCLC. The trial included patients with resectable, suspected or histologically confirmed Stage IIA (>4 cm) to IIIB (T3-T4 N2) NSCLC (per the 8th edition American Joint Committee on Cancer (AJCC) Staging Manual), and ECOG performance status 0 or 1. Patients with unresectable or metastatic NSCLC, EGFR mutations or known ALK translocations, brain metastasis, Grade 2 or greater peripheral neuropathy, interstitial lung disease or active, non-infectious pneumonitis (symptomatic and/or requiring treatment), active autoimmune disease, or medical conditions requiring systemic immunosuppression were excluded from the study. Randomization was stratified by tumor PD-L1 expression level (≥1% versus <1% versus indeterminate/not evaluable), disease stage (Stage II versus Stage III), and tumor histology (squamous versus nonsquamous).

Patients were randomized (1:1) to receive either:

- Neoadjuvant nivolumab 360 mg administered intravenously over 30 minutes in combination with one of the following platinum-doublet chemotherapy regimens every 3 weeks for four cycles:
  - Paclitaxel 175 mg/m^2 or 200 mg/m^2 and carboplatin AUC 5 or AUC 6 (any histology)
  - Pemetrexed 500 mg/m2, and cisplatin 75 mg/m^2 or carboplatin AUC 5 or AUC 6 (nonsquamous histology)
  - Cisplatin 75 mg/m^2 and docetaxel 75 mg/m2 (squamous histology).
Within 90 days after the surgery, nivolumab 480 mg was administered intravenously over 30 minutes every 4 weeks.

or

- Neoadjuvant placebo administered intravenously over 30 minutes in combination with platinum-doublet chemotherapy (see above) every 3 weeks for four cycles. Within 90 days after the surgery, placebo was administered intravenously over 30 minutes every 4 weeks.

All study medications were administered via intravenous infusion. Treatment continued until disease progression, recurrence, or unacceptable toxicity for up to 13 cycles (1 year). Tumor assessments were performed every 12 weeks for 2 years, then every 24 weeks for up to 5 years or until disease recurrence or progression was confirmed by BICR.

The trial was not designed to isolate the effect of intravenous nivolumab in each phase (neoadjuvant or adjuvant) of treatment.

The major efficacy outcome measure was event-free survival (EFS) based on BICR assessment. Additional efficacy outcome measures included overall survival (OS), pathologic complete response (pCR), and major pathologic response (MPR).

The median age was 66 years (range: 35 to 86); 71% were male; 72% were White, 25% were Asian, 1.7% were Black, and 1.5% were mixed race/ race unknown/ not reported; and 6% were Hispanic or Latino. Baseline ECOG performance status was 0 (62%) or 1 (38%); 56% had tumors with PD-L1 expression ≥1% and 40% had tumors with PD-L1 expression <1%; 35% had stage II and 64% had stage III disease; 23% had N1 disease and 39% had N2 disease; 51% had tumors with squamous histology and 49% had tumors with nonsquamous histology; and 90% were former/current smokers.

Seventy-eight percent of patients in the neoadjuvant intravenous nivolumab in combination with platinum-doublet chemotherapy followed by adjuvant intravenous nivolumab arm had definitive surgery compared to 77% of patients in the neoadjuvant placebo and platinum-doublet chemotherapy followed by placebo arm.

The study demonstrated a statistically significant improvement in EFS for patients treated with neoadjuvant intravenous nivolumab in combination with platinum-doublet chemotherapy followed by single agent intravenous nivolumab compared with patients randomized to placebo in combination with platinum-doublet chemotherapy followed by placebo. Efficacy results are presented in Table 58 and Figure 11.

Table 58: Efficacy Results - CHECKMATE-77T
 | Neoadjuvant Intravenous Nivolumab and Platinum-Doublet Chemotherapy/Adjuvant Intravenous Nivolumab; (n=229) | Neoadjuvant Placebo and Platinum-Doublet Chemotherapy/Adjuvant Placebo; (n=232)
Event-free Survival (EFS) per BICR
Events (%) | 76 (33%) | 113 (49%)
Median (months)a; (95% CI) | NR; (28.9, NR) | 18.4; (13.6, 28.1)
Hazard Ratiob; (95% CI) | 0.58; (0.43, 0.78)
Stratified log-rank p-valuec | 0.00025
a Kaplan-Meier estimate.
b Based on a stratified Cox proportional hazard model.
c Based on a stratified log-rank test. Boundary for statistical significance: p-value <0.0264.

Figure 11: Event-Free Survival - CHECKMATE-77T

In a pre-specified descriptive analysis, the pCR rate was 25% (95% CI: 20, 31) in the intravenous nivolumab arm and 4.7% (95% CI: 2.4, 8) in the placebo arm.

At the time of the EFS analysis, OS data were immature.

14.6 Metastatic Non-Small Cell Lung Cancer

Second-line Treatment of Metastatic NSCLC

The effectiveness of OPDIVO QVANTIG has been established for the treatment of NSCLC previously treated with platinum-based chemotherapy. Patients with EGFR or ALK genomic tumor aberrations should have disease progression on FDA-approved therapy for these aberrations prior to receiving OPDIVO QVANTIG. Use of OPDIVO QVANTIG for this indication is supported by evidence from adequate and well-controlled studies conducted with intravenous nivolumab, and additional pharmacokinetic and safety data that demonstrated comparable pharmacokinetics and safety profiles between OPDIVO QVANTIG and intravenous nivolumab [see Adverse Reactions (6.1) and Clinical Pharmacology (12.3)]. Below is a description of the efficacy results of this adequate and well-controlled study of intravenous nivolumab in this lung cancer population.

CHECKMATE-017

CHECKMATE-017 (NCT01642004) was a randomized (1:1), open-label trial in 272 patients with metastatic squamous NSCLC who had experienced disease progression during or after one prior platinum doublet-based chemotherapy regimen. Patients received nivolumab 3 mg/kg by intravenous infusion every 2 weeks (n=135) or docetaxel 75 mg/m^2 intravenously every 3 weeks (n=137). Randomization was stratified by prior paclitaxel vs. other prior treatment and region (US/Canada vs. Europe vs. Rest of World). This trial included patients regardless of their PD-L1 status. The trial excluded patients with autoimmune disease, medical conditions requiring systemic immunosuppression, symptomatic interstitial lung disease, or untreated brain metastasis. Patients with treated brain metastases were eligible if neurologically returned to baseline at least 2 weeks prior to enrollment, and either off corticosteroids, or on a stable or decreasing dose of <10 mg daily prednisone equivalents. The first tumor assessments were conducted 9 weeks after randomization and continued every 6 weeks thereafter. The major efficacy outcome measure was OS. Additional efficacy outcome measures were investigator-assessed ORR and PFS.

The trial population characteristics were: median age was 63 years (range: 39 to 85) with 44% ≥65 years of age and 11% ≥75 years of age. The majority of patients were White (93%) and male (76%); the majority of patients were enrolled in Europe (57%) with the remainder in US/Canada (32%) and the rest of the world (11%). Baseline ECOG performance status was 0 (24%) or 1 (76%) and 92% were former/current smokers. Baseline disease characteristics of the population as reported by investigators were Stage IIIb (19%), Stage IV (80%), and brain metastases (6%). All patients received prior therapy with a platinum-doublet regimen and 99% of patients had tumors of squamous-cell histology.

The trial demonstrated a statistically significant improvement in OS for patients randomized to intravenous nivolumab as compared with docetaxel at the prespecified interim analysis when 199 events were observed (86% of the planned number of events for final analysis). Efficacy results are shown in Table 59 and Figure 12.

Table 59: Efficacy Results - CHECKMATE-017
 | Intravenous Nivolumab (n=135) | Docetaxel (n=137)
Overall Survival
Deaths (%) | 86 (64%) | 113 (82%)
Median (months); (95% CI) | 9.2 (7.3, 13.3) | 6.0 (5.1, 7.3)
Hazard ratio (95% CI)a | 0.59 (0.44, 0.79)
p-valueb,c | 0.0002
Overall Response Rate | 27 (20%) | 12 (9%)
(95% CI) | (14, 28) | (5, 15)
p-valued | 0.0083
Complete response | 1 (0.7%) | 0
Median duration of response (months); (95% CI) | NRe (9.8, NRe) | 8.4 (3.6, 10.8)
Progression-free Survival
Disease progression or death (%) | 105 (78%) | 122 (89%)
Median (months) | 3.5 | 2.8
Hazard ratio (95% CI)a | 0.62 (0.47, 0.81)
p-valueb | 0.0004
a Based on a stratified proportional hazards model.
b Based on stratified log-rank test.
c p-value is compared with 0.0315 of the allocated alpha for this interim analysis.
d Based on the stratified Cochran-Mantel-Haenszel test.
e Not Reached

Figure 12: Overall Survival - CHECKMATE-017

Archival tumor specimens were retrospectively evaluated for PD-L1 expression. Across the trial population, 17% of 272 patients had non-quantifiable results. Among the 225 patients with quantifiable results, 47% had PD-L1 negative squamous NSCLC, defined as <1% of tumor cells expressing PD-L1 and 53% had PD-L1 positive squamous NSCLC defined as ≥1% of tumor cells expressing PD-L1. In pre-specified exploratory subgroup analyses, the hazard ratios for survival were 0.58 (95% CI: 0.37, 0.92) in the PD-L1 negative subgroup and 0.69 (95% CI: 0.45, 1.05) in the PD-L1 positive subgroup.

CHECKMATE-057

CHECKMATE-057 (NCT01673867) was a randomized (1:1), open-label trial in 582 patients with metastatic non-squamous NSCLC who had experienced disease progression during or after one prior platinum doublet‑based chemotherapy regimen. Appropriate prior targeted therapy in patients with known sensitizing EGFR mutation or ALK translocation was allowed. Patients received nivolumab 3 mg/kg by intravenous infusion every 2 weeks (n=292) or docetaxel 75 mg/m^2 intravenously every 3 weeks (n=290). Randomization was stratified by prior maintenance therapy (yes vs. no) and number of prior therapies (1 vs. 2). The trial excluded patients with autoimmune disease, medical conditions requiring systemic immunosuppression, symptomatic interstitial lung disease, or untreated brain metastasis. Patients with treated brain metastases were eligible if neurologically stable. The first tumor assessments were conducted 9 weeks after randomization and continued every 6 weeks thereafter. The major efficacy outcome measure was OS. Additional efficacy outcome measures were investigator-assessed ORR and PFS. In addition, prespecified analyses were conducted in subgroups defined by PD-L1 expression.

The trial population characteristics: median age was 62 years (range: 21 to 85) with 42% of patients ≥65 years and 7% of patients ≥75 years. The majority of patients were White (92%) and male (55%); the majority of patients were enrolled in Europe (46%) followed by the US/Canada (37%) and the rest of the world (17%). Baseline ECOG performance status was 0 (31%) or 1 (69%), 79% were former/current smokers, 3.6% had NSCLC with ALK rearrangement, 14% had NSCLC with EGFR mutation, and 12% had previously treated brain metastases. Prior therapy included platinum-doublet regimen (100%) and 40% received maintenance therapy as part of the first-line regimen. Histologic subtypes included adenocarcinoma (93%), large cell (2.4%), and bronchoalveolar (0.9%).

CHECKMATE-057 demonstrated a statistically significant improvement in OS for patients randomized to intravenous nivolumab as compared with docetaxel at the prespecified interim analysis when 413 events were observed (93% of the planned number of events for final analysis). Efficacy results are shown in Table 60 and Figure 13.

Table 60: Efficacy Results - CHECKMATE-057
 | Intravenous Nivolumab (n=292) | Docetaxel (n=290)
Overall Survival
Deaths (%) | 190 (65%) | 223 (77%)
Median (months); (95% CI) | 12.2 (9.7, 15.0) | 9.4 (8.0, 10.7)
Hazard ratio (95% CI)a | 0.73 (0.60, 0.89)
p-valueb,c | 0.0015
Overall Response Rate | 56 (19%) | 36 (12%)
(95% CI) | (15, 24) | (9, 17)
p-valued | 0.02
Complete response | 4 (1.4%) | 1 (0.3%)
Median duration of response (months); (95% CI) | 17 (8.4, NRe) | 6; (4.4, 7.0)
Progression-free Survival
Disease progression or death (%) | 234 (80%) | 245 (84%)
Median (months) | 2.3 | 4.2
Hazard ratio (95% CI)a | 0.92 (0.77, 1.11)
p-valueb | 0.39
a Based on a stratified proportional hazards model.
b Based on stratified log-rank test.
c p-value is compared with .0408 of the allocated alpha for this interim analysis.
d Based on the stratified Cochran-Mantel-Haenszel test.
e Not Reached.

Figure 13: Overall Survival - CHECKMATE-057

Archival tumor specimens were evaluated for PD-L1 expression following completion of the trial. Across the trial population, 22% of 582 patients had non-quantifiable results. Of the remaining 455 patients, the proportion of patients in retrospectively determined subgroups based on PD-L1 testing using the PD-L1 IHC 28-8 pharmDx assay were: 46% PD-L1 negative, defined as <1% of tumor cells expressing PD-L1 and 54% had PD-L1 expression, defined as ≥1% of tumor cells expressing PD-L1. Among the 246 patients with tumors expressing PD-L1, 26% had ≥1% but <5% tumor cells with positive staining, 7% had ≥5% but <10% tumor cells with positive staining, and 67% had ≥10% tumor cells with positive staining. Figures 14 and 15 summarize the results of prespecified analyses of OS and PFS in subgroups determined by percentage of tumor cells expressing PD-L1.

Figure 14: Forest Plot: OS Based on PD-L1 Expression - CHECKMATE-057

Figure 15: Forest Plot: PFS Based on PD-L1 Expression - CHECKMATE-057

14.7 Recurrent or Metastatic Squamous Cell Carcinoma of the Head and Neck

The effectiveness of OPDIVO QVANTIG has been established for the treatment of recurrent or metastatic squamous cell carcinoma of the head and neck with disease progression on or after platinum-based therapy. Use of OPDIVO QVANTIG for this indication is supported by evidence from an adequate and well-controlled study conducted with intravenous nivolumab, and additional pharmacokinetic and safety data that demonstrated comparable pharmacokinetics and safety profiles between OPDIVO QVANTIG and intravenous nivolumab [see Adverse Reactions (6.1) and Clinical Pharmacology (12.3)]. Below is a description of the efficacy results of the adequate and well-controlled study of intravenous nivolumab in this head and neck carcinoma population.

CHECKMATE-141

CHECKMATE-141 (NCT02105636) was a randomized (2:1), active-controlled, open-label trial enrolling patients with metastatic or recurrent SCCHN who had experienced disease progression during or within 6 months of receiving platinum-based therapy administered in either the adjuvant, neo-adjuvant, primary (unresectable locally advanced) or metastatic setting. The trial excluded patients with autoimmune disease, medical conditions requiring immunosuppression, recurrent or metastatic carcinoma of the nasopharynx, squamous cell carcinoma of unknown primary histology, salivary gland or non-squamous histologies (e.g., mucosal melanoma), or untreated brain metastasis. Patients with treated brain metastases were eligible if neurologically stable. Patients were randomized to receive nivolumab 3 mg/kg by intravenous infusion every 2 weeks or investigator’s choice of cetuximab (400 mg/m^2 initial dose intravenously followed by 250 mg/m^2 weekly), or methotrexate (40 to 60 mg/m^2 intravenously weekly), or docetaxel (30 to 40 mg/m^2 intravenously weekly).

Randomization was stratified by prior cetuximab treatment (yes/no). The first tumor assessments were conducted 9 weeks after randomization and continued every 6 weeks thereafter. The major efficacy outcome measure was OS. Additional efficacy outcome measures were PFS and ORR.

A total of 361 patients were randomized; 240 patients to the intravenous nivolumab arm and 121 patients to the investigator’s choice arm (docetaxel: 45%; methotrexate: 43%; and cetuximab: 12%). The trial population characteristics were: median age was 60 years (range: 28 to 83) with 31% ≥65 years of age, 83% were White, 12% Asian, and 4% were Black, and 83% male. Baseline ECOG performance status was 0 (20%) or 1 (78%), 76% were former/current smokers, 90% had Stage IV disease, 45% of patients received only one prior line of systemic therapy, the remaining 55% received two or more prior lines of systemic therapy, and 25% had HPVp16-positive tumors, 24% had HPV p16-negative tumors, and 51% had unknown status.

The trial demonstrated a statistically significant improvement in OS for patients randomized to intravenous nivolumab as compared with investigator’s choice at a pre-specified interim analysis (78% of the planned number of events for final analysis). There were no statistically significant differences between the two arms for PFS (HR=0.89; 95% CI: 0.70, 1.13) or ORR (13.3% [95% CI: 9.3, 18.3] vs. 5.8% [95% CI: 2.4, 11.6] for nivolumab and investigator’s choice, respectively). Efficacy results are shown in Table 61 and Figure 16.

Table 61: Overall Survival - CHECKMATE-141
 | Intravenous Nivolumab (n=240) | Cetuximab, Methotrexate or Docetaxel (n=121)
Overall Survival
Deaths (%) | 133 (55%) | 85 (70%)
Median (months); (95% CI) | 7.5; (5.5, 9.1) | 5.1; (4.0, 6.0)
Hazard ratio (95% CI)a | 0.70 (0.53, 0.92)
p-valueb,c | 0.0101
a Based on stratified proportional hazards model.
b Based on stratified log-rank test.
c p-value is compared with 0.0227 of the allocated alpha for this interim analysis.

Figure 16: Overall Survival - CHECKMATE-141

Archival tumor specimens were retrospectively evaluated for PD-L1 expression using the PD-L1 IHC 28-8 pharmDx assay. Across the trial population, 28% (101/361) of patients had non-quantifiable results. Among the 260 patients with quantifiable results, 43% (111/260) had PD-L1 negative SCCHN, defined as <1% of tumor cells expressing PD-L1, and 57% (149/260) had PD-L1 positive SCCHN, defined as ≥1% of tumor cells expressing PD-L1. In pre-specified exploratory subgroup analyses, the hazard ratio for survival was 0.89 (95% CI: 0.54, 1.45) with median survivals of 5.7 and 5.8 months for the nivolumab and chemotherapy arms, respectively, in the PD-L1 negative subgroup. The HR for survival was 0.55 (95% CI: 0.36, 0.83) with median survivals of 8.7 and 4.6 months for the nivolumab and chemotherapy arms, respectively, in the PD-L1 positive SCCHN subgroup.

14.8 Urothelial Carcinoma

Adjuvant Treatment of Urothelial Carcinoma (UC) at High Risk of Recurrence

The effectiveness of OPDIVO QVANTIG has been established for the adjuvant treatment of UC at high risk of recurrence. Use of OPDIVO QVANTIG for this indication is supported by evidence from an adequate and well-controlled study conducted with intravenous nivolumab, and additional pharmacokinetic and safety data that demonstrated comparable pharmacokinetics and safety profiles between OPDIVO QVANTIG and intravenous nivolumab [see Adverse Reactions (6.1) and Clinical Pharmacology (12.3)]. Below is a description of the efficacy results of the adequate and well-controlled study of intravenous nivolumab in this UC population.

CHECKMATE-274

CHECKMATE-274 (NCT02632409) was a randomized, double-blind, placebo‑controlled study of adjuvant intravenous nivolumab in patients who were within 120 days of radical resection (R0) of UC of the bladder or upper urinary tract (renal pelvis or ureter) at high risk of recurrence. High risk of recurrence was defined as either 1) ypT2-ypT4a or ypN^+ for patients who received neoadjuvant cisplatin or 2) pT3-pT4a or pN^+ for patients who did not receive neoadjuvant cisplatin and who also either were ineligible for or refused adjuvant cisplatin. Patients were randomized 1:1 to receive nivolumab 240 mg or placebo by intravenous infusion every 2 weeks until recurrence or until unacceptable toxicity for a maximum treatment duration of 1 year. Patients were stratified by pathologic nodal status (N+ vs. N0/x with <10 nodes removed vs. N0 with ≥10 nodes removed), tumor cells expressing PD-L1 (≥1% vs. <1%/indeterminate as determined by the central lab using the PD‑L1 IHC 28-8 pharmDx assay), and use of neoadjuvant cisplatin (yes vs. no).

The trial population characteristics were: median age of 67 years (range: 30 to 92); 76% male; 76% White, 22% Asian, 0.7% Black, and 0.1% American Indian or Alaska Native. Of the 335 (47%) of patients with node-positive UC, 44 (6%) had non–muscle-invasive (<pT2) primary tumors. ECOG performance status was 0 (63%), 1 (35%), or 2 (2%). Prior neoadjuvant cisplatin had been given to 43% of patients; of the 57% who did not receive prior neoadjuvant cisplatin, reasons listed were ineligibility (22%), patient preference (33%), and other/not reported (2%). Tumor PD-L1 expression was ≥1% in 40% of patients, and 21% of patients had upper tract UC.

The major efficacy outcome measures were investigator-assessed DFS in all randomized patients and in patients with tumors expressing PD-L1 ≥1%. DFS was defined as time to first recurrence (local urothelial tract, local non-urothelial tract, or distant metastasis), or death. Additional efficacy outcome measures included OS.

At the pre-specified interim analysis, CHECKMATE-274 demonstrated a statistically significant improvement in DFS for patients randomized to intravenous nivolumab vs. placebo in the all randomized patient population, as well as in the subpopulation of patients with PD-L1 ≥1%, as shown in Table 62 and Figure 17.

In exploratory subgroup analyses in patients with upper tract UC (n=149), no improvement in DFS was observed in the nivolumab arm compared to the placebo arm. The unstratified DFS hazard ratio estimate was 1.15 (95% CI: 0.74, 1.80).

In an exploratory subgroup analysis in patients with PD-L1 expression of <1% (n=414), the unstratified DFS hazard ratio estimate was 0.83 (95% CI: 0.64, 1.08).

OS data is immature with 33% of deaths in the overall randomized population. In the UTUC subpopulation, 37 deaths occurred (20 in the nivolumab arm, 17 in the placebo arm).

Table 62: Efficacy Results - CHECKMATE-274
 | All Randomized |  | PD-L1 ≥1%
 | Intravenous Nivolumab; (n=353) | Placebo; (n=356) | Intravenous Nivolumab; (n=140) | Placebo; (n=142)
Disease-free Survival
Eventsa, n (%); Local recurrence; Distant recurrence; Death | 170 (48); 47 (13); 108 (31); 14 (4) | 204 (57); 64 (18); 127 (36); 10 (3) | 55 (39); 10 (7); 40 (29); 5 (4) | 81 (57); 24 (17); 52 (37); 5 (4)
Median DFS (months)b; (95% CI) | 20.8; (16.5, 27.6) | 10.8; (8.3, 13.9) | N.R.; (21.2, N.E.) | 8.4; (5.6, 21.2)
Hazard ratioc; (95% CI) | 0.70; (0.57, 0.86) |  | 0.55; (0.39, 0.77)
p-value | 0.0008d |  | 0.0005e
N.R. Not Reached, N.E. Not Estimable
a Includes disease at baseline events (protocol deviations): n=1 in intravenous nivolumab arm and n=3 in placebo arm.
b Based on Kaplan-Meier estimates.
c Stratified Cox proportional hazard model. Hazard ratio is intravenous nivolumab over placebo.
d Log-rank test stratified by prior neoadjuvant cisplatin, pathological nodal status, PD-L1 status (≥1% vs <1%/indeterminate). Boundary for statistical significance in all randomized patients: p-value <0.01784.
e Log-rank test stratified by prior neoadjuvant cisplatin, pathological nodal status. Boundary for statistical significance in all randomized patients with PD-L1 ≥1%: p-value <0.01282.

Figure 17: Disease-free Survival in All Randomized Patients - CHECKMATE-274

First-line Treatment of Unresectable or Metastatic UC

The effectiveness of OPDIVO QVANTIG has been established for the first-line treatment of unresectable or metastatic UC in combination with cisplatin and gemcitabine. Use of OPDIVO QVANTIG for this indication is supported by evidence from an adequate and well-controlled study conducted with intravenous nivolumab, and additional pharmacokinetic and safety data that demonstrated comparable pharmacokinetics and safety profiles between OPDIVO QVANTIG and intravenous nivolumab [see Adverse Reactions (6.1) and Clinical Pharmacology (12.3)]. Below is a description of the efficacy results of the adequate and well-controlled study of intravenous nivolumab in this UC population.

CHECKMATE-901

CHECKMATE-901 (NCT 03036098) was a randomized, open-label study in patients with previously untreated unresectable or metastatic UC. Prior neoadjuvant or adjuvant chemotherapy were permitted as long as the disease recurrence took place ≥12 months from completion of therapy. Patients who were ineligible for cisplatin and those with active CNS metastases were excluded. Stratification factors for randomization were PD-L1 status (≥1% vs. <1% or indeterminate) and liver metastasis. Patients were randomized 1:1 to receive either:

- Intravenous nivolumab 360 mg and cisplatin 70 mg/m^2 on Day 1 and gemcitabine 1000 mg/m^2 on Days 1 and 8 of a 21-day cycle for up to 6 cycles followed by single-agent intravenous nivolumab 480 mg every 4 weeks until disease progression or unacceptable toxicity. In the absence of disease progression or unacceptable toxicity, intravenous nivolumab was continued for up to 2 years from first dose.
- Cisplatin 70 mg/m^2 on Day 1 and gemcitabine 1000 mg/m^2 on Days 1 and 8 of a 21-day cycle for up to 6 cycles, until disease progression or unacceptable toxicity.

The major efficacy outcome measures were OS and PFS as assessed by BICR using RECIST v1.1. Additional efficacy outcome measures included ORR as assessed by BICR.

The median age was 65 years of age (range: 32 to 86) with 51% of patients ≥65 years of age and 12% of patients ≥75 years of age, 23% were Asian, 72% were White, 0.3% were Black, 0.3% were American Indian or Alaska Native, 4.9% were Other, 12% were Hispanic or Latino, and 77% were male. Baseline ECOG performance status was 0 (53%) or 1 (46%). At baseline, 87% of patients had metastatic UC, including 20% with liver metastases, 11% had locally advanced UC, and 51% had UC histologic variants. Forty-nine (16%) in the intravenous nivolumab in combination with cisplatin-based chemotherapy arm and 43 (14%) in the cisplatin-based chemotherapy arm switched from cisplatin to carboplatin after at least one cycle of cisplatin.

Efficacy results are presented in Table 63 and Figures 18 and 19.

Table 63: Efficacy Results – CHECKMATE-901
 | Intravenous Nivolumab and Cisplatin and Gemcitabine (n=304) | Cisplatin and Gemcitabine (n=304)
Overall Survival (OS)
Events, n (%) | 172 (56.6) | 193 (63.5)
Median (months); (95% CI)a | 21.7 (18.6, 26.4) | 18.9 (14.7, 22.4)
Hazard ratio; (95% CI)b | 0.78 (0.63, 0.96)
p-valuec | 0.0171
Progression-free Survival (PFS)d
Events, n (%) | 211 (69.4) | 191 (62.8)
Median (months); (95% CI)a | 7.9 (7.6, 9.5) | 7.6 (6.0, 7.8)
Hazard ratio; (95% CI)b | 0.72 (0.59, 0.88)
p-valuec | 0.0012
Objective Response Rate (ORR)d
Response rate, n (%); (95% CI) | 175 (57.6%); (51.8, 63.2) | 131 (43.1%); (37.5, 48.9)
Complete response rate, n (%) | 66 (22%) | 36 (12%)
Partial response rate, n (%) | 109 (36%) | 95 (31%)
Duration of Response (DoR)
Median (months); (95% CI)a | 9.5 (7.6, 15.1) | 7.3 (5.7, 8.9)
a Based on Kaplan-Meier Estimates.
b Stratified Cox proportional hazard model.
c 2 sided p values from stratified log-rank test.
d Assessed by BICR.

Figure 18: Overall Survival - CHECKMATE-901

Figure 19: Progression-free Survival - CHECKMATE-901

Previously Treated Advanced or Metastatic Urothelial Carcinoma

The effectiveness of OPDIVO QVANTIG has been established for the treatment of patients with locally advanced or metastatic UC and disease progression during or following platinum-containing chemotherapy or within 12 months of neoadjuvant or adjuvant treatment with platinum-containing chemotherapy. Use of OPDIVO QVANTIG for this indication is supported by evidence from an adequate and well-controlled study conducted with intravenous nivolumab, and additional pharmacokinetic and safety data that demonstrated comparable pharmacokinetics and safety profiles between OPDIVO QVANTIG and intravenous nivolumab [see Adverse Reactions (6.1) and Clinical Pharmacology (12.3)]. Below is a description of the efficacy results of the adequate and well-controlled study of intravenous nivolumab in this UC population.

CHECKMATE-275

CHECKMATE-275 (NCT02387996) was a single-arm trial in 270 patients with locally advanced or metastatic UC who had disease progression during or following platinum-containing chemotherapy or who had disease progression within 12 months of treatment with a platinum-containing neoadjuvant or adjuvant chemotherapy regimen. Patients were excluded for active brain or leptomeningeal metastases, active autoimmune disease, medical conditions requiring systemic immunosuppression, and ECOG performance status >1. Patients received nivolumab 3 mg/kg by intravenous infusion every 2 weeks until unacceptable toxicity or either radiographic or clinical progression. Tumor response assessments were conducted every 8 weeks for the first 48 weeks and every 12 weeks thereafter. Major efficacy outcome measures included confirmed ORR as assessed by IRRC using RECIST v1.1 and DOR.

The median age was 66 years (range: 38 to 90), 78% were male, 86% were White. Twenty-seven percent had non-bladder urothelial carcinoma and 84% had visceral metastases. Thirty-four percent of patients had disease progression following prior platinum-containing neoadjuvant or adjuvant therapy. Twenty-nine percent of patients had received ≥2 prior systemic regimens in the metastatic setting. Thirty-six percent of patients received prior cisplatin only, 23% received prior carboplatin only, and 7% were treated with both cisplatin and carboplatin in the metastatic setting. Forty-six percent of patients had an ECOG performance status of 1. Eighteen percent of patients had a hemoglobin <10 g/dL, and twenty-eight percent of patients had liver metastases at baseline. Patients were included regardless of their PD-L1 status.

Tumor specimens were evaluated prospectively using the PD-L1 IHC 28-8 pharmDx assay at a central laboratory and the results were used to define subgroups for pre-specified analyses. Of the 270 patients, 46% were defined as having PD-L1 expression of ≥1% (defined as ≥1% of tumor cells expressing PD-L1). The remaining 54% of patients were classified as having PD-L1 expression of <1% (defined as <1% of tumor cells expressing PD-L1). Confirmed ORR in all patients and the two PD-L1 subgroups are shown in Table 64. Median time to response was 1.9 months (range: 1.6-7.2). In 77 patients who received prior systemic therapy only in the neoadjuvant or adjuvant setting, the ORR was 23.4% (95% CI: 14.5%, 34.4%).

Table 64: Efficacy Results - CHECKMATE-275
 | All Patients; N=270 | PD-L1 <1%; N=146 | PD-L1 ≥1%; N=124
Confirmed Overall Response Rate, n (%); (95% CI) | 53 (19.6%); (15.1, 24.9) | 22 (15.1%); (9.7, 21.9) | 31 (25.0%); (17.7, 33.6)
Complete response rate | 7 (2.6%) | 1 (0.7%) | 6 (4.8%)
Partial response rate | 46 (17.0%) | 21 (14.4%) | 25 (20.2%)
Median Duration of Responsea (months) (range) | 10.3 (1.9+, 12.0+) | 7.6 (3.7, 12.0+) | NRb (1.9+, 12.0+)
a Estimated from the Kaplan-Meier Curve.
b Not Reached.

14.9 Microsatellite Instability-High or Mismatch Repair Deficient Metastatic Colorectal Cancer

Treatment of MSI-H or dMMR mCRC

The effectiveness of OPDIVO QVANTIG has been established for the treatment of unresectable or metastatic microsatellite instability-high or mismatch repair deficient colorectal cancer (CRC) in adult and pediatric patients 12 years and older who weigh 30 kg or greater following treatment with intravenous nivolumab and ipilimumab combination therapy.

Use of OPDIVO QVANTIG for this indication is supported by evidence from an adequate and well-controlled study conducted with intravenous nivolumab (CHECKMATE-8HW, NCT03143153), and additional pharmacokinetic and safety data that demonstrated comparable pharmacokinetics and safety profiles between OPDIVO QVANTIG and intravenous nivolumab [see Adverse Reactions (6.1) and Clinical Pharmacology (12.3)]. Below is a description of the efficacy results of the adequate and well-controlled study of intravenous nivolumab in this CRC population.

CHECKMATE-8HW

CHECKMATE-8HW (NCT03143153) was a randomized, 3-arm, open-label trial in immunotherapy-naive patients across all lines of therapy with unresectable or metastatic CRC with known tumor MSI-H or dMMR (MSI-H/dMMR) status as determined in accordance with local standard of practice using PCR, NGS or IHC, assays. Central assessment of MSI-H status using PCR (Idylla MSI) test and dMMR status using IHC (Omnis MMR) test was conducted retrospectively on patient tumor specimens used for local MSI-H/dMMR status determination. Patients with confirmed MSI-H/dMMR status by either central test comprised the primary study population.

The trial excluded patients with brain metastasis that were symptomatic, had active autoimmune disease, used systemic corticosteroids or immunosuppressants, or had been treated with checkpoint inhibitors.

Patients were randomized to receive one of the following treatments:

- Intravenous nivolumab 240 mg every 3 weeks and ipilimumab 1 mg/kg every 3 weeks for a maximum of 4 doses, then intravenous nivolumab 480 mg every 4 weeks.
- Intravenous nivolumab 240 mg every 2 weeks for 6 doses, then intravenous nivolumab 480 mg every 4 weeks.
- Investigator’s choice chemotherapy
  ∘ mFOLFOX6 (oxaliplatin, leucovorin, and FU) with or without either bevacizumab or cetuximab: Oxaliplatin 85 mg/m^2, leucovorin 400 mg/m^2, and FU 400 mg/m^2 bolus followed by FU 2400 mg/m^2 over 46 hours every 2 weeks. Bevacizumab 5 mg/kg or cetuximab 500 mg/m^2 administered prior to mFOLFOX6 every 2 weeks.
  ∘ FOLFIRI (irinotecan, leucovorin, and FU) with or without either bevacizumab or cetuximab: Irinotecan 180 mg/m^2, leucovorin 400 mg/m^2, and FU 400 mg/m^2 bolus and FU 2400 mg/m^2 over 46 hours every 2 weeks. Bevacizumab 5 mg/kg on or cetuximab 500 mg/m^2 administered prior to FOLFIRI every 2 weeks.

Randomization was stratified by tumor location (right vs left) and by prior lines of therapy (0, 1, 2L+). Patients randomized to the chemotherapy arm could receive intravenous nivolumab in combination with ipilimumab upon progression assessed by BICR.

Study treatment was administered until disease progression, unacceptable toxicity, or for up to 2 years for patients who received intravenous nivolumab plus ipilimumab or intravenous nivolumab monotherapy. Patients who discontinued combination therapy because of an adverse reaction attributed to ipilimumab were permitted to continue intravenous nivolumab as a single agent. Intravenous nivolumab with or without ipilimumab could be administered beyond RECIST 1.1-assessed progressive disease if there was a clinical benefit as determined by investigator and therapy was tolerated. Tumor assessments per RECIST v1.1 were conducted every 6 weeks for the first 24 weeks, then every 8 weeks thereafter up until week 96, then every 16 weeks thereafter up until week 144, and then every 24 weeks.

The evaluation of efficacy relied on the comparison of patients with centrally confirmed MSI-H/dMMR mCRC randomized to intravenous nivolumab in combination with ipilimumab versus chemotherapy in the first line (1L) setting and the comparison of patients with centrally confirmed MSI-H/dMMR mCRC randomized to intravenous nivolumab plus ipilimumab vs intravenous nivolumab in all lines setting.

The major efficacy outcome measure was BICR-assessed PFS per RECIST 1.1. Additional efficacy outcome measures included ORR and duration of response assessed by BICR and OS.

The baseline characteristics of the total of 839 patients randomized were: the median age was 63 years (range: 20 to 87), with 46% ≥65 years of age and 14% ≥75 years of age; 50% were male and 87% were White, 9.3% were Asian, 1.5% Black or African American, and 2.3% other race; 9.2% were Hispanic or Latino, 50% Not Hispanic or Latino, 41% ethnicity unknown. Baseline ECOG performance status was 0 (52%) and 1 (48%); number of prior lines of therapy was 0 (56%), 1 (24%), and ≥2 (19%); and tumor location was right-sided or left-sided for 69% and 31% of patients, respectively. The baseline characteristics in patients with centrally confirmed MSI-H/dMMR is consistent with that of all randomized patients.

First-Line intravenous nivolumab in combination with ipilimumab

Among 303 patients in the first-line setting who were randomly assigned to intravenous nivolumab in combination with ipilimumab (202) and to chemotherapy (101), 171 and 84 patients had centrally confirmed MSI-H/dMMR status in intravenous nivolumab in combination with ipilimumab arm and chemotherapy arm, respectively.

In the 1L setting 200 of 202 patients assigned to receive intravenous nivolumab combined with ipilimumab and 88 of 101 patients assigned to receive chemotherapy received at least 1 dose of study treatment. Among the 88 patients who received chemotherapy, 58% and 42% of patients received oxaliplatin-containing regimens and irinotecan-containing regimens, respectively, and 66 (75%) patients received a targeted agent, either bevacizumab (64%) or cetuximab (11%).

The BICR-assessed PFS efficacy results for patients with centrally confirmed MSI-H/dMMR randomized to the intravenous nivolumab and ipilimumab arm compared with chemotherapy in the 1L setting are presented in Table 65 and Figure 20. The comparative results of ORR and OS between arms were not available at the time of the PFS analysis due to statistical testing strategy.

Table 65: Efficacy Results, First-Line - CHECKMATE-8HW
 | Intravenous Nivolumab and Ipilimumab (n=171) | Chemotherapy (n=84)
Progression-free Survival
Disease progression or death (%) | 48 (28) | 52 (62)
Median in monthsb (95% CI) | NR; (38.4, NE) | 5.8; (4.4, 7.8)
Hazard ratioc (95% CI) | 0.21 (0.14, 0.32)
p-valuea | <0.0001
NR: Not Reached; NE: Not Estimable.
Minimum follow-up was 6.1 months at data cutoff date 12Oct2023.
a Based on log-rank test stratified by the same factors as used in the Cox proportional hazards model. The p-value threshold for statistical significance was 0.0209.
b Based on Kaplan-Meier estimates.
c HR from a Cox proportional hazards model stratified by tumor sidedness (left vs right) per IRT.

Figure 20: Progression-free Survival (First-Line Intravenous Nivolumab + Ipilimumab vs Chemotherapy) - CHECKMATE-8HW

All lines intravenous nivolumab in combination with ipilimumab

Among 707 patients across all treatment lines who were randomly assigned to intravenous nivolumab in combination with ipilimumab (354) and to intravenous nivolumab (353) single agent, 296 and 286 patients had centrally confirmed MSI-H/dMMR status in the intravenous nivolumab in combination with ipilimumab arm and in the intravenous nivolumab arm, respectively. Patients receiving at least 1 dose of study treatment included 352 of 354 patients randomized to intravenous nivolumab in combination with ipilimumab, and 351 of 353 patients randomized to single agent intravenous nivolumab.

The BICR-assessed PFS and ORR efficacy results for patients with centrally confirmed MSI-H/dMMR randomized to the intravenous nivolumab in combination with ipilimumab compared with intravenous nivolumab single agent across all treatment lines setting are presented in Table 66 and Figure 21. The comparative results of OS between arms were not available at the time of the PFS analysis due to statistical testing strategy.

Table 66: Efficacy Results, All Lines - CHECKMATE-8HW
 | Intravenous Nivolumab and Ipilimumab (n=296) | Intravenous Nivolumab (n=286)
Progression-free Survival
Disease progression or death n (%) | 101 (34) | 136 (48)
Median (months)b (95% CI) | NR; (53.8, NE) | 39.3; (22.1, NE)
Hazard ratioc (95% CI) | 0.62 (0.48, 0.81)
p-valuea | 0.0003
Objective Response Rate (ORR)
Response Rate, n (%); (95% CI) | 209 (71%); (65, 76) | 165 (58%); (52, 63)
Complete Response Rate, n (%) | 90 (30%) | 80 (28%)
Partial Response Rate, n (%) | 119 (40%) | 85 (30%)
p-valued | 0.0011
NR: Not Reached; NE: Not Estimable.
Minimum follow-up was 16.7 months at data cutoff date 28Aug2024.
a Based on log-rank test stratified by the same factors as used in the Cox proportional hazards model. The p-value threshold for statistical significance was 0.0095.
b Based on Kaplan-Meier estimates.
c HR from a Cox proportional hazards model stratified by tumor sidedness (left vs right) and prior lines of therapy (0, 1, ≥2) per IRT.
d Based on Cochran-Mantel-Haenszel test stratified by the same factors as used in the Cox proportional hazards model. The p-value threshold for statistical significance was 0.006.

Figure 21: Progression-free Survival (All lines Intravenous Nivolumab + Ipilimumab vs Intravenous Nivolumab) - CHECKMATE-8HW

Treatment of MSI-H or dMMR mCRC after Progression Following Treatment with a Fluoropyrimidine, Oxaliplatin, and Irinotecan

The effectiveness of OPDIVO QVANTIG has been established for the treatment of microsatellite instability-high or mismatch repair deficient metastatic colorectal cancer (mCRC) that has progressed following treatment with a fluoropyrimidine, oxaliplatin, and irinotecan in adult and pediatric patients 12 years and older who weigh 30 kg or greater. Use of OPDIVO QVANTIG for this indication is supported by evidence from an adequate and well-controlled study conducted with intravenous nivolumab (CHECKMATE-142, NCT02060188), and additional pharmacokinetic and safety data that demonstrated comparable pharmacokinetics and safety profiles between OPDIVO QVANTIG and intravenous nivolumab [see Adverse Reactions (6.1) and Clinical Pharmacology (12.3)]. Below is a description of the efficacy results of the adequate and well-controlled study of intravenous nivolumab in this CRC population.

CHECKMATE-142

CHECKMATE-142 (NCT02060188) was a multicenter, non-randomized, multiple parallel-cohort, open-label trial conducted in patients with locally determined dMMR or MSI-H metastatic CRC (mCRC) who had disease progression during or after prior treatment with fluoropyrimidine‑ , oxaliplatin‑ , or irinotecan-based chemotherapy. Key eligibility criteria were at least one prior line of treatment for metastatic disease, ECOG performance status 0 or 1, and absence of the following: active brain metastases, active autoimmune disease, or medical conditions requiring systemic immunosuppression.

Patients enrolled in the single agent intravenous nivolumab MSI-H mCRC cohort received nivolumab 3 mg/kg by intravenous infusion (IV) every 2 weeks. Patients enrolled in the intravenous nivolumab and ipilimumab MSI-H mCRC cohort received nivolumab 3 mg/kg and ipilimumab 1 mg/kg intravenously every 3 weeks for 4 doses, followed by nivolumab as a single agent at a dose of 3 mg/kg as intravenous infusion every 2 weeks. Treatment in both cohorts continued until unacceptable toxicity or radiographic progression.

Tumor assessments were conducted every 6 weeks for the first 24 weeks and every 12 weeks thereafter. Efficacy outcome measures included ORR and DOR as assessed by BICR using RECIST v1.1.

A total of 74 patients were enrolled in the single-agent MSI-H mCRC intravenous nivolumab cohort. The median age was 53 years (range: 26 to 79) with 23% ≥65 years of age and 5% ≥75 years of age, 59% were male and 88% were White. Baseline ECOG performance status was 0 (43%), 1 (55%), or 3 (1.4%) and 36% were reported to have Lynch Syndrome. Across the 74 patients, 72% received prior treatment with a fluoropyrimidine, oxaliplatin, and irinotecan; 7%, 30%, 28%, 19%, and 16% received 0, 1, 2, 3, or ≥4 prior lines of therapy for metastatic disease, respectively, and 42% of patients had received an anti-EGFR antibody.

A total of 119 patients were enrolled in the intravenous nivolumab and ipilimumab MSI-H mCRC cohort. The median age was 58 years (range: 21 to 88), with 32% ≥65 years of age and 9% ≥75 years of age; 59% were male and 92% were White. Baseline ECOG performance status was 0 (45%) and 1 (55%), and 29% were reported to have Lynch Syndrome. Across the 119 patients, 69% had received prior treatment with a fluoropyrimidine, oxaliplatin, and irinotecan; 10%, 40%, 24%, and 15% received 1, 2, 3, or ≥4 prior lines of therapy for metastatic disease, respectively, and 29% had received an anti-EGFR antibody.

Efficacy results for each of these single-arm cohorts are shown in Table 67.

Table 67: Efficacy Results - CHECKMATE-142
 | Intravenous Nivolumaba; MSI-H/dMMR Cohort |  | Intravenous Nivolumab and Ipilimumabb; MSI-H/dMMR Cohort
 | All Patients (n=74) | Prior Treatment (Fluoropyrimidine, Oxaliplatin, and Irinotecan) (n=53) | All Patients (n=119) | Prior Treatment (Fluoropyrimidine, Oxaliplatin, and Irinotecan) (n=82)
Overall Response Rate per BICR; n (%) | 28 (38%) | 17 (32%) | 71 (60%) | 46 (56%)
(95% CI)c | (27, 50) | (20, 46) | (50, 69) | (45, 67)
Complete Response (%) | 8 (11%) | 5 (9%) | 17 (14%) | 11 (13%)
Partial Response (%) | 20 (27%) | 12 (23%) | 54 (45%) | 35 (43%)
Duration of Response
Proportion of responders with ≥6 months response duration | 86% | 94% | 89% | 87%
Proportion of responders with ≥12 months response duration | 82% | 88% | 77% | 74%
a Minimum follow-up 33.7 months for all patients treated with intravenous nivolumab (n=74).
b Minimum follow-up 27.5 months for all patients treated with intravenous nivolumab and ipilimumab (n=119).
c Estimated using the Clopper-Pearson method.

14.10 Hepatocellular Carcinoma

First-Line Treatment of Unresectable or Metastatic Hepatocellular Carcinoma (HCC)

The effectiveness of OPDIVO QVANTIG has been established for the treatment of hepatocellular carcinoma following treatment with intravenous nivolumab and ipilimumab combination therapy. Use of OPDIVO QVANTIG for this indication is supported by evidence from an adequate and well-controlled study conducted with intravenous nivolumab, and additional pharmacokinetic and safety data that demonstrated comparable pharmacokinetics and safety profiles between OPDIVO QVANTIG and intravenous nivolumab [see Adverse Reactions (6.1) and Clinical Pharmacology (12.3)]. Below is a description of the efficacy results of the adequate and well-controlled study of intravenous nivolumab in this hepatocellular carcinoma population.

CHECKMATE-9DW (NCT04039607) was a randomized (1:1), open-label trial in adults (18 years of age or older) with unresectable or metastatic HCC. Patients had histologically confirmed HCC, Child Pugh Class A, ECOG performance status 0 or 1, and no prior systemic therapy for advanced disease. Esophagogastroduodenoscopy was not mandated prior to enrollment. The trial excluded patients with active autoimmune disease, brain or leptomeningeal metastases, a history of hepatic encephalopathy (within 12 months of randomization), a platelet count <60,000, clinically significant ascites, medical conditions requiring systemic immunosuppression, infection with HIV, or active co-infection with hepatitis B virus (HBV) and hepatitis C virus (HCV) or HBV and hepatitis D virus (HDV).

Patients were randomized to receive either:

- Intravenous Nivolumab 1 mg/kg administered intravenously over 30 minutes in combination with ipilimumab 3 mg/kg administered intravenously over 30 minutes every 3 weeks, for a maximum of 4 doses, followed by single agent intravenous nivolumab 480 mg administered intravenously over 30 minutes every 4 weeks, or
- Investigator’s choice:
  ∘ Lenvatinib 8 mg orally daily (if body weight <60 kg) or 12 mg orally daily (if body weight ≥60 kg), or
  ∘ Sorafenib 400 mg orally twice daily

Randomization was stratified by etiology (HBV vs. HCV vs. non-viral), macrovascular invasion and/or extrahepatic spread (present or absent), and alpha-fetoprotein levels (≥400 or <400 ng/mL). Study treatment for intravenous nivolumab in combination with ipilimumab continued until disease progression, unacceptable toxicity, or up to 2 years. Patients who discontinued combination therapy because of an adverse reaction attributed to ipilimumab were permitted to continue intravenous nivolumab as a single agent. Treatment beyond RECIST 1.1 defined disease progression was permitted if the patient was clinically stable and considered to be deriving clinical benefit by the investigator. Tumor assessments were performed at baseline, after randomization at week 9 and week 16, then every 8 weeks up to 48 weeks, and then every 12 weeks thereafter until disease progression, treatment discontinuation, or initiation of subsequent therapy. The primary efficacy outcome measure was OS in all randomized patients. Additional efficacy measures included BICR-assessed ORR and DOR based on RECIST 1.1 criteria.

A total of 668 patients were randomized to receive intravenous nivolumab in combination with ipilimumab (n=335) or investigator’s choice (n=333) of lenvatinib or sorafenib. In the investigator arm, 85% and 15% of treated patients received lenvatinib or sorafenib, respectively. The trial population characteristics were median age 66 years (range: 20 to 89), with 53% ≥65 years old; 82% male; 53% White, 44% Asian, 2.2% Black; 12% Hispanic or Latino, 48% Not Hispanic or Latino, 40% not reported. Baseline ECOG performance status was 0 (71%) or 1 (29%). Thirty-four percent (34%) of patients had HBV infection, 28% had HCV infection, and 36% had no evidence of HBV or HCV infection.

Nineteen percent (19%) of patients had alcoholic liver disease and 11% had non-alcoholic fatty liver disease. The majority of patients had BCLC stage C (73%) disease at baseline, 19% had stage B, and 6% had stage A. Patients with Child-Pugh scores of 5, 6, and 7 were 77%, 20%, and 3%, respectively; 1 patient with Child Pugh 8 was enrolled. A total of 54% of patients had extrahepatic spread; 25% had macrovascular invasion; and 33% had AFP levels ≥400 µg/L.

CHECKMATE-9DW demonstrated a statistically significant improvement in OS and ORR. The minimum follow-up was 26.8 months. Efficacy results are shown in Table 68 and Figure 22.

Table 68: Efficacy Results - CHECKMATE-9DW
 | Intravenous Nivolumab 1 mg/kg and Ipilimumab (n=335) | Lenvatinib or Sorafenib (n=333)
Overall Survival
Deaths (%) | 194 (58%) | 228 (68%)
Median (months); (95% CI) | 23.7; (18.8, 29.4) | 20.6; (17.5, 22.5)
Hazard ratio; (95% CI)a | 0.79; (0.65, 0.96)
p-valueb | 0.0180
Overall Response Rate, n (%)c | 121 (36.1) | 44 (13.2)
(95% CI) | (31.0, 41.5) | (9.8, 17.3)
p-valued | <0.0001
Complete response (%) | 23 (6.9) | 6 (1.8)
Partial response (%) | 98 (29.3) | 38 (11.4)
Duration of Response (months)c
Median; (95% CI) | 30.4; (21.2, NRe) | 12.9; (10.2, 31.2)
Range | 1.5+, 36.9+ | 2.1+, 32.5+
a Based on stratified Cox proportional hazard model.
b Based on a 2-sided stratified log-rank test. Boundary for statistical significance: p-value ≤0.0257.
c Assessed by BICR using RECIST 1.1.
d Based on a 2-sided stratified Cochran-Mantel-Haenszel test. Boundary for statistical significance: p-value ≤0.025.
e NR: Not Reached
+ Censored observation.

Figure 22: Overall Survival - CHECKMATE-9DW

Previously Treated Hepatocellular Carcinoma

The effectiveness of OPDIVO QVANTIG has been established for the treatment of adult patients with unresectable or metastatic hepatocellular carcinoma (HCC) who have been previously treated with sorafenib following treatment with intravenous nivolumab and ipilimumab. Use of OPDIVO QVANTIG for this indication is supported by evidence from an adequate and well-controlled study conducted with intravenous nivolumab, and additional pharmacokinetic and safety data that demonstrated comparable pharmacokinetics and safety profiles between OPDIVO QVANTIG and intravenous nivolumab [see Adverse Reactions (6.1) and Clinical Pharmacology (12.3)]. Below is a description of the efficacy results of this adequate and well-controlled study of intravenous nivolumab in this hepatocellular carcinoma population.

CHECKMATE-040

CHECKMATE-040 (NCT01658878) was a multicenter, multiple cohort, open-label trial that evaluated the efficacy of intravenous nivolumab as a single agent and in combination with ipilimumab in patients with hepatocellular carcinoma (HCC) who progressed on or were intolerant to sorafenib. Additional eligibility criteria included histologic confirmation of HCC and Child‑Pugh Class A cirrhosis. The trial excluded patients with active autoimmune disease, brain metastasis, a history of hepatic encephalopathy, clinically significant ascites, infection with HIV, or active co‑infection with hepatitis B virus (HBV) and hepatitis C virus (HCV) or HBV and hepatitis D virus (HDV); however, patients with only active HBV or HCV were eligible.

Tumor assessments were conducted every 6 weeks for 48 weeks and then every 12 weeks thereafter. The major efficacy outcome measure was confirmed overall response rate as assessed by BICR using RECIST v1.1 and modified RECIST (mRECIST) for HCC. Duration of response was also assessed.

The efficacy of intravenous nivolumab in combination with ipilimumab was evaluated in 49 patients (Cohort 4) who received intravenous nivolumab 1 mg/kg and ipilimumab 3 mg/kg administered every 3 weeks for 4 doses, followed by single-agent intravenous nivolumab at 240 mg every 2 weeks until disease progression or unacceptable toxicity. The median age was 60 years (range: 18 to 80), 88% were male, 74% were Asian, and 25% were White. Baseline ECOG performance status was 0 (61%) or 1 (39%). Fifty-seven (57%) percent of patients had active HBV infection, 8% had active HCV infection, and 35% had no evidence of active HBV or HCV. The etiology for HCC was alcoholic liver disease in 16% and non‑alcoholic fatty liver disease in 6% of patients. Child-Pugh class and score was A5 for 82% and A6 for 18%; 80% of patients had extrahepatic spread; 35% had vascular invasion; and 51% had AFP levels ≥400 µg/L. Prior cancer treatment history included surgery (74%), radiotherapy (29%), or local treatment (59%). All patients had received prior sorafenib, of whom 10% were unable to tolerate sorafenib; 29% of patients had received 2 or more prior systemic therapies.

Efficacy results are shown in Table 69. The results for intravenous nivolumab in combination with ipilimumab in Cohort 4 are based on a minimum follow-up of 28 months.

Table 69: Efficacy Results - Cohort 4 of CHECKMATE-040
 | Intravenous Nivolumab and Ipilimumab (Cohort 4) (n=49)
Overall Response Rate per BICR,a n (%), RECIST v1.1 | 16 (33%)
(95% CI)b | (20, 48)
Complete response | 4 (8%)
Partial response | 12 (24%)
Duration of Response per BICR,a RECIST v1.1 | n=16
Range (months) | 4.6, 30.5+
Percent with duration ≥6 months | 88%
Percent with duration ≥12 months | 56%
Percent with duration ≥24 months | 31%
Overall Response Rate per BICR,a n (%), mRECIST | 17 (35%)
(95% CI)b | (22, 50)
Complete response | 6 (12%)
Partial response | 11 (22%)
a Confirmed by BICR.
b Confidence interval is based on the Clopper and Pearson method.

14.11 Esophageal Cancer

Adjuvant Treatment of Resected Esophageal or Gastroesophageal Junction Cancer

The effectiveness of OPDIVO QVANTIG has been established for the adjuvant treatment of resected esophageal or gastroesophageal junction cancer with residual pathologic disease who have received neoadjuvant chemoradiotherapy (CRT). Use of OPDIVO QVANTIG for this indication is supported by evidence from an adequate and well-controlled study conducted with intravenous nivolumab, and additional pharmacokinetic and safety data that demonstrated comparable pharmacokinetics and safety profiles between OPDIVO QVANTIG and intravenous nivolumab [see Adverse Reactions (6.1) and Clinical Pharmacology (12.3)]. Below is a description of the efficacy results of the adequate and well-controlled study of intravenous nivolumab in this esophageal or gastroesophageal junction cancer population.

CHECKMATE-577

CHECKMATE-577 (NCT02743494) was a randomized, multicenter, double-blind trial in 794 patients with completely resected (negative margins) esophageal or gastroesophageal junction cancer who had residual pathologic disease following concurrent chemoradiotherapy (CRT). Patients were randomized (2:1) to receive either nivolumab 240 mg or placebo by intravenous infusion over 30 minutes every 2 weeks for 16 weeks followed by 480 mg or placebo by intravenous infusion over 30 minutes every 4 weeks beginning at week 17. Treatment was until disease recurrence, unacceptable toxicity, or for up to 1 year in total duration. Enrollment required complete resection within 4 to 16 weeks prior to randomization. The trial excluded patients who did not receive CRT prior to surgery, had stage IV resectable disease, autoimmune disease, or any condition requiring systemic treatment with either corticosteroids (>10 mg daily prednisone or equivalent) or other immunosuppressive medications. Randomization was stratified by tumor PD-L1 status (≥1% vs. <1% or indeterminate or non-evaluable), pathologic lymph node status (positive ≥ypN1 vs. negative ypN0), and histology (squamous vs. adenocarcinoma). The major efficacy outcome measure was disease-free survival (DFS) defined as the time between the date of randomization and the date of first recurrence (local, regional, or distant from the primary resected site) or death, from any cause, whichever occurred first as assessed by the investigator prior to subsequent anti-cancer therapy. Patients on treatment underwent imaging for tumor recurrence every 12 weeks for 2 years, and a minimum of one scan every 6 to 12 months for years 3 to 5.

The trial population characteristics were: median age 62 years (range: 26 to 86), 36% were ≥65 years of age, 85% were male, 15% were Asian, 82% were White, and 1.1% were Black. Disease characteristics were AJCC Stage II (35%) or Stage III (65%) at initial diagnosis carcinoma, EC (60%) or GEJC (40%) at initial diagnosis, with pathologic positive lymph node status (58%) at study entry and histological confirmation of predominant adenocarcinoma (71%) or squamous cell carcinoma (29%). The baseline Tumor PD-L1 status ≥1% was positive for 16% of patients and negative for 72% of patients. Baseline ECOG performance status was 0 (58%) or 1 (42%).

CHECKMATE-577 demonstrated a statistically significant improvement in DFS for patients randomized to the intravenous nivolumab arm as compared with the placebo arm. DFS benefit was observed regardless of tumor PD-L1 expression and histology.

Efficacy results are shown in Table 70 and Figure 23.

Table 70: Efficacy Results - CHECKMATE-577
 | Intravenous Nivolumab (n=532) | Placebo (n=262)
Disease-free Survival
Number of events, n (%) | 241 (45%) | 155 (59%)
Median (months); (95% CI) | 22.4; (16.6, 34.0) | 11.0; (8.3, 14.3)
Hazard ratioa; (95% CI) | 0.69 (0.56, 0.85)
p-valueb | 0.0003
a Based on a stratified proportional hazards model.
b Based on a stratified log-rank test.

Figure 23: Disease-free Survival - CHECKMATE-577

First-line Treatment of Unresectable Advanced or Metastatic Esophageal Squamous Cell Carcinoma (ESCC) Whose Tumors Express PD-L1 (≥1)

The effectiveness of OPDIVO QVANTIG in combination with fluoropyrimidine- and platinum-containing chemotherapy has been established for the first-line treatment of unresectable advanced or metastatic ESCC. Use of OPDIVO QVANTIG for this indication is supported by evidence from an adequate and well-controlled study conducted with intravenous nivolumab, and additional pharmacokinetic and safety data that demonstrated comparable pharmacokinetics and safety profiles between OPDIVO QVANTIG and intravenous nivolumab [see Adverse Reactions (6.1) and Clinical Pharmacology (12.3)]. Below is a description of the efficacy results of the adequate and well-controlled study of intravenous nivolumab in this esophageal squamous cell carcinoma population.

CHECKMATE-648

CHECKMATE-648 (NCT03143153) was a randomized, active-controlled, open-label trial in patients with previously untreated unresectable advanced, recurrent or metastatic ESCC (squamous or adenosquamous histology). The trial enrolled patients whose tumor was evaluable for tumor cell (TC) PD-L1 expression [also called PD-L1 tumor proportion score (TPS)], which was evaluated using the PD-L1 IHC 28-8 pharmDx assay at a central laboratory. A retrospective scoring of a patient’s tumor PD-L1 status using Combined Positive Score (CPS), was also conducted using the PD-L1-stained tumor specimens used for randomization. Patients were not amenable to chemoradiation or surgery with curative intent. Prior treatment with curative intent was allowed if completed more than six months prior to trial enrollment. The trial excluded patients with brain metastasis that were symptomatic, had active autoimmune disease, used systemic corticosteroids or immunosuppressants, or patients at high risk of bleeding or fistula due to apparent invasion of tumor to organs adjacent to the esophageal tumor. Patients were randomized to receive one of the following treatments:

- Intravenous nivolumab 240 mg on days 1 and 15, fluorouracil 800 mg/m^2/day intravenously on days 1 through 5 (for 5 days), and cisplatin 80 mg/m^2 intravenously on day 1 (of a 4-week cycle).
- Intravenous nivolumab 3 mg/kg every 2 weeks in combination with ipilimumab 1 mg/kg every 6 weeks.
- Fluorouracil 800 mg/m^2/day intravenously on days 1 through 5 (for 5 days), and cisplatin 80 mg/m^2 intravenously on day 1 (of a 4-week cycle).

Patients received intravenous nivolumab until disease progression, unacceptable toxicity, or up to 2 years. In patients who received intravenous nivolumab in combination with chemotherapy and in whom either fluorouracil and/or cisplatin were discontinued, other components of the treatment regimen were allowed to be continued. Patients who discontinued combination therapy because of an adverse reaction attributed to ipilimumab were permitted to continue intravenous nivolumab as a single agent.

Randomization was stratified by TC PD-L1 expression (≥1% vs. <1% or indeterminate), region (East Asia vs. Rest of Asia vs. Rest of World), ECOG performance status (0 vs. 1), and number of organs with metastases (≤1 vs. ≥2). The major efficacy outcome measures were OS and BICR-assessed PFS in patients with TC PD-L1 expression ≥1%. Additional efficacy measures included OS in all randomized patients, BICR-assessed PFS in all randomized patients, and ORR assessed by BICR in TC PD-L1 expression ≥1% and in all randomized patients. The tumor assessments per RECIST v1.1 were conducted every 6 weeks up to and including week 48, then every 12 weeks thereafter.

A total of 970 patients were randomized in CHECKMATE-648 study among whom 965 and 906 patients had quantifiable TC PD-L1 expression and CPS at baseline, respectively; 85% (824/970) had tumors with PD-L1 CPS ≥1. The trial population characteristics in patients with PD-L1 CPS ≥1 were median age 63 years (range: 26 to 90), 46% were ≥65 years of age, 82% were male, 71% were Asian, 25% were White, and 1.2% were Black or African American. Patients had histological confirmation of squamous cell carcinoma (99%) or adenosquamous cell carcinoma (1.7%) in the esophagus. Baseline ECOG performance status was 0 (44.0%) or 1 (54%).

A statistically significant improvement in OS was demonstrated in patients randomized to intravenous nivolumab in combination with chemotherapy and patients randomized to intravenous nivolumab in combination with ipilimumab compared with chemotherapy. An exploratory analysis of OS in patients with PD-L1 CPS <1 showed a HR of 0.98 (95% CI 0.50, 1.95) for the comparison of intravenous nivolumab in combination with chemotherapy, and the exploratory analysis OS in patients with PD-L1 CPS <1 showed a HR of 1.0 (95% CI 0.52, 1.94) for the comparison of intravenous nivolumab in combination with ipilimumab; these results indicate that the improvement in the ITT population was primarily attributed to the results observed in the subgroup of patients with PD-L1 CPS ≥1. Efficacy results are shown in Table 71 and Figures 24 and 25.

Table 71: Efficacy Results - CHECKMATE-648
 | Intravenous Nivolumab with Cisplatin and Fluorouracil (n=158) | Intravenous Nivolumab and Ipilimumab (n=158) | Cisplatin and Fluorouracil (n=157) | Intravenous Nivolumab with Cisplatin and Fluorouracil (n=278) | Intravenous Nivolumab and Ipilimumab (n=266) | Cisplatin and Fluorouracil (n=280)
 | TC PD-L1 expression ≥1% |  |  | PD-L1 CPS ≥1
Overall Survival
Deaths (%) | 98 (62) | 106 (67) | 121 (77) | 177 (64) | 179 (67) | 205 (73)
Median (months); (95% CI) | 15.4; (11.9, 19.5) | 13.7; (11.2, 17.0) | 9.1; (7.7, 10) | 13.8; (12.0, 16.1) | 12.7; (10.9, 15.5) | 9.8; (8.8, 11.6)
Hazard ratio (95% CI)b | 0.54; (0.41, 0.71) | 0.64; (0.49, 0.84) | - | 0.69; (0.57, 0.85) | 0.76; (0.62, 0.93) | -
p-valuec | <0.0001S1 | 0.0010S2 | - | - | - | -
Progression-free Survivala
Disease progression or death (%) | 117 (74) | 123 (78) | 100 (64) | 201 (72) | 206 (77) | 184 (66)
Median (months); (95% CI) | 6.9; (5.7, 8.3) | 4.0; (2.4, 4.9) | 4.4; (2.9, 5.8) | 5.8; (5.5, 7.0) | 2.8; (2.6, 4.2) | 5.6; (4.2, 5.9)
Hazard ratio; (95% CI)b | 0.65; (0.49, 0.86) | 1.02; (0.78, 1.34) | - | 0.8; (0.7, 1.0) | 1.2; (1.0, 1.5) | -
p-valuec | 0.0023S3 | NS | - | - | - | -
Overall Response Rate, n (%)a, NT | 84 (53.2) | 56 (35.4) | 31 (19.7) | 135 (49) | 74 (28) | 76 (27)
(95% CI) | (45.1, 61.1) | (28.0, 43.4) | (13.8, 26.8) | (42.5, 54.6) | (22.5, 33.6) | (22.0, 32.8)
Complete response (%) | 26 (16.5) | 28 (17.7) | 8 (5.1) | 39 (14) | 32 (12.0) | 18 (6.4)
Partial response (%) | 58 (36.7) | 28 (17.7) | 23 (14.6) | 96 (35) | 42 (15.8) | 58 (20.7)
Duration of Response (months)a
Median; (95% CI) | 8.4; (6.9, 12.4) | 11.8; (7.1, 27.4) | 5.7; (4.4, 8.7) | 8.2; (6.7, 11.1) | 11.8; (7.1, 23.6) | 6.9; (5.7, 8.2)
Range | 1.4+, 34.6 | 1.4+, 34.5+ | 1.4+, 31.8+ | 1.4+, 35.9+ | 1.4+, 34.5+ | 1.4+, 31.8+
a Assessed by BICR.
b Based on stratified Cox proportional hazard model. Hazard ratios are reported for each intravenous nivolumab containing arm compared to chemotherapy within each analysis population.
c Based on a stratified 2-sided log-rank test.
S1, S2, S3 Significant p-value compared to stopping boundary of 0.005, 0.014, and 0.015, respectively.
NS: Not Statistically significant, NT: Not evaluated for statistical significance as per pre-specified hierarchical testing procedure.

Figure 24: Overall Survival – CHECKMATE-648

(A) OS in CPS ≥1

(B) OS in TC PD-L1 ≥1%

Figure 25: Progression-free Survival – CHECKMATE-648

(A) PFS in CPS ≥1

(B) PFS in TC PD-L1 ≥1%

Previously Treated Unresectable Advanced, Recurrent or Metastatic ESCC

The effectiveness of OPDIVO QVANTIG has been established for the treatment of unresectable advanced, recurrent, or metastatic ESCC after prior fluoropyrimidine- and platinum-based chemotherapy. Use of OPDIVO QVANTIG for this indication is supported by evidence from an adequate and well-controlled study conducted with intravenous nivolumab, and additional pharmacokinetic and safety data that demonstrated comparable pharmacokinetics and safety profiles between OPDIVO QVANTIG and intravenous nivolumab [see Adverse Reactions (6.1) and Clinical Pharmacology (12.3)]. Below is a description of the efficacy results of the adequate and well-controlled study of intravenous nivolumab in this ESCC population.

ATTRACTION-3

ATTRACTION-3 (NCT02569242) was a multicenter, randomized (1:1), active-controlled, open‑label trial in patients with unresectable advanced, recurrent, or metastatic ESCC, who were refractory or intolerant to at least one fluoropyrimidine- and platinum‑based regimen. The trial enrolled patients regardless of PD-L1 status, but tumor specimens were evaluated prospectively using the PD-L1 IHC 28-8 pharmDx assay at a central laboratory. The trial excluded patients who were refractory or intolerant to taxane therapy, had brain metastases that were symptomatic or required treatment, had autoimmune disease, used systemic corticosteroids or immunosuppressants, or had apparent tumor invasion of organs adjacent to the esophageal tumor or had stents in the esophagus or respiratory tract. Patients were randomized to receive nivolumab 240 mg by intravenous infusion over 30 minutes every 2 weeks or investigator’s choice of taxane chemotherapy consisting of docetaxel (75 mg/m^2 intravenously every 3 weeks) or paclitaxel (100 mg/m^2 intravenously once a week for 6 weeks followed by 1 week off).

Randomization was stratified by region (Japan vs. Rest of World), number of organs with metastases (≤1 vs. ≥2), and PD-L1 status (≥1% vs. <1% or indeterminate). Patients were treated until disease progression, assessed by the investigator per RECIST v1.1, or unacceptable toxicity. The tumor assessments were conducted every 6 weeks for 1 year, and every 12 weeks thereafter. The major efficacy outcome measure was OS. Additional efficacy outcome measures were ORR and PFS as assessed by the investigator using RECIST v1.1 and DOR.

A total of 419 patients were randomized; 210 to the intravenous nivolumab arm and 209 to the investigator’s choice arm (docetaxel: 31%, paclitaxel: 69%). The trial population characteristics were: median age 65 years (range: 33 to 87), 53% were ≥65 years of age, 87% were male, 96% were Asian and 4% were White. Sixty-seven percent of patients had received one prior systemic therapy regimen and 26% had received two prior systemic therapy regimens prior to enrolling in ATTRACTION‑3. Baseline ECOG performance status was 0 (50%) or 1 (50%).

ATTRACTION-3 demonstrated a statistically significant improvement in OS for patients randomized to intravenous nivolumab as compared with investigator’s choice of taxane chemotherapy. OS benefit was observed regardless of PD-L1 expression level. OS results by PD-L1 CPS level (<1 and ≥1) were not studied. The minimum follow-up was 17.6 months. Efficacy results are shown in Table 72 and Figure 26.

Table 72: Efficacy Results - ATTRACTION-3
 | Intravenous Nivolumab (n=210) | Docetaxel or Paclitaxel (n=209)
Overall Survivala
Deaths (%) | 160 (76%) | 173 (83%)
Median (months); (95% CI) | 10.9; (9.2, 13.3) | 8.4; (7.2, 9.9)
Hazard ratio (95% CI)b | 0.77 (0.62, 0.96)
p-valuec | 0.0189
Overall Response Rated | 33 (19.3) | 34 (21.5)
(95% CI) | (13.7, 26.0) | (15.4, 28.8)
Complete response (%) | 1 (0.6) | 2 (1.3)
Partial response (%) | 32 (18.7) | 32 (20.3)
Median duration of response (months); (95% CI) | 6.9; (5.4, 11.1) | 3.9; (2.8, 4.2)
p-valuee | 0.6323
Progression-free Survivala, f
Disease progression or death (%) | 187 (89) | 176 (84)
Median (months); (95% CI) | 1.7; (1.5, 2.7) | 3.4; (3.0, 4.2)
Hazard ratio (95% CI)b | 1.1 (0.9, 1.3)
a Based on ITT analysis.
b Based on a stratified proportional hazards model.
c Based on a stratified log-rank test.
d Based on Response Evaluable Set (RES) analysis, n=171 in intravenous nivolumab group and n=158 in investigator’s choice group.
e Based on stratified Cochran-Mantel-Haenszel test; p-value not significant.
f PFS not tested due to pre-specified hierarchical testing strategy.

Figure 26: Overall Survival - ATTRACTION-3

Of the 419 patients, 48% had PD-L1 positive ESCC, defined as ≥1% of tumor cells expressing PD-L1. The remaining 52% had PD-L1 negative ESCC defined as <1% of tumor cells expressing PD-L1.

In a pre-specified exploratory analysis by PD-L1 status, the hazard ratio (HR) for OS was 0.69 (95% CI: 0.51, 0.94) with median survivals of 10.9 and 8.1 months for the intravenous nivolumab and investigator’s choice arms, respectively, in the PD-L1 positive subgroup. In the PD-L1 negative subgroup, the HR for OS was 0.84 (95% CI: 0.62, 1.14) with median survivals of 10.9 and 9.3 months for the intravenous nivolumab and investigator’s choice arms, respectively.

14.12 Gastric Cancer, Gastroesophageal Junction Cancer, and Esophageal Adenocarcinoma Whose Tumors Express PD-L1 (≥1)

The effectiveness of OPDIVO QVANTIG in combination with fluoropyrimidine- and platinum-containing chemotherapy has been established for the treatment of gastric cancer, gastroesophageal junction cancer, and esophageal adenocarcinoma. Use of OPDIVO QVANTIG for this indication is supported by evidence from an adequate and well-controlled study conducted with intravenous nivolumab, and additional pharmacokinetic and safety data that demonstrated comparable pharmacokinetics and safety profiles between OPDIVO QVANTIG and intravenous nivolumab [see Adverse Reactions (6.1) and Clinical Pharmacology (12.3)]. Below is a description of the efficacy results of the adequate and well-controlled study of intravenous nivolumab in this population.

CHECKMATE-649

CHECKMATE-649 (NCT02872116) was a randomized, multicenter, open-label trial in patients (n=1581) with previously untreated advanced or metastatic gastric cancer, gastroesophageal junction cancer, and esophageal adenocarcinoma. The trial enrolled patients regardless of PD-L1 status, and tumor specimens were evaluated using the PD-L1 IHC 28-8 pharmDx assay at a central laboratory (tumor cell [TC] and Combined Positive Score [CPS]). The trial excluded patients who were known human epidermal growth factor receptor 2 (HER2) positive, or had untreated CNS metastases. Patients were randomized to receive intravenous nivolumab in combination with chemotherapy (n=789) or chemotherapy (n=792). Patients received one of the following treatments:

- Intravenous nivolumab 240 mg in combination with mFOLFOX6 (fluorouracil, leucovorin and oxaliplatin) every 2 weeks or mFOLFOX6 every 2 weeks.
- Intravenous nivolumab 360 mg in combination with CapeOX (capecitabine and oxaliplatin) every 3 weeks or CapeOX every 3 weeks.

Patients were treated until disease progression, unacceptable toxicity, or up to 2 years. In patients who received intravenous nivolumab in combination with chemotherapy and in whom chemotherapy was discontinued, intravenous nivolumab monotherapy was allowed to be given at 240 mg every 2 weeks, 360 mg every 3 weeks, or 480 mg every 4 weeks up to 2 years after treatment initiation.

Randomization was stratified by tumor cell PD-L1 status (≥1% vs. <1% or indeterminate), region (Asia vs. US vs. Rest of World), ECOG performance status (0 vs. 1), and chemotherapy regimen (mFOLFOX6 vs. CapeOX). The major efficacy outcome measures, assessed in patients with PD-L1 CPS ≥5, were PFS assessed by BICR and OS. Additional efficacy outcome measures included OS and PFS in patients with PD-L1 CPS ≥1 and in all randomized patients, and ORR and DOR as assessed by BICR in patients with PD-L1 CPS ≥1 and ≥5, and in all randomized patients. Tumor assessments were conducted per RECIST v1.1 every 6 weeks up to and including week 48, then every 12 weeks thereafter.

A total of 1581 patients were randomized in the CHECKMATE-649 study, among whom 1296 and 955 had baseline PD-L1 CPS ≥1 and CPS ≥5, respectively. The trial population characteristics in patients with PD-L1 CPS ≥1 were: median age 62 years (range: 18 to 90), 40% were ≥65 years of age, 72% were male, 23% were Asian, and 69% were White, and 1% were Black or African American. Baseline ECOG performance status was 0 (42%) or 1 (58%). Seventy percent of patients had adenocarcinoma tumors in the stomach, 17% in the gastroesophageal junction, and 13% in the esophagus.

CHECKMATE-649 demonstrated a statistically significant improvement in OS and PFS for patients with PD-L1 CPS ≥5. Statistically significant improvement in OS was also demonstrated for all randomized patients and patients with PD-L1 CPS ≥1. Exploratory analysis of OS in the CPS <1 population showed a hazard ratio of 0.85 (95% CI: 0.63, 1.15), indicating that the improvement in the ITT population was primarily attributed to the results observed in the subgroup of patients with PD-L1 CPS ≥1. The minimum follow-up was 12.1 months. Efficacy results are shown in Table 73 and Figures 27 and 28.

Table 73: Efficacy Results - CHECKMATE-649
 | Intravenous Nivolumab and mFOLFOX6 or CapeOX (n=641) | mFOLFOX6 or CapeOX (n=655) | Intravenous Nivolumab and mFOLFOX6 or CapeOX (n=473) | mFOLFOX6 or CapeOX (n=482)
 | PD-L1 CPS ≥1 |  | PD-L1 CPS ≥5
Overall Survival
Deaths (%) | 434 (68) | 492 (75) | 309 (65) | 362 (75)
Median (months); (95% CI) | 14.0; (12.6, 15.0) | 11.3; (10.6, 12.3) | 14.4; (13.1, 16.2) | 11.1; (10.0, 12.1)
Hazard ratio (95% CI)a | 0.77 (0.68, 0.88) |  | 0.71 (0.61, 0.83)
p-valueb | <0.0001 |  | <0.0001
Progression-free Survivalc
Disease progression or death (%) | 454 (70.8) | 472 (72.1) | 328 (69.3) | 350 (72.6)
Median (months); (95% CI) | 7.5; (7.0, 8.4) | 6.9; (6.1, 7.0) | 7.7; (7.0, 9.2) | 6.0; (5.6, 6.9)
Hazard ratio (95% CI)a | 0.74 (0.65, 0.85) |  | 0.68 (0.58, 0.79)
p-valueb | -e |  | <0.0001
Overall Response Rate, n (%)c,d | 314 (49) | 249 (38) | 237 (50) | 184 (38)
(95% CI) | (45, 53) | (34, 42) | (46, 55) | (34, 43)
Complete response (%) | 65 (10) | 42 (6) | 55 (12) | 34 (7)
Partial response (%) | 249 (39) | 207 (32) | 182 (38) | 150 (31)
Duration of Response (months)c,d
Median; (95% CI); Range | 8.5; (7.7, 10.3); 1.1+, 29.6+ | 6.9; (5.8, 7.6); 1.2+, 30.8+ | 9.5; (8.1, 11.9); 1.1+, 29.6+ | 6.9; (5.6, 7.9); 1.2+, 30.8+
a Based on stratified Cox proportional hazard model.
b Based on stratified log-rank test.
c Assessed by BICR.
d Based on confirmed response.
e Not evaluated for statistical significance.

Figure 27: Overall Survival (PD-L1 CPS ≥1) - CHECKMATE-649

Figure 28: Overall Survival (PD-L1 CPS ≥5) - CHECKMATE-649

An exploratory analysis of OS in the 44 patients with MSI-H tumors showed a HR of 0.37 (95% CI: 0.16, 0.87).

16 HOW SUPPLIED/STORAGE AND HANDLING

OPDIVO QVANTIG™ (nivolumab and hyaluronidase-nvhy) injection is a sterile, preservative-free, clear to opalescent and colorless to yellow solution for subcutaneous use. It is supplied as an individually packaged single-dose vial as follows:

Carton Contents | NDC
300 mg nivolumab and 5,000 units hyaluronidase per 2.5 mL (120 mg/2,000 units per mL) single-dose vial | 0003-3120-01
600 mg nivolumab and 10,000 units hyaluronidase per 5 mL (120 mg/2,000 units per mL) single-dose vial | 0003-6120-01

Store OPDIVO QVANTIG vials in a refrigerator at 2°C to 8°C (36°F to 46°F) in the original carton to protect from light.

Do not freeze or shake.

17 PATIENT COUNSELING INFORMATION

Advise the patient to read the FDA-approved patient labeling (Medication Guide).

Immune-Mediated Adverse Reactions

Inform patients of the risk of immune-mediated adverse reactions that may require corticosteroid treatment and withholding or discontinuation of OPDIVO QVANTIG, including:

- Pneumonitis: Advise patients to contact their healthcare provider immediately for any new or worsening cough, chest pain, or shortness of breath [see Warnings and Precautions (5.1)].
- Colitis: Advise patients to contact their healthcare provider immediately for diarrhea or severe abdominal pain [see Warnings and Precautions (5.1)].
- Hepatitis: Advise patients to contact their healthcare provider immediately for jaundice, severe nausea or vomiting, pain on the right side of abdomen, lethargy, or easy bruising or bleeding [see Warnings and Precautions (5.1)].
- Endocrinopathies: Advise patients to contact their healthcare provider immediately for signs or symptoms of hypophysitis, adrenal insufficiency, hypothyroidism, hyperthyroidism, and diabetes mellitus [see Warnings and Precautions (5.1)].
- Nephritis and Renal Dysfunction: Advise patients to contact their healthcare provider immediately for signs or symptoms of nephritis including decreased urine output, blood in urine, swelling in ankles, loss of appetite, and any other symptoms of renal dysfunction [see Warnings and Precautions (5.1)].
- Skin Adverse Reactions: Advise patients to contact their healthcare provider immediately for rash [see Warnings and Precautions (5.1)].
- Other immune-mediated adverse reactions:
  ∘ Advise patients that immune-mediated adverse reactions can occur and may involve any organ system, and to contact their healthcare provider immediately for any new or worsening signs or symptoms [see Warnings and Precautions (5.1)].
  ∘ Advise patients of the risk of solid organ transplant rejection and other transplant (including corneal graft) rejection. Advise patients to contact their healthcare provider immediately for signs or symptoms of organ transplant rejection and other transplant (including corneal graft) rejection [see Warnings and Precautions (5.1)].

Complications of Allogeneic HSCT

- Advise patients of potential risk of post-transplant complications [see Warnings and Precautions (5.2)].

Embryo-Fetal Toxicity

- Advise females of reproductive potential of the potential risk to a fetus and to inform their healthcare provider of a known or suspected pregnancy [see Warnings and Precautions (5.3) and Use in Specific Populations (8.1)].
- Advise females of reproductive potential to use effective contraception during treatment with OPDIVO QVANTIG and for 5 months following the last dose [see Use in Specific Populations (8.3)].

Lactation

- Advise women not to breastfeed during treatment with OPDIVO QVANTIG and for 5 months after the last dose [see Use in Specific Populations (8.2)].

Manufactured by:

Bristol-Myers Squibb Company
Princeton, NJ 08543 USA

U.S. License No. 1713

Halozyme Therapeutics, Inc.
12390 El Camino Real
San Diego, CA 92130

U.S. License No. 2187

MEDICATION GUIDE

OPDIVO QVANTIG™ (op-DEE-voh cue-VAN-tig)

(nivolumab and hyaluronidase-nvhy)

injection, for subcutaneous use

Read this Medication Guide before you start receiving OPDIVO QVANTIG and before each injection. There may be new information. If your healthcare provider prescribes OPDIVO QVANTIG in combination with cabozantinib, also read the Patient Information that comes with cabozantinib. This Medication Guide does not take the place of talking with your healthcare provider about your medical condition or your treatment.

What is the most important information I should know about OPDIVO QVANTIG?

OPDIVO QVANTIG is a medicine that may treat certain cancers by working with your immune system. OPDIVO QVANTIG can cause your immune system to attack normal organs and tissues in any area of your body and can affect the way they work. These problems can sometimes become severe or life-threatening and can lead to death. These problems may happen anytime during treatment or even after your treatment has ended. You may have more than one of these problems at the same time. Some of these problems may happen more often when OPDIVO QVANTIG is used in combination with another therapy.

Call or see your healthcare provider right away if you develop any new or worsening signs or symptoms, including:

Lung problems.

- cough

- shortness of breath

- chest pain

Intestinal problems.

- diarrhea (loose stools) or more frequent bowel movements than usual
- stools that are black, tarry, sticky, or have blood or mucus
- severe stomach-area (abdominal) pain or tenderness

Liver problems.

- yellowing of your skin or the whites of your eyes
- severe nausea or vomiting
- pain on the right side of your stomach area (abdomen)

- dark urine (tea colored)
- bleeding or bruising more easily than normal

Hormone gland problems.

- headaches that will not go away or unusual headaches
- eye sensitivity to light
- eye problems
- rapid heartbeat
- increased sweating
- extreme tiredness
- weight gain or weight loss
- feeling more hungry or thirsty than usual

- urinating more often than usual
- hair loss
- feeling cold
- constipation
- your voice gets deeper
- dizziness or fainting
- changes in mood or behavior, such as decreased sex drive, irritability, or forgetfulness

Kidney problems.

- decrease in your amount of urine
- blood in your urine

- swelling of your ankles
- loss of appetite

Skin problems.

- rash
- itching
- skin blistering or peeling
- swollen lymph nodes

- painful sores or ulcers in mouth or nose, throat, or genital area
- fever or flu-like symptoms

Problems can also happen in other organs and tissues. These are not all of the signs and symptoms of immune system problems that can happen with OPDIVO QVANTIG. Call or see your healthcare provider right away for any new or worsening signs or symptoms, which may include:

- chest pain, irregular heartbeat, shortness of breath or swelling of ankles
- confusion, sleepiness, memory problems, changes in mood or behavior, stiff neck, balance problems, tingling or numbness of the arms or legs
- double vision, blurry vision, sensitivity to light, eye pain, changes in eyesight
- persistent or severe muscle pain or weakness, muscle cramps
- low red blood cells, bruising

Rejection of a transplanted organ or tissue. Your healthcare provider should tell you what signs and symptoms you should report and monitor you depending on the type of organ or tissue transplant that you have had.

Getting medical treatment right away may help keep these problems from becoming more serious. Your healthcare provider will check you for these problems during treatment with OPDIVO QVANTIG. Your healthcare provider may treat you with corticosteroid or hormone replacement medicines. Your healthcare provider may also need to delay or completely stop treatment with OPDIVO QVANTIG, if you have severe side effects.

What is OPDIVO QVANTIG?

OPDIVO QVANTIG is a prescription medicine used to treat:

- adults with a type of kidney cancer that has spread called advanced renal cell carcinoma (RCC).
  ∘ OPDIVO QVANTIG may be used alone as a first treatment in certain people with advanced RCC, after completing combination treatment with nivolumab given into the vein (intravenous nivolumab) and ipilimumab.
  ∘ OPDIVO QVANTIG may be used in combination with cabozantinib as your first treatment when your cancer has spread (advanced RCC).
  ∘ OPDIVO QVANTIG may be used alone when your cancer has spread after treatment with other cancer medicines.
- adults and children 12 years of age and older who weigh 66 pounds (30 kg) or more with a type of skin cancer called melanoma.
  ∘ OPDIVO QVANTIG may be used alone to treat melanoma that has spread or cannot be removed by surgery (advanced melanoma).
  ∘ OPDIVO QVANTIG may be used alone to treat melanoma that has spread or cannot be removed by surgery, after completing combination treatment with intravenous nivolumab and ipilimumab.
  ∘ OPDIVO QVANTIG may be used alone to help prevent Stage IIB, Stage IIC, Stage III, or Stage IV melanoma from coming back after it has been completely removed by surgery.
- adults with a type of lung cancer called non-small cell lung cancer (NSCLC).
  ∘ OPDIVO QVANTIG may be used in combination with chemotherapy that contains platinum and another chemotherapy medicine before you have surgery for early-stage NSCLC.
  ∘ OPDIVO QVANTIG may be used in combination with chemotherapy that contains platinum and another chemotherapy medicine before you have surgery for early-stage NSCLC:
    - that does not have an abnormal EGFR or ALK gene, and
    - then OPDIVO QVANTIG may be continued alone after surgery to help prevent your lung cancer from coming back.
  ∘ OPDIVO QVANTIG may be used alone when your lung cancer:
    - has spread, and
    - you have tried chemotherapy that contains platinum, and it did not work or is no longer working.
    - If your tumor has an abnormal EGFR or ALK gene, you should have also tried an FDA-approved therapy for tumors with these abnormal genes, and it did not work or is no longer working.
- adults with head and neck cancer (squamous cell carcinoma).
  ∘ OPDIVO QVANTIG may be used alone when your head and neck cancer:
    - has come back or spread, and
    - you have tried chemotherapy that contains platinum and it did not work or is no longer working.
- adults with cancer of the lining of the urinary tract (urothelial carcinoma).
  ∘ OPDIVO QVANTIG may be used alone to help prevent cancer of the urinary tract from coming back after it was removed by surgery.
  ∘ OPDIVO QVANTIG may be used in combination with chemotherapy medicines cisplatin and gemcitabine as your first treatment when your urinary tract cancer has spread (metastatic) or cannot be removed by surgery.
  ∘ OPDIVO QVANTIG may be used alone when your urinary tract cancer has spread (locally advanced or metastatic), and:
    - you have tried chemotherapy that contains platinum, and it did not work or is no longer working, or
    - your cancer worsened within 12 months of treatment with chemotherapy that contains platinum, either before or after surgery to remove your cancer.
- adults and children 12 years of age and older who weigh 66 pounds (30 kg) or more with a type of colon or rectal cancer (colorectal cancer or CRC).
  ∘ OPDIVO QVANTIG may be used alone, after completing combination treatment with intravenous nivolumab and ipilimumab, when your colon or rectal cancer:
    - cannot be removed with surgery or has spread, and
    - is microsatellite instability-high (MSI-H) or mismatch repair deficient (dMMR).
  ∘ OPDIVO QVANTIG may be used alone when your colon or rectal cancer:
    - has spread, and
    - is MSI-H or dMMR, and
    - you have received treatment with a fluoropyrimidine, oxaliplatin, and irinotecan, and it did not work or is no longer working.
- adults with a type of liver cancer called hepatocellular carcinoma (HCC).
  ∘ OPDIVO QVANTIG may be used alone as your first treatment, after completing combination treatment with intravenous nivolumab and intravenous ipilimumab, when your liver cancer:
    - cannot be removed with surgery or has spread.
  ∘ OPDIVO QVANTIG may be used alone, after completing combination treatment with intravenous nivolumab and ipilimumab, when your liver cancer:
    - cannot be removed with surgery or has spread, and
    - you have received prior treatment with sorafenib.
- adults with cancer of the tube that connects your throat to your stomach (esophageal cancer).
  ∘ OPDIVO QVANTIG may be used alone to help prevent your esophageal or gastroesophageal junction cancer from coming back when:
    - your esophageal or gastroesophageal junction cancer has been treated with chemoradiation followed by surgery to completely remove the cancer, but
    - some cancer cells were still present in the removed tumor or lymph nodes.
  ∘ OPDIVO QVANTIG may be used in combination with chemotherapy that contains fluoropyrimidine and platinum as your first treatment when your esophageal cancer:
    - is a type called squamous cell carcinoma, and
    - cannot be removed with surgery, or has spread, and
    - your tumors are positive for PD-L1.
  ∘ OPDIVO QVANTIG may be used alone when your esophageal cancer:
    - is a type called squamous cell carcinoma, and
    - cannot be removed with surgery and has come back or spread, and
    - you have received chemotherapy that contains fluoropyrimidine and platinum.
- adults with cancer of the stomach (gastric cancer), cancer where the esophagus joins the stomach (gastroesophageal junction cancer), and a type of cancer in the esophagus called esophageal adenocarcinoma.
  ∘ OPDIVO QVANTIG may be used in combination with chemotherapy that contains fluoropyrimidine and platinum when your gastric, gastroesophageal junction, or esophageal cancer:
    - cannot be removed with surgery or has spread, and
    - your tumors are positive for PD-L1.

It is not known if OPDIVO QVANTIG is safe and effective in children younger than 12 years of age with melanoma or MSI-H or dMMR metastatic colorectal cancer.

It is not known if OPDIVO QVANTIG is safe and effective in children for the treatment of any other cancers that it is used to treat in adults.

Before receiving OPDIVO QVANTIG, tell your healthcare provider about all of your medical conditions, including if you:

- have immune system problems such as Crohn’s disease, ulcerative colitis, or lupus
- have received an organ or tissue transplant, including corneal transplant
- have received or plan to receive a stem cell transplant that uses donor stem cells (allogeneic)
- have received radiation treatment to your chest area in the past and have received other medicines that are like OPDIVO QVANTIG
- have a condition that affects your nervous system, such as myasthenia gravis or Guillain-Barré syndrome
- are pregnant or plan to become pregnant. OPDIVO QVANTIG can harm your unborn baby.
Females who are able to become pregnant:
  ∘ Your healthcare provider should do a pregnancy test before you start receiving OPDIVO QVANTIG.
  ∘ You should use an effective method of birth control during treatment and for 5 months after your last dose of OPDIVO QVANTIG. Talk to your healthcare provider about birth control methods that you can use during this time.
  ∘ Tell your healthcare provider right away if you become pregnant or think you may be pregnant during treatment with OPDIVO QVANTIG.
- are breastfeeding or plan to breastfeed. It is not known if OPDIVO QVANTIG passes into your breast milk. Do not breastfeed during treatment and for 5 months after your last dose of OPDIVO QVANTIG.

Tell your healthcare provider about all the medicines you take, including prescription and over-the-counter medicines, vitamins, and herbal supplements.

How will I receive OPDIVO QVANTIG?

- Your healthcare provider will give you OPDIVO QVANTIG as an injection under the skin, in the stomach area (abdomen) or thigh, over about 3 to 5 minutes.
- OPDIVO QVANTIG is usually given every 2, 3, or 4 weeks, depending on the dose you are receiving.
- Your healthcare provider will decide how many treatments you need.
- Your healthcare provider will do blood tests to check you for side effects.
- For a type of kidney cancer called advanced renal cell carcinoma, your healthcare provider may also prescribe you cabozantinib. Take cabozantinib exactly as your healthcare provider tells you.
- If you miss any appointments, call your healthcare provider as soon as possible to reschedule your appointment.

What are the possible side effects of OPDIVO QVANTIG?

OPDIVO QVANTIG can cause serious side effects, including:

- See “What is the most important information I should know about OPDIVO QVANTIG?”
- Complications, including graft-versus-host-disease (GVHD), in people who have received a bone marrow (stem cell) transplant that uses donor stem cells (allogeneic). These complications can be serious and can lead to death. These complications may happen if you underwent transplantation either before or after being treated with OPDIVO QVANTIG. Your healthcare provider will monitor you for signs of complications if you have an allogeneic stem cell transplant.

The most common side effects of OPDIVO QVANTIG when used alone in people with renal cell carcinoma include:

- pain in muscles, bones, and joints
- feeling tired
- itchy skin
- rash

- low thyroid hormone levels
- diarrhea
- cough
- stomach-area (abdominal) pain

The most common side effects observed with nivolumab given into the vein (intravenous nivolumab), which may be experienced with OPDIVO QVANTIG, are shown below.

The most common side effects of intravenous nivolumab when used alone include:

- feeling tired
- rash
- pain in muscles, bones, and joints
- itching
- diarrhea
- nausea

- weakness
- cough
- shortness of breath
- constipation
- decreased appetite
- back pain

- upper respiratory tract infection
- fever
- headache
- stomach-area (abdominal) pain
- vomiting
- urinary tract infection

The most common side effects of intravenous nivolumab when used in combination with cabozantinib as the first treatment for advanced RCC include:

- diarrhea
- feeling tired
- liver problems. See “What is the most important information I should know about OPDIVO QVANTIG?”
- rash, redness, pain, swelling or blisters on the palms of your hands or soles of your feet

- mouth sores
- rash
- high blood pressure
- low thyroid hormone levels
- pain in muscles, bones, and joints
- decreased appetite

- nausea
- change in the sense of taste
- stomach-area (abdominal) pain
- cough
- upper respiratory tract infection

The most common side effects of intravenous nivolumab when used in combination with platinum-containing chemotherapy and another chemotherapy medicine before having surgery for NSCLC include:

- nausea
- constipation

- feeling tired
- decreased appetite

- rash

The most common side effects of intravenous nivolumab when used in combination with cisplatin and gemcitabine to treat urothelial cancer include:

- nausea
- feeling tired
- pain in muscles, bones, and joints

- constipation
- decreased appetite
- rash

- vomiting
- numbness, pain, tingling or burning in your hands and feet

The most common side effects of intravenous nivolumab when used in combination with fluoropyrimidine and platinum-containing chemotherapy to treat esophageal cancer and gastric cancer include:

- nausea
- numbness, pain, tingling, or burning in your hands or feet
- decreased appetite

- feeling tired
- constipation
- mouth sores
- diarrhea

- vomiting
- stomach-area (abdominal) pain
- pain in muscles, bones, and joints

These are not all the possible side effects of OPDIVO QVANTIG.

Call your doctor for medical advice about side effects. You may report side effects to FDA at 1-800-FDA-1088.

General information about the safe and effective use of OPDIVO QVANTIG.

Medicines are sometimes prescribed for purposes other than those listed in a Medication Guide. You can ask your pharmacist or healthcare provider for information about OPDIVO QVANTIG that is written for health professionals.

What are the ingredients in OPDIVO QVANTIG?

Active ingredients: nivolumab and hyaluronidase-nvhy

Inactive ingredients: histidine, histidine hydrochloride monohydrate, methionine, pentetic acid, polysorbate 80, sucrose, and Water for Injection.

Manufactured by: Bristol-Myers Squibb Company, Princeton, NJ 08543 USA U.S. License No. 1713

Halozyme Therapeutics, Inc., 12390 El Camino Real, San Diego, CA 92130, U.S. License No. 2187

OPDIVO QVANTIG™ is a trademark of Bristol-Myers Squibb Company. Other brands listed are the trademarks of their respective owners.

For more information, call 1-855-673-4861 or go to www.Qvantig.com.

This Medication Guide has been approved by the U.S. Food and Drug Administration.

Revised: November 2025

OPDIVO QVANTIG™ 300 mg and 5,000 units/2.5 mL Representative Packaging

Rx Only
NDC 0003-3120-01

OPDIVO QVANTIG™
(nivolumab and hyaluronidase-nvhy)
injection

300 mg and 5,000 units/2.5 mL
(120 mg and 2,000 units/mL)
For Subcutaneous Use Only
Administer Subcutaneous
Injection Over 3 to 5 Minutes

Single-dose vial;
Discard unused portion.
ATTENTION: Dispense the
enclosed Medication Guide
to each patient.

Bristol Myers Squibb

OPDIVO QVANTIGTM 600 mg and 10,000 units/5 mL Representative Packaging

Rx Only
NDC 0003-6120-01

OPDIVO QVANTIG™
(nivolumab and hyaluronidase-nvhy)
injection

600 mg and 10,000 units/5 mL
(120mg and 2,000 units/mL)
For Subcutaneous Use Only
Administer Subcutaneous
Injection Over 3 to 5 Minutes

Single-dose vial;
Discard unused portion.
ATTENTION: Dispense the
enclosed Medication Guide
to each patient.

Bristol Myers Squibb